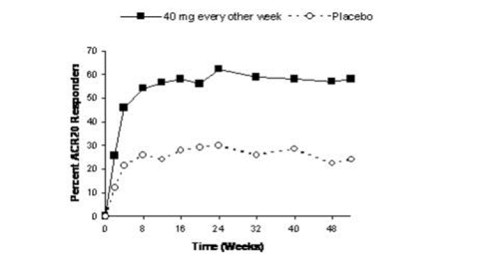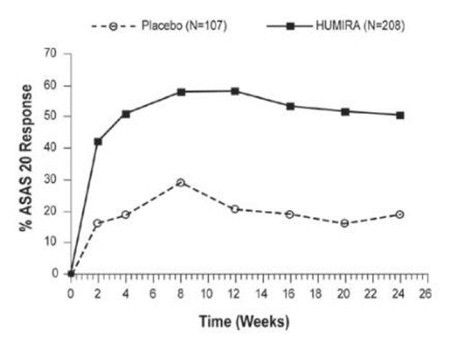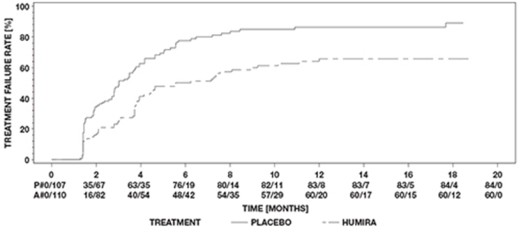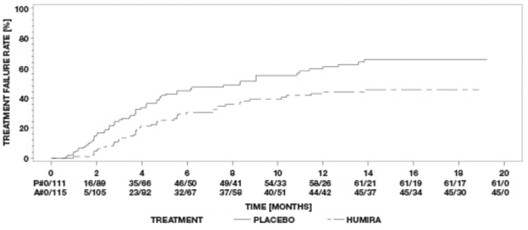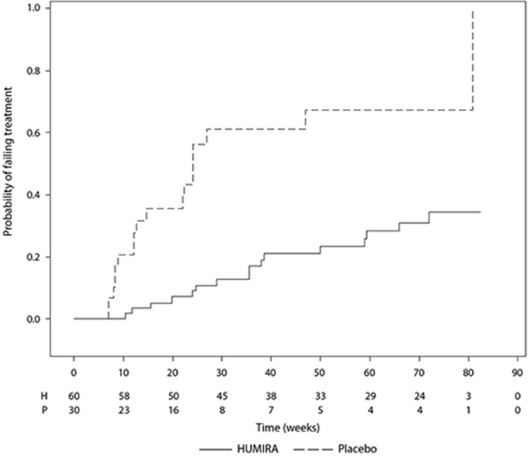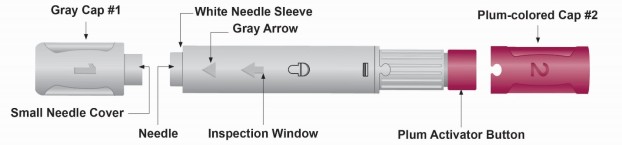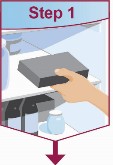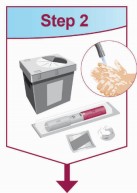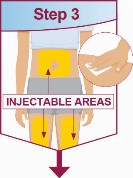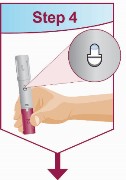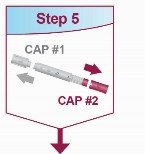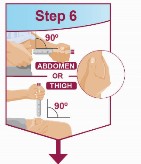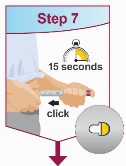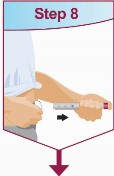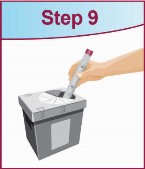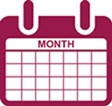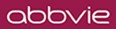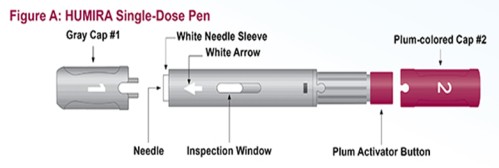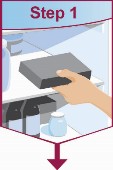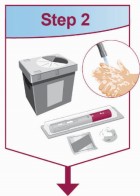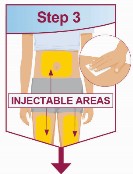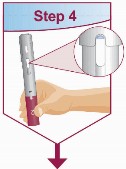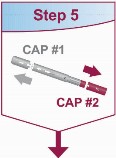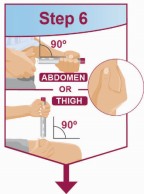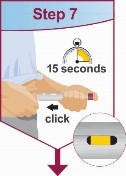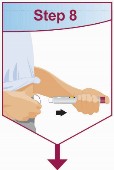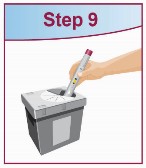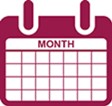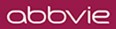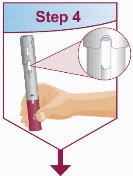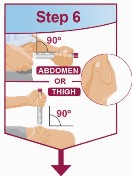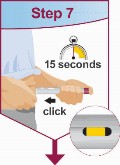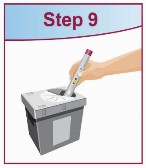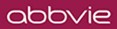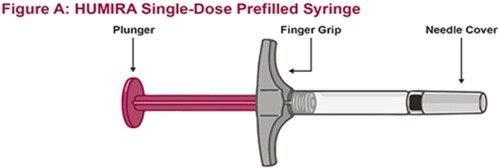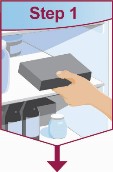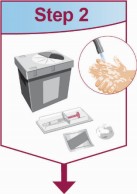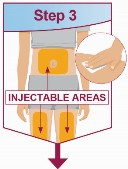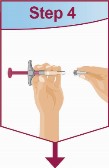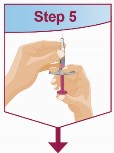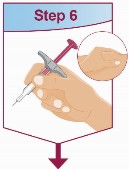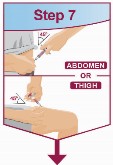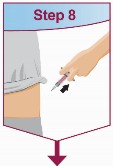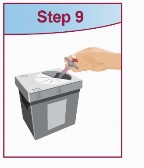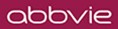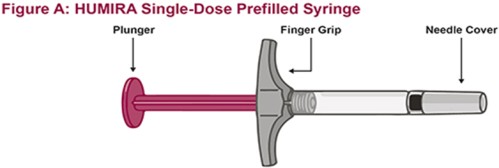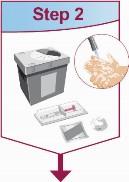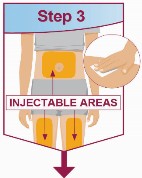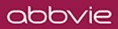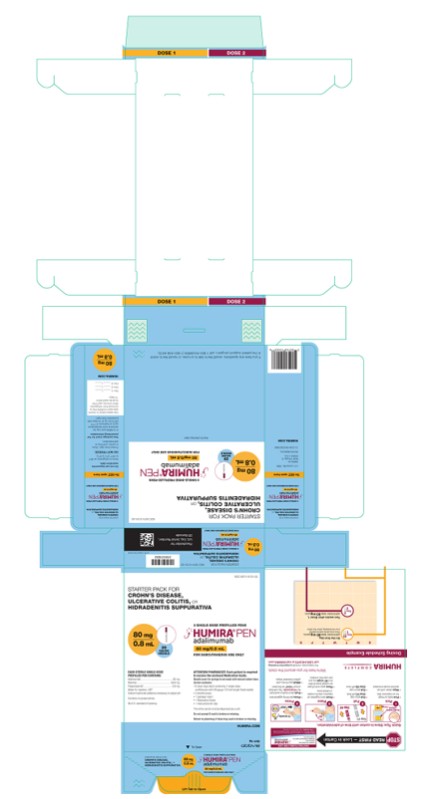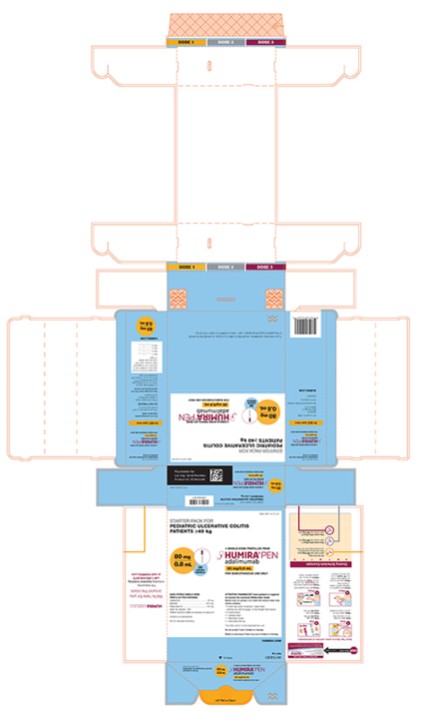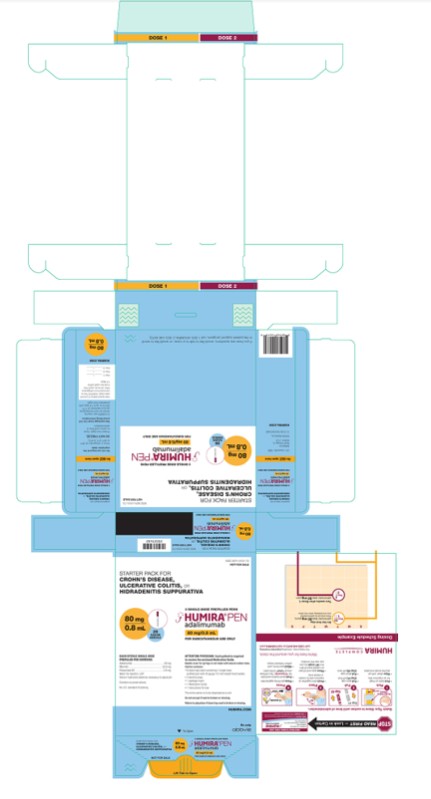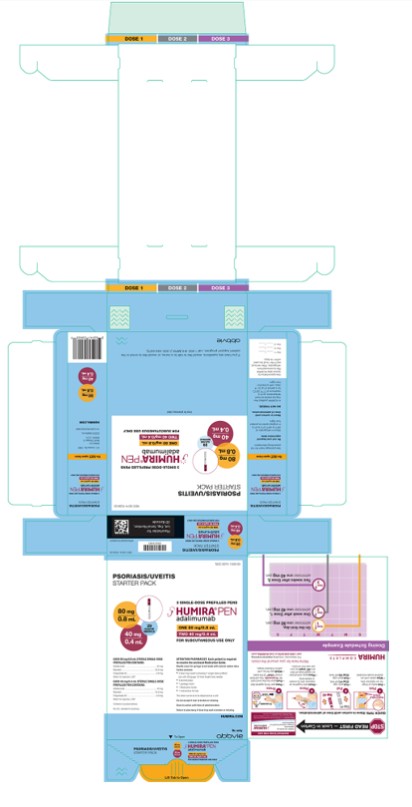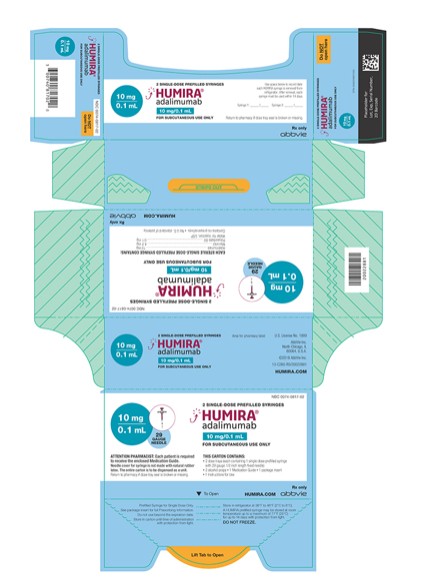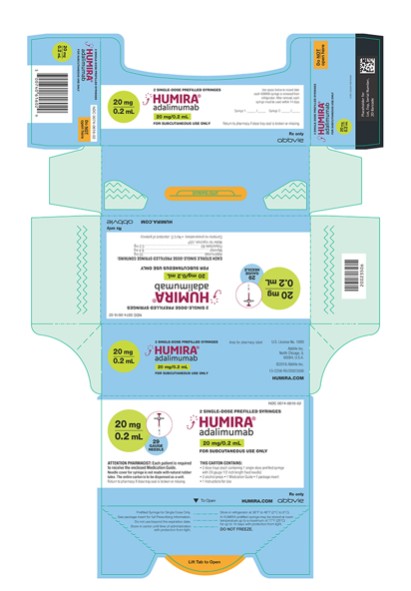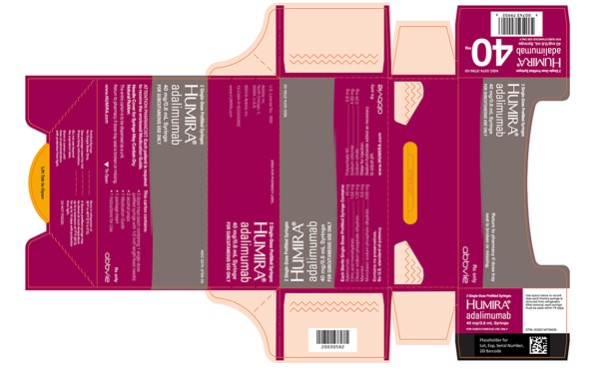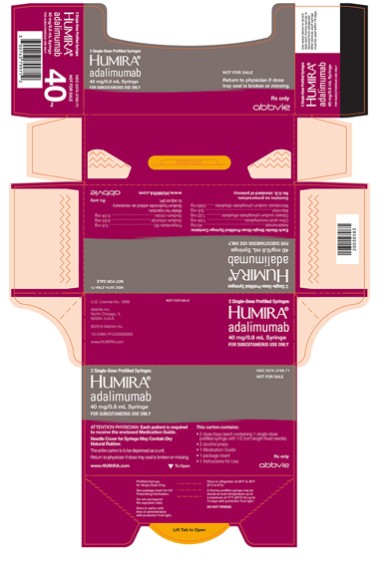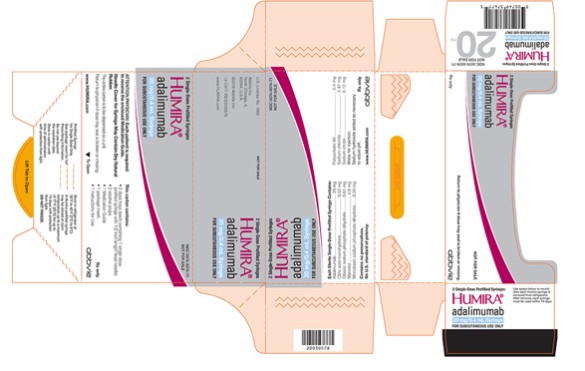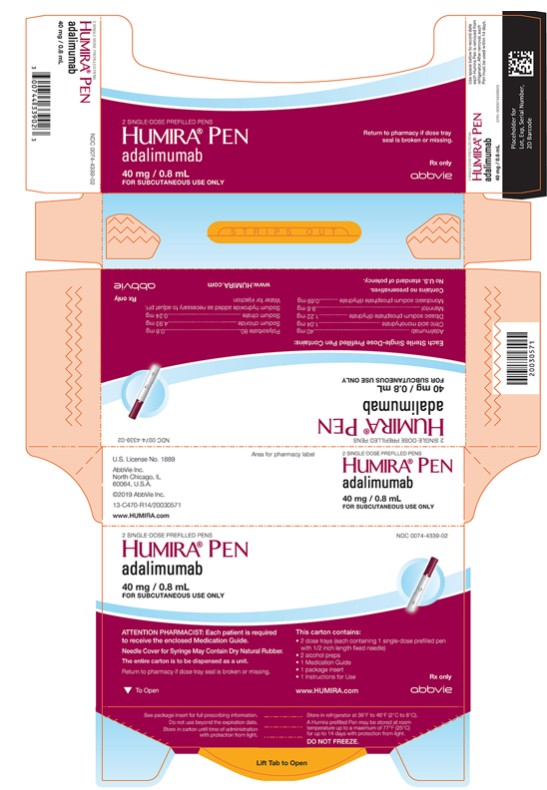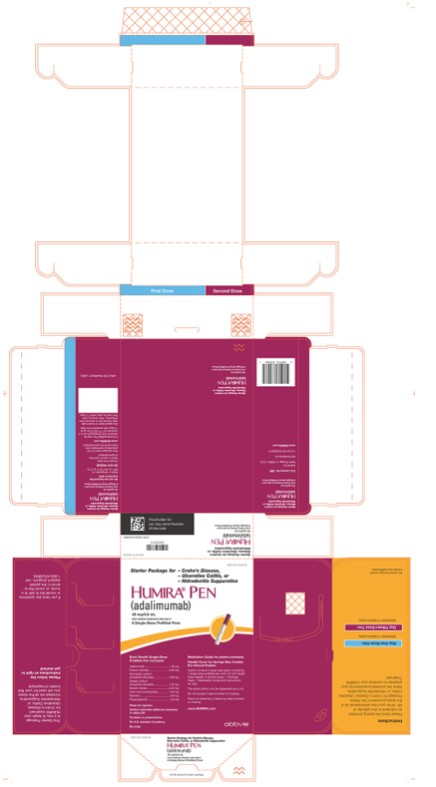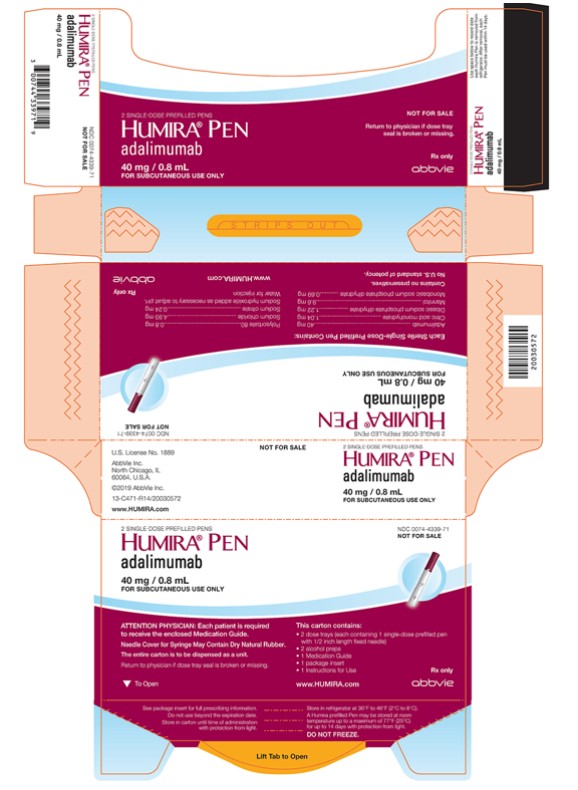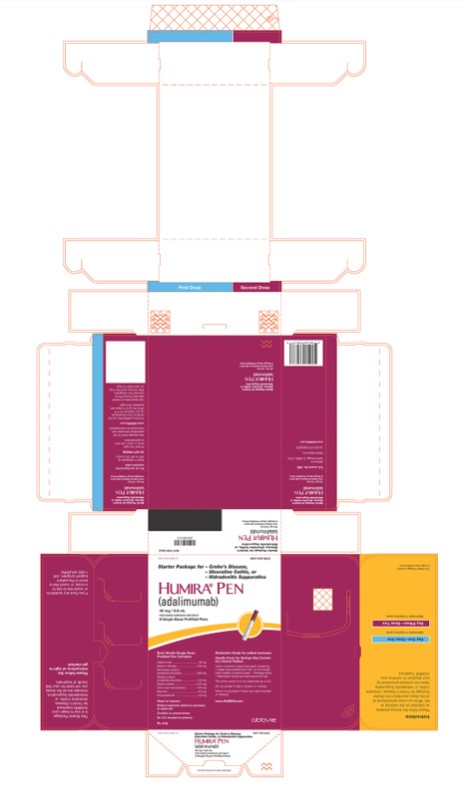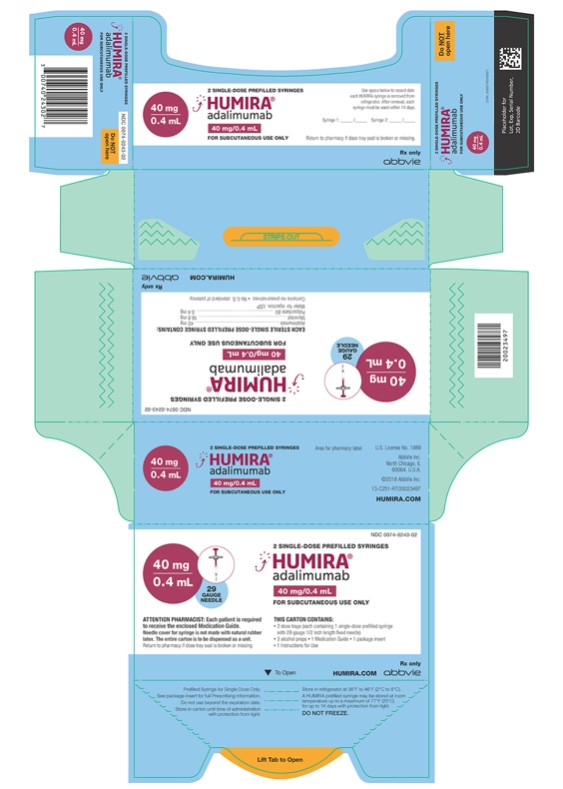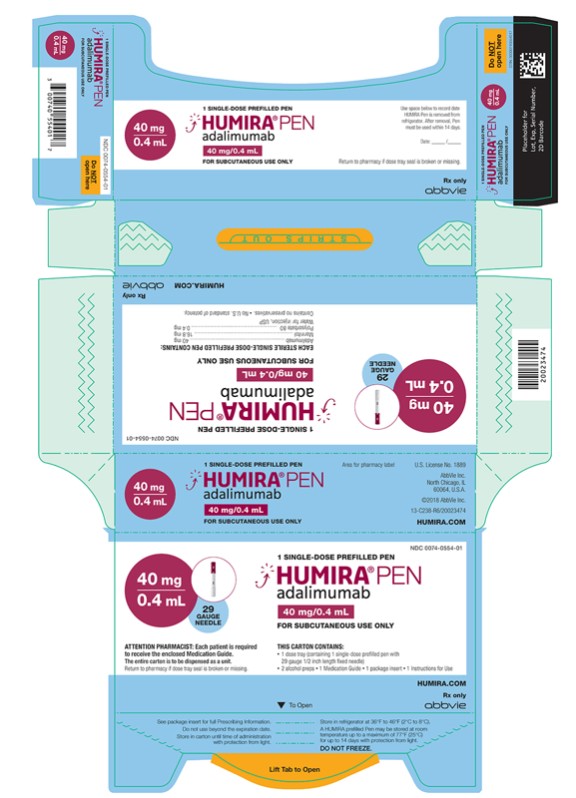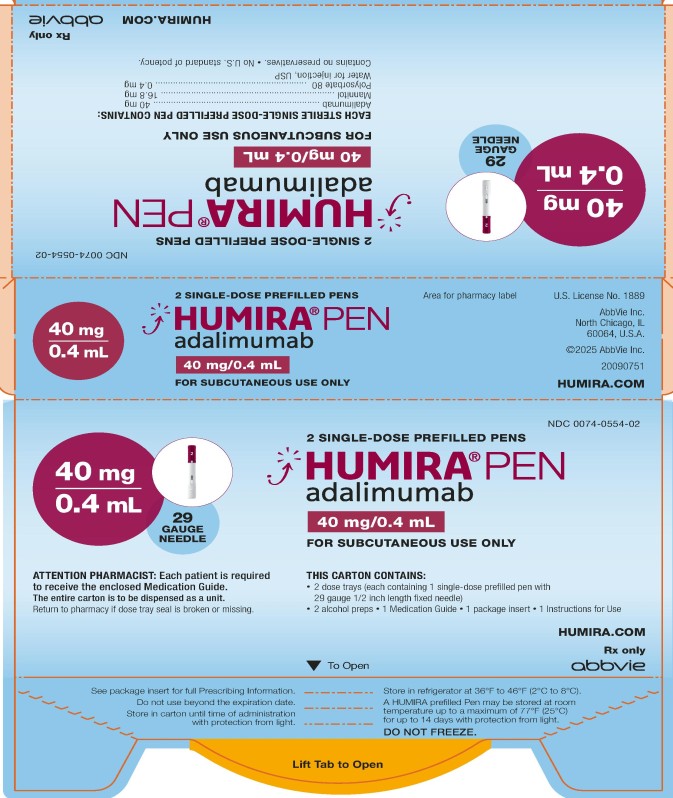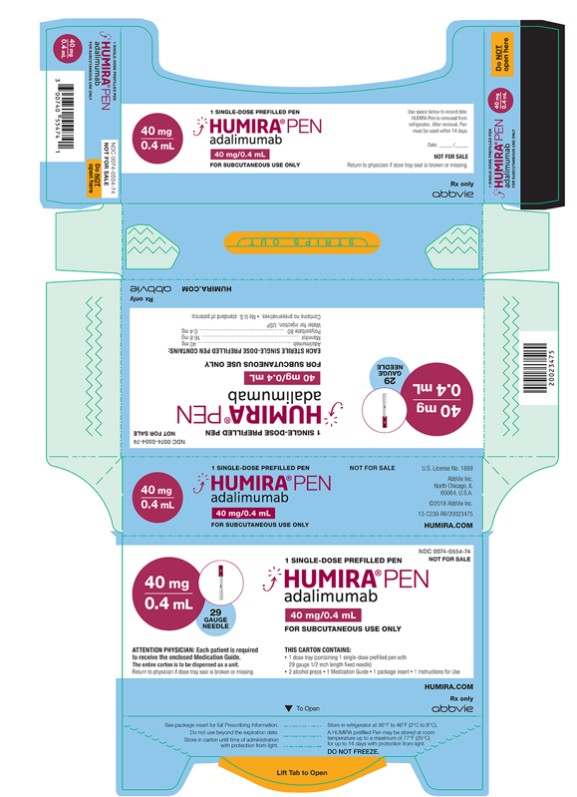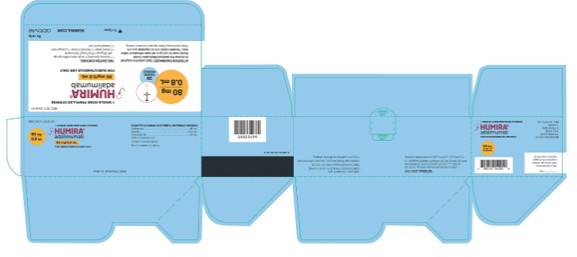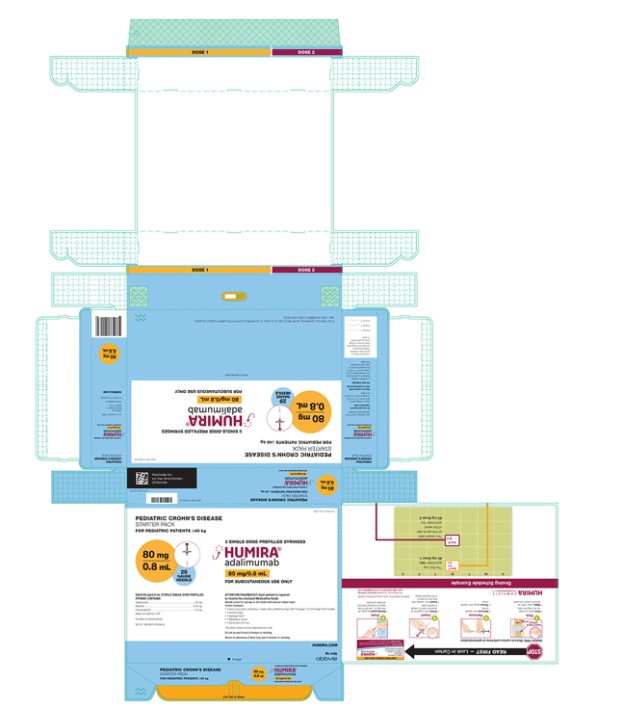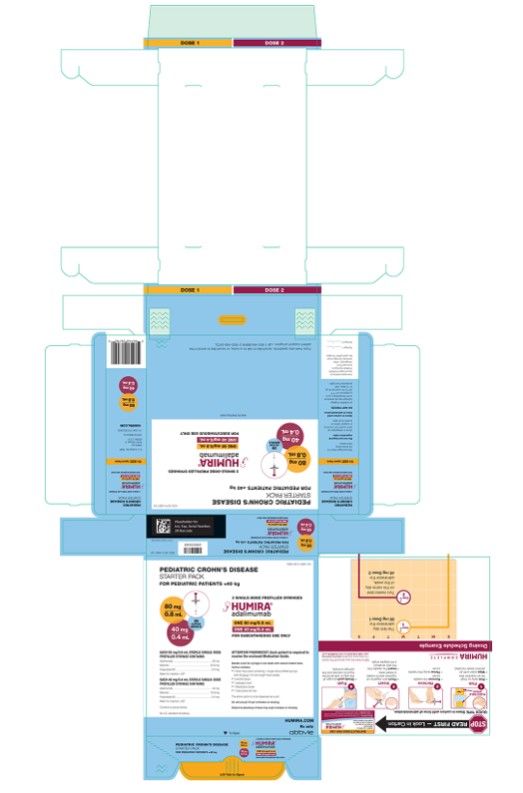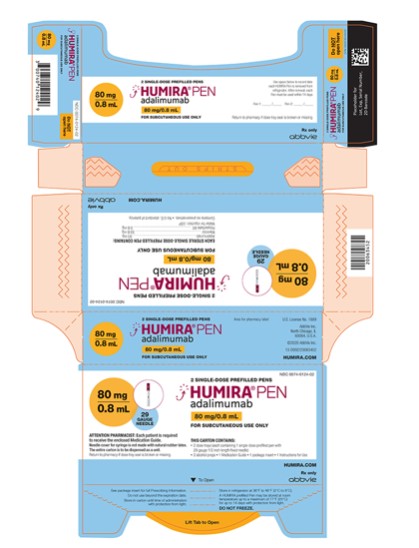 DRUG LABEL: Humira
NDC: 0074-3799 | Form: KIT | Route: SUBCUTANEOUS
Manufacturer: AbbVie Inc.
Category: prescription | Type: HUMAN PRESCRIPTION DRUG LABEL
Date: 20251223

ACTIVE INGREDIENTS: ADALIMUMAB 40 mg/0.8 mL; ISOPROPYL ALCOHOL 0.70 mL/1 mL
INACTIVE INGREDIENTS: POLYSORBATE 80 0.8 mg/0.8 mL; SODIUM PHOSPHATE, DIBASIC, DIHYDRATE 1.22 mg/0.8 mL; WATER; SODIUM HYDROXIDE; MANNITOL 9.6 mg/0.8 mL; SODIUM PHOSPHATE, MONOBASIC, DIHYDRATE 0.69 mg/0.8 mL; SODIUM CHLORIDE 4.93 mg/0.8 mL; CITRIC ACID MONOHYDRATE 1.04 mg/0.8 mL; SODIUM CITRATE, UNSPECIFIED FORM 0.24 mg/0.8 mL; WATER

HIGHLIGHTS OF PRESCRIBING INFORMATION

These highlights do not include all the information needed to use HUMIRA safely and effectively. See full prescribing information for HUMIRA.
HUMIRA® (adalimumab) injection, for subcutaneous use
Initial U.S. Approval: 2002

RECENT MAJOR CHANGES

Warnings and Precautions, Autoimmunity (5.9) | 7/2025

WARNING: SERIOUS INFECTIONS AND MALIGNANCY

See full prescribing information for complete boxed warning.

SERIOUS INFECTIONS (5.1, 6.1):

- Increased risk of serious infections leading to hospitalization or death, including tuberculosis (TB), bacterial sepsis, invasive fungal infections (such as histoplasmosis), and infections due to other opportunistic pathogens.
- Discontinue HUMIRA if a patient develops a serious infection or sepsis during treatment.
- Perform test for latent TB; if positive, start treatment for TB prior to starting HUMIRA.
- Monitor all patients for active TB during treatment, even if initial latent TB test is negative.

MALIGNANCY (5.2):

- Lymphoma and other malignancies, some fatal, have been reported in children and adolescent patients treated with TNF blockers including HUMIRA.
- Post-marketing cases of hepatosplenic T-cell lymphoma (HSTCL), a rare type of T-cell lymphoma, have occurred in adolescent and young adults with inflammatory bowel disease treated with TNF blockers including HUMIRA.

1 INDICATIONS AND USAGE

HUMIRA is a tumor necrosis factor (TNF) blocker indicated for:

- Reducing signs and symptoms, inducing major clinical response, inhibiting the progression of structural damage, and improving physical function in adult patients with moderately to severely active rheumatoid arthritis. (1.1)
- Reducing signs and symptoms of moderately to severely active polyarticular juvenile idiopathic arthritis in patients 2 years of age and older. (1.2)
- Reducing signs and symptoms, inhibiting the progression of structural damage, and improving physical function in adult patients with active psoriatic arthritis. (1.3)
- Reducing signs and symptoms in adult patients with active ankylosing spondylitis. (1.4)
- Treatment of moderately to severely active Crohn’s disease in adults and pediatric patients 6 years of age and older. (1.5)
- Treatment of moderately to severely active ulcerative colitis in adults and pediatric patients 5 years of age and older. (1.6)
  Limitations of Use: Effectiveness has not been established in patients who have lost response to or were intolerant to TNF blockers.
- Treatment of adult patients with moderate to severe chronic plaque psoriasis who are candidates for systemic therapy or phototherapy, and when other systemic therapies are medically less appropriate. (1.7)
- Treatment of moderate to severe hidradenitis suppurativa in patients 12 years of age and older. (1.8)
- Treatment of non-infectious intermediate, posterior, and panuveitis in adults and pediatric patients 2 years of age and older. (1.9)

2 DOSAGE AND ADMINISTRATION

- Administer by subcutaneous injection (2)

Rheumatoid Arthritis, Psoriatic Arthritis, Ankylosing Spondylitis (2.1):

- Adults: 40 mg every other week.
  • Some patients with RA not receiving methotrexate may benefit from increasing the dosage to 40 mg every week or 80 mg every other week.

Juvenile Idiopathic Arthritis or Pediatric Uveitis (2.2):

Pediatric Weight 2 Years of Age and Older | Recommended Dosage
10 kg (22 lbs) to less than 15 kg (33 lbs) | 10 mg every other week
15 kg (33 lbs) to less than 30 kg (66 lbs) | 20 mg every other week
30 kg (66 lbs) and greater | 40 mg every other week

Crohn's Disease (2.3):

- Adults: 160 mg on Day 1 (given in one day or split over two consecutive days); 80 mg on Day 15; and 40 mg every other week starting on Day 29.
- Pediatric Patients 6 Years of Age and Older:

Pediatric Weight | Recommended Dosage
 | Days 1 and 15 | Starting on Day 29
17 kg (37 lbs) to less than 40 kg (88 lbs) | Day 1: 80 mg Day 15: 40 mg | 20 mg every other week
40 kg (88 lbs) and greater | Day 1: 160 mg (single dose or split over two consecutive days) Day 15: 80 mg | 40 mg every other week

Ulcerative Colitis (2.4):

- Adults: 160 mg on Day 1 (given in one day or split over two consecutive days), 80 mg on Day 15 and 40 mg every other week starting on Day 29. Discontinue in patients without evidence of clinical remission by eight weeks (Day 57).
- Pediatric Patients 5 Years of Age and Older:

Pediatric Weight | Recommended Dosage
 | Days 1 through 15 | Starting on Day 29*
20 kg (44 lbs) to less than 40 kg (88 lbs) | Day 1: 80 mg Day 8: 40 mg Day 15: 40 mg | 40 mg every other week or 20 mg every week
40 kg (88 lbs) and greater | Day 1: 160 mg (single dose or split over two consecutive days) Day 8: 80 mg Day 15: 80 mg | 80 mg every other week or 40 mg every week
* Continue the recommended pediatric dosage in patients who turn 18 years of age and who are well-controlled on their HUMIRA regimen.

Plaque Psoriasis or Adult Uveitis (2.5):

- Adults: 80 mg initial dose, followed by 40 mg every other week starting one week after initial dose.

Hidradenitis Suppurativa (2.6):

- Adults:
  ○ Day 1: 160 mg (given in one day or split over two consecutive days)
  ○ Day 15: 80 mg
  ○ Day 29 and subsequent doses: 40 mg every week or 80 mg every other week
- Adolescents 12 years of age and older:

Adolescent Weight | Recommended Dosage
30 kg (66 lbs) to less than 60 kg (132 lbs) | Day 1: 80 mg Day 8 and subsequent doses: 40 mg every other week
60 kg (132 lbs) and greater | Day 1: 160 mg (given in one day or split over two consecutive days) Day 15: 80 mg Day 29 and subsequent doses: 40 mg every week or 80 mg every other week

3 DOSAGE FORMS AND STRENGTHS

Injection:

- Single-dose prefilled pen (HUMIRA Pen): 80 mg/0.8 mL, 40 mg/0.8 mL, and 40 mg/0.4 mL (3)
- Single-dose prefilled glass syringe: 80 mg/0.8 mL, 40 mg/0.8 mL, 40 mg/0.4 mL, 20 mg/0.2 mL, 10 mg/0.1 mL (3)

4 CONTRAINDICATIONS

None (4)

5 WARNINGS AND PRECAUTIONS

- Serious infections: Do not start HUMIRA during an active infection. If an infection develops, monitor carefully, and stop HUMIRA if infection becomes serious. (5.1)
- Invasive fungal infections: For patients who develop a systemic illness on HUMIRA, consider empiric antifungal therapy for those who reside or travel to regions where mycoses are endemic. (5.1)
- Malignancies: Incidence of malignancies was greater in HUMIRA-treated patients than in controls (5.2)
- Anaphylaxis or serious hypersensitivity reactions may occur (5.3)
- Hepatitis B virus reactivation: Monitor HBV carriers during and several months after therapy. If reactivation occurs, stop HUMIRA and begin anti-viral therapy. (5.4)
- Demyelinating disease: Exacerbation or new onset, may occur. (5.5)
- Cytopenias, pancytopenia: Advise patients to seek immediate medical attention if symptoms develop, and consider stopping HUMIRA. (5.6)
- Heart failure: Worsening or new onset, may occur. (5.8)
- Autoimmunity: Stop HUMIRA if lupus-like syndrome or autoimmune hepatitis develops. (5.9)

6 ADVERSE REACTIONS

Most common adverse reactions (>10%) are: infections (e.g. upper respiratory, sinusitis), injection site reactions, headache and rash. (6.1)

To report SUSPECTED ADVERSE REACTIONS, contact AbbVie Inc. at 1-800-633-9110 or FDA at 1-800-FDA-1088 or www.fda.gov/medwatch

7 DRUG INTERACTIONS

- Abatacept: Increased risk of serious infection. (5.1, 5.11, 7.2)
- Anakinra: Increased risk of serious infection. (5.1, 5.7, 7.2)
- Live vaccines: Avoid use with HUMIRA. (5.10, 7.3)

FULL PRESCRIBING INFORMATION

WARNING: SERIOUS INFECTIONS AND MALIGNANCY

SERIOUS INFECTIONS

Patients treated with HUMIRA are at increased risk for developing serious infections that may lead to hospitalization or death [see Warnings and Precautions (5.1)]. Most patients who developed these infections were taking concomitant immunosuppressants such as methotrexate or corticosteroids.

Discontinue HUMIRA if a patient develops a serious infection or sepsis.

Reported infections include:

● Active tuberculosis (TB), including reactivation of latent TB. Patients with TB have frequently presented with disseminated or extrapulmonary disease. Test patients for latent TB before HUMIRA use and during therapy. Initiate treatment for latent TB prior to HUMIRA use.

● Invasive fungal infections, including histoplasmosis, coccidioidomycosis, candidiasis, aspergillosis, blastomycosis, and pneumocystosis. Patients with histoplasmosis or other invasive fungal infections may present with disseminated, rather than localized, disease. Antigen and antibody testing for histoplasmosis may be negative in some patients with active infection. Consider empiric anti-fungal therapy in patients at risk for invasive fungal infections who develop severe systemic illness.

● Bacterial, viral and other infections due to opportunistic pathogens, including Legionella and Listeria.

Carefully consider the risks and benefits of treatment with HUMIRA prior to initiating therapy in patients with chronic or recurrent infection.

Monitor patients closely for the development of signs and symptoms of infection during and after treatment with HUMIRA, including the possible development of TB in patients who tested negative for latent TB infection prior to initiating therapy [see Warnings and Precautions (5.1) and Adverse Reactions (6.1)].

MALIGNANCY

Lymphoma and other malignancies, some fatal, have been reported in children and adolescent patients treated with TNF blockers including HUMIRA [see Warnings and Precautions (5.2)]. Post-marketing cases of hepatosplenic T-cell lymphoma (HSTCL), a rare type of T-cell lymphoma, have been reported in patients treated with TNF blockers including HUMIRA. These cases have had a very aggressive disease course and have been fatal. The majority of reported TNF blocker cases have occurred in patients with Crohn's disease or ulcerative colitis and the majority were in adolescent and young adult males. Almost all these patients had received treatment with azathioprine or 6-mercaptopurine (6–MP) concomitantly with a TNF blocker at or prior to diagnosis. It is uncertain whether the occurrence of HSTCL is related to use of a TNF blocker or a TNF blocker in combination with these other immunosuppressants [see Warnings and Precautions (5.2)].

1 INDICATIONS AND USAGE

1.1 Rheumatoid Arthritis

HUMIRA is indicated for reducing signs and symptoms, inducing major clinical response, inhibiting the progression of structural damage, and improving physical function in adult patients with moderately to severely active rheumatoid arthritis. HUMIRA can be used alone or in combination with methotrexate or other non-biologic disease-modifying anti-rheumatic drugs (DMARDs).

1.2 Juvenile Idiopathic Arthritis

HUMIRA is indicated for reducing signs and symptoms of moderately to severely active polyarticular juvenile idiopathic arthritis in patients 2 years of age and older. HUMIRA can be used alone or in combination with methotrexate.

1.3 Psoriatic Arthritis

HUMIRA is indicated for reducing signs and symptoms, inhibiting the progression of structural damage, and improving physical function in adult patients with active psoriatic arthritis. HUMIRA can be used alone or in combination with non-biologic DMARDs.

1.4 Ankylosing Spondylitis

HUMIRA is indicated for reducing signs and symptoms in adult patients with active ankylosing spondylitis.

1.5 Crohn’s Disease

HUMIRA is indicated for the treatment of moderately to severely active Crohn’s disease in adults and pediatric patients 6 years of age and older.

1.6 Ulcerative Colitis

HUMIRA is indicated for the treatment of moderately to severely active ulcerative colitis in adults and pediatric patients 5 years of age and older.

Limitations of Use
The effectiveness of HUMIRA has not been established in patients who have lost response to or were intolerant to TNF blockers [see Clinical Studies (14.7, 14.8)].

1.7 Plaque Psoriasis

HUMIRA is indicated for the treatment of adult patients with moderate to severe chronic plaque psoriasis who are candidates for systemic therapy or phototherapy, and when other systemic therapies are medically less appropriate. HUMIRA should only be administered to patients who will be closely monitored and have regular follow-up visits with a physician [see Warnings and Precautions (5)].

1.8 Hidradenitis Suppurativa

HUMIRA is indicated for the treatment of moderate to severe hidradenitis suppurativa in patients 12 years of age and older.

1.9 Uveitis

HUMIRA is indicated for the treatment of non-infectious intermediate, posterior, and panuveitis in adults and pediatric patients 2 years of age and older.

2 DOSAGE AND ADMINISTRATION

2.1 Recommended Tuberculosis Evaluation

Prior to initiating HUMIRA and periodically during therapy, evaluate patients for active tuberculosis and test for latent infection [see Warnings and Precautions (5.1)].

2.2 Recommended Dosage in Rheumatoid Arthritis, Psoriatic Arthritis, and Ankylosing Spondylitis

The recommended subcutaneous dosage of HUMIRA for adult patients with rheumatoid arthritis (RA), psoriatic arthritis (PsA), or ankylosing spondylitis (AS) [see Indication and Usage (1.1, 1.3, 1.4)] is 40 mg administered every other week. Methotrexate (MTX), other non-biologic DMARDS, glucocorticoids, nonsteroidal anti-inflammatory drugs (NSAIDs), and/or analgesics may be continued during treatment with HUMIRA. In the treatment of RA, some patients not taking concomitant MTX may derive additional benefit from increasing the dosage of HUMIRA to 40 mg every week or 80 mg every other week.

2.3 Recommended Dosage in Juvenile Idiopathic Arthritis or Pediatric Patients with Uveitis

The recommended subcutaneous dosage of HUMIRA for pediatric patients 2 years of age and older with polyarticular juvenile idiopathic arthritis (JIA) or pediatric uveitis [see Indications and Usage (1.2, 1.9)], based on weight, is shown below. MTX, glucocorticoids, NSAIDs, and/or analgesics may be continued during treatment with HUMIRA.

Pediatric Weight (2 Years of Age and older) | Recommended Dosage
10 kg (22 lbs) to less than 15 kg (33 lbs) | 10 mg every other week
15 kg (33 lbs) to less than 30 kg (66 lbs) | 20 mg every other week
30 kg (66 lbs) and greater | 40 mg every other week

HUMIRA has not been studied in patients with polyarticular JIA or pediatric uveitis less than 2 years of age or in patients with a weight below 10 kg.

2.4 Recommended Dosage in Crohn’s Disease

Subcutaneous Adult Dosage Regimen

The recommended subcutaneous dosage of HUMIRA for adult patients with moderately to severely active Crohn’s disease (CD) is 160 mg initially on Day 1 (given in one day or split over two consecutive days), followed by 80 mg two weeks later (Day 15). Two weeks later (Day 29) begin a dosage of 40 mg every other week. Aminosalicylates and/or corticosteroids may be continued during treatment with HUMIRA. Azathioprine, 6-mercaptopurine (6-MP) [see Warnings and Precautions (5.2)] or MTX may be continued during treatment with HUMIRA if necessary.

Subcutaneous Pediatric Dosage Regimen

The recommended subcutaneous dosage of HUMIRA for pediatric patients 6 years of age and older with moderately to severely active Crohn’s disease (CD), based on body weight, is shown below:

Pediatric Weight | Recommended Dosage
 | Days 1 through 15 | Starting on Day 29
17 kg (37 lbs) to less than 40 kg (88 lbs) | Day 1: 80 mg Day 15: 40 mg | 20 mg every other week
40 kg (88 lbs) and greater | Day 1: 160 mg (single dose or split over two consecutive days) Day 15: 80 mg | 40 mg every other week

2.5 Recommended Dosage in Ulcerative Colitis

Subcutaneous Adult Dosage Regimen

The recommended subcutaneous dosage of HUMIRA for adult patients with moderately to severely active ulcerative colitis is 160 mg initially on Day 1 (given in one day or split over two consecutive days), followed by 80 mg two weeks later (Day 15). Two weeks later (Day 29) continue with a dosage of 40 mg every other week.

Discontinue HUMIRA in adult patients without evidence of clinical remission by eight weeks (Day 57) of therapy. Aminosalicylates and/or corticosteroids may be continued during treatment with HUMIRA. Azathioprine and 6-mercaptopurine (6-MP) [see Warnings and Precautions (5.2)] may be continued during treatment with HUMIRA if necessary.

Subcutaneous Pediatric Dosage Regimen

The recommended subcutaneous dosage of HUMIRA for pediatric patients 5 years of age and older with moderately to severely active ulcerative colitis, based on body weight, is shown below:

Pediatric Weight | Recommended Dosage
 | Days 1 through 15 | Starting on Day 29*
20 kg (44 lbs) to less than 40 kg (88 lbs) | Day 1: 80 mg Day 8: 40 mg Day 15: 40 mg | 40 mg every other week or 20 mg every week
40 kg (88 lbs) and greater | Day 1: 160 mg (single dose or split over two consecutive days) Day 8: 80 mg Day 15: 80 mg | 80 mg every other week or 40 mg every week
* Continue the recommended pediatric dosage in patients who turn 18 years of age and who are well-controlled on their HUMIRA regimen.

2.6 Recommended Dosage in Plaque Psoriasis or Adults with Uveitis

The recommended subcutaneous dosage of HUMIRA for adult patients with plaque psoriasis (Ps) or uveitis (UV) [see Indications and Usage (1.7, 1.9)] is an initial dose of 80 mg, followed by 40 mg given every other week starting one week after the initial dose. The use of HUMIRA in moderate to severe chronic Ps beyond one year has not been evaluated in controlled clinical studies.

2.7 Recommended Dosage in Hidradenitis Suppurativa

Subcutaneous Adult Dosage Regimen

The recommended subcutaneous dosage of HUMIRA for adult patients with moderate to severe hidradenitis suppurativa (HS) is an initial dose of 160 mg (given in one day or split over two consecutive days), followed by 80 mg two weeks later (Day 15). Begin 40 mg weekly or 80 mg every other week dosing two weeks later (Day 29).

Subcutaneous Pediatric Dosage Regimen

The recommended subcutaneous dosage of HUMIRA for pediatric patients 12 years of age and older weighing at least 30 kg with moderate to severe hidradenitis suppurativa (HS), based on body weight, is shown below [see Use in Specific Populations (8.4) and Clinical Pharmacology (12.3)]:

Body Weight of Pediatric Patients (12 years of age and older) | Recommended Dosage
30 kg (66 lbs) to less than 60 kg (132 lbs) | - Day 1: 80 mg - Day 8 and subsequent doses: 40 mg every other week
60 kg (132 lbs) and greater | - Day 1: 160 mg (given in one day or split over two consecutive days); - Day 15: 80 mg - Day 29 and subsequent doses: 40 mg every week or 80 mg every other week

2.8 General Considerations for Administration

HUMIRA is intended for use under the guidance and supervision of a physician. A patient may self-inject HUMIRA or a caregiver may inject HUMIRA using either the HUMIRA Pen or prefilled syringe if a physician determines that it is appropriate, and with medical follow-up, as necessary, after proper training in subcutaneous injection technique.

HUMIRA can be taken out of the refrigerator for 15 to 30 minutes before injecting to allow the liquid to come to room temperature. Do not remove the cap or cover while allowing it to reach room temperature. Carefully inspect the solution in the HUMIRA Pen or prefilled syringe for particulate matter and discoloration prior to subcutaneous administration. If particulates and discolorations are noted, do not use the product. HUMIRA does not contain preservatives; therefore, discard unused portions of drug remaining from the syringe. NOTE: Instruct patients sensitive to latex not to handle the needle cover of the HUMIRA 40 mg/0.8 mL Pen and 40 mg/0.8 mL prefilled syringe because it may contain natural rubber latex [see How Supplied/Storage and Handling (16)].

Instruct patients using the HUMIRA Pen or prefilled syringe to inject the full amount in the syringe, according to the directions provided in the Instructions for Use [see Instructions for Use].

Injections should occur at separate sites in the thigh or abdomen. Rotate injection sites and do not give injections into areas where the skin is tender, bruised, red or hard.

If a dose is missed, administer the dose as soon as possible. Thereafter, resume dosing at the regular scheduled time.

3 DOSAGE FORMS AND STRENGTHS

HUMIRA is a clear and colorless solution available as:

- Pen (HUMIRA Pen)
  Injection: 80 mg/0.8 mL in a single-dose pen.
  Injection: 40 mg/0.8 mL in a single-dose pen.
  Injection: 40 mg/0.4 mL in a single-dose pen.

- Prefilled Syringe
  Injection: 80 mg/0.8 mL in a single-dose prefilled glass syringe.
  Injection: 40 mg/0.8 mL in a single-dose prefilled glass syringe.
  Injection: 40 mg/0.4 mL in a single-dose prefilled glass syringe.
  Injection: 20 mg/0.2 mL in a single-dose prefilled glass syringe.
  Injection: 10 mg/0.1 mL in a single-dose prefilled glass syringe.

4 CONTRAINDICATIONS

None.

5 WARNINGS AND PRECAUTIONS

5.1 Serious Infections

Patients treated with HUMIRA are at increased risk for developing serious infections involving various organ systems and sites that may lead to hospitalization or death. Opportunistic infections due to bacterial, mycobacterial, invasive fungal, viral, parasitic, or other opportunistic pathogens including aspergillosis, blastomycosis, candidiasis, coccidioidomycosis, histoplasmosis, legionellosis, listeriosis, pneumocystosis and tuberculosis have been reported with TNF blockers. Patients have frequently presented with disseminated rather than localized disease.

The concomitant use of a TNF blocker and abatacept or anakinra was associated with a higher risk of serious infections in patients with rheumatoid arthritis (RA); therefore, the concomitant use of HUMIRA and these biologic products is not recommended in the treatment of patients with RA [see Warnings and Precautions (5.7, 5.11) and Drug Interactions (7.2)].

Treatment with HUMIRA should not be initiated in patients with an active infection, including localized infections. Patients 65 years of age and older, patients with co-morbid conditions and/or patients taking concomitant immunosuppressants (such as corticosteroids or methotrexate), may be at greater risk of infection. Consider the risks and benefits of treatment prior to initiating therapy in patients:

- with chronic or recurrent infection;
- who have been exposed to tuberculosis;
- with a history of an opportunistic infection;
- who have resided or traveled in areas of endemic tuberculosis or endemic mycoses, such as histoplasmosis, coccidioidomycosis, or blastomycosis; or
- with underlying conditions that may predispose them to infection.

Tuberculosis

Cases of reactivation of tuberculosis and new onset tuberculosis infections have been reported in patients receiving HUMIRA, including patients who have previously received treatment for latent or active tuberculosis. Reports included cases of pulmonary and extrapulmonary (i.e., disseminated) tuberculosis. Evaluate patients for tuberculosis risk factors and test for latent infection prior to initiating HUMIRA and periodically during therapy.

Treatment of latent tuberculosis infection prior to therapy with TNF blocking agents has been shown to reduce the risk of tuberculosis reactivation during therapy. Prior to initiating HUMIRA, assess if treatment for latent tuberculosis is needed; and consider an induration of ≥ 5 mm a positive tuberculin skin test result, even for patients previously vaccinated with Bacille Calmette-Guerin (BCG).

Consider anti-tuberculosis therapy prior to initiation of HUMIRA in patients with a past history of latent or active tuberculosis in whom an adequate course of treatment cannot be confirmed, and for patients with a negative test for latent tuberculosis but having risk factors for tuberculosis infection. Despite prophylactic treatment for tuberculosis, cases of reactivated tuberculosis have occurred in patients treated with HUMIRA. Consultation with a physician with expertise in the treatment of tuberculosis is recommended to aid in the decision whether initiating anti-tuberculosis therapy is appropriate for an individual patient.

Strongly consider tuberculosis in the differential diagnosis in patients who develop a new infection during HUMIRA treatment, especially in patients who have previously or recently traveled to countries with a high prevalence of tuberculosis, or who have had close contact with a person with active tuberculosis.

Monitoring

Closely monitor patients for the development of signs and symptoms of infection during and after treatment with HUMIRA, including the development of tuberculosis in patients who tested negative for latent tuberculosis infection prior to initiating therapy. Tests for latent tuberculosis infection may also be falsely negative while on therapy with HUMIRA.

Discontinue HUMIRA if a patient develops a serious infection or sepsis. For a patient who develops a new infection during treatment with HUMIRA, closely monitor them, perform a prompt and complete diagnostic workup appropriate for an immunocompromised patient, and initiate appropriate antimicrobial therapy.

Invasive Fungal Infections

If patients develop a serious systemic illness and they reside or travel in regions where mycoses are endemic, consider invasive fungal infection in the differential diagnosis. Antigen and antibody testing for histoplasmosis may be negative in some patients with active infection. Consider appropriate empiric antifungal therapy, taking into account both the risk for severe fungal infection and the risks of antifungal therapy, while a diagnostic workup is being performed. To aid in the management of such patients, consider consultation with a physician with expertise in the diagnosis and treatment of invasive fungal infections.

5.2 Malignancies

Consider the risks and benefits of TNF-blocker treatment including HUMIRA prior to initiating therapy in patients with a known malignancy other than a successfully treated non-melanoma skin cancer (NMSC) or when considering continuing a TNF blocker in patients who develop a malignancy.

Malignancies in Adults

In the controlled portions of clinical trials of some TNF-blockers, including HUMIRA, more cases of malignancies have been observed among TNF-blocker-treated adult subjects compared to control-treated adult subjects. During the controlled portions of 39 global HUMIRA clinical trials in adult subjects with rheumatoid arthritis (RA), psoriatic arthritis (PsA), ankylosing spondylitis (AS), Crohn’s disease (CD), ulcerative colitis (UC), plaque psoriasis (Ps), hidradenitis suppurativa (HS) and uveitis (UV), malignancies, other than non-melanoma (basal cell and squamous cell) skin cancer, were observed at a rate (95% confidence interval) of 0.7 (0.48, 1.03) per 100 patient-years among 7973 HUMIRA-treated subjects versus a rate of 0.7 (0.41, 1.17) per 100 patient-years among 4848 control-treated subjects (median duration of treatment of 4 months for HUMIRA-treated subjects and 4 months for control-treated subjects). In 52 global controlled and uncontrolled clinical trials of HUMIRA in adult subjects with RA, PsA, AS, CD, UC, Ps, HS and UV, the most frequently observed malignancies, other than lymphoma and NMSC, were breast, colon, prostate, lung, and melanoma. The malignancies in HUMIRA-treated subjects in the controlled and uncontrolled portions of the studies were similar in type and number to what would be expected in the general U.S. population according to the SEER database (adjusted for age, gender, and race).^1

In controlled trials of other TNF blockers in adult subjects at higher risk for malignancies (i.e., subjects with COPD with a significant smoking history and cyclophosphamide-treated subjects with Wegener’s granulomatosis), a greater portion of malignancies occurred in the TNF blocker group compared to the control group.

Non-Melanoma Skin Cancer

During the controlled portions of 39 global HUMIRA clinical trials in adult subjects with RA, PsA, AS, CD, UC, Ps, HS and UV, the rate (95% confidence interval) of NMSC was 0.8 (0.52, 1.09) per 100 patient-years among HUMIRA-treated subjects and 0.2 (0.10, 0.59) per 100 patient-years among control-treated subjects. Examine all patients, and in particular patients with a medical history of prior prolonged immunosuppressant therapy or psoriasis patients with a history of PUVA treatment for the presence of NMSC prior to and during treatment with HUMIRA.

Lymphoma and Leukemia

In the controlled portions of clinical trials of all the TNF-blockers in adults, more cases of lymphoma have been observed among TNF-blocker-treated subjects compared to control-treated subjects. In the controlled portions of 39 global HUMIRA clinical trials in adult subjects with RA, PsA, AS, CD, UC, Ps, HS and UV, 2 lymphomas occurred among 7973 HUMIRA-treated subjects versus 1 among 4848 control-treated subjects. In 52 global controlled and uncontrolled clinical trials of HUMIRA in adult subjects with RA, PsA, AS, CD, UC, Ps, HS and UV with a median duration of approximately 0.7 years, including 24,605 subjects and over 40,215 patient-years of HUMIRA, the observed rate of lymphomas was approximately 0.11 per 100 patient-years. This is approximately 3-fold higher than expected in the general U.S. population according to the SEER database (adjusted for age, gender, and race).^1 Rates of lymphoma in clinical trials of HUMIRA cannot be compared to rates of lymphoma in clinical trials of other TNF blockers and may not predict the rates observed in a broader patient population. Patients with RA and other chronic inflammatory diseases, particularly those with highly active disease and/or chronic exposure to immunosuppressant therapies, may be at a higher risk (up to several fold) than the general population for the development of lymphoma, even in the absence of TNF blockers. Post-marketing cases of acute and chronic leukemia have been reported in association with TNF-blocker use in RA and other indications. Even in the absence of TNF-blocker therapy, patients with RA may be at a higher risk (approximately 2-fold) than the general population for the development of leukemia.

Malignancies in Pediatric Patients and Young Adults

Malignancies, some fatal, have been reported among children, adolescents, and young adults who received treatment with TNF-blockers (initiation of therapy ≤ 18 years of age), of which HUMIRA is a member. Approximately half the cases were lymphomas, including Hodgkin's and non-Hodgkin's lymphoma. The other cases represented a variety of different malignancies and included rare malignancies usually associated with immunosuppression and malignancies that are not usually observed in children and adolescents. The malignancies occurred after a median of 30 months of therapy (range 1 to 84 months). Most of the patients were receiving concomitant immunosuppressants. These cases were reported post-marketing and are derived from a variety of sources including registries and spontaneous postmarketing reports.

Postmarketing cases of hepatosplenic T-cell lymphoma (HSTCL), a rare type of T-cell lymphoma, have been reported in patients treated with TNF blockers including HUMIRA. These cases have had a very aggressive disease course and have been fatal. The majority of reported TNF blocker cases have occurred in patients with Crohn's disease or ulcerative colitis and the majority were in adolescent and young adult males. Almost all of these patients had received treatment with the immunosuppressants azathioprine or 6-mercaptopurine (6–MP) concomitantly with a TNF blocker at or prior to diagnosis. It is uncertain whether the occurrence of HSTCL is related to use of a TNF blocker or a TNF blocker in combination with these other immunosuppressants. The potential risk with the combination of azathioprine or 6-mercaptopurine and HUMIRA should be carefully considered.

5.3 Hypersensitivity Reactions

Anaphylaxis and angioneurotic edema have been reported following HUMIRA administration. If an anaphylactic or other serious allergic reaction occurs, immediately discontinue administration of HUMIRA and institute appropriate therapy. In clinical trials of HUMIRA, hypersensitivity reactions (e.g., rash, anaphylactoid reaction, fixed drug reaction, non-specified drug reaction, urticaria) have been observed.

5.4 Hepatitis B Virus Reactivation

Use of TNF blockers, including HUMIRA, may increase the risk of reactivation of hepatitis B virus (HBV) in patients who are chronic carriers of this virus. In some instances, HBV reactivation occurring in conjunction with TNF blocker therapy has been fatal. The majority of these reports have occurred in patients concomitantly receiving other medications that suppress the immune system, which may also contribute to HBV reactivation. Evaluate patients at risk for HBV infection for prior evidence of HBV infection before initiating TNF blocker therapy. Exercise caution in prescribing TNF blockers for patients identified as carriers of HBV. Adequate data are not available on the safety or efficacy of treating patients who are carriers of HBV with anti-viral therapy in conjunction with TNF blocker therapy to prevent HBV reactivation. For patients who are carriers of HBV and require treatment with TNF blockers, closely monitor such patients for clinical and laboratory signs of active HBV infection throughout therapy and for several months following termination of therapy. In patients who develop HBV reactivation, stop HUMIRA and initiate effective anti-viral therapy with appropriate supportive treatment. The safety of resuming TNF blocker therapy after HBV reactivation is controlled is not known. Therefore, exercise caution when considering resumption of HUMIRA therapy in this situation and monitor patients closely.

5.5 Neurologic Reactions

Use of TNF blocking agents, including HUMIRA, has been associated with rare cases of new onset or exacerbation of clinical symptoms and/or radiographic evidence of central nervous system demyelinating disease, including multiple sclerosis (MS) and optic neuritis, and peripheral demyelinating disease, including Guillain-Barré syndrome. Exercise caution in considering the use of HUMIRA in patients with preexisting or recent-onset central or peripheral nervous system demyelinating disorders; discontinuation of HUMIRA should be considered if any of these disorders develop. There is a known association between intermediate uveitis and central demyelinating disorders.

5.6 Hematological Reactions

Rare reports of pancytopenia including aplastic anemia have been reported with TNF blocking agents. Adverse reactions of the hematologic system, including medically significant cytopenia (e.g., thrombocytopenia, leukopenia) have been infrequently reported with HUMIRA. The causal relationship of these reports to HUMIRA remains unclear. Advise all patients to seek immediate medical attention if they develop signs and symptoms suggestive of blood dyscrasias or infection (e.g., persistent fever, bruising, bleeding, pallor) while on HUMIRA. Consider discontinuation of HUMIRA therapy in patients with confirmed significant hematologic abnormalities.

5.7 Increased Risk of Infection when Used with Anakinra

Concurrent use of anakinra (an interleukin-1 antagonist) and another TNF-blocker, was associated with a greater proportion of serious infections and neutropenia and no added benefit compared with the TNF-blocker alone in patients with RA. Therefore, the combination of HUMIRA and anakinra is not recommended [see Drug Interactions (7.2)].

5.8 Heart Failure

Cases of worsening congestive heart failure (CHF) and new onset CHF have been reported with TNF blockers. Cases of worsening CHF have also been observed with HUMIRA. HUMIRA has not been formally studied in patients with CHF; however, in clinical trials of another TNF blocker, a higher rate of serious CHF-related adverse reactions was observed. Exercise caution when using HUMIRA in patients who have heart failure and monitor them carefully.

5.9 Autoimmunity

Treatment with HUMIRA may result in the formation of autoantibodies and, rarely, in the development of a lupus-like syndrome or autoimmune hepatitis [see Adverse Reactions (6.1, 6.3)]. If a patient develops symptoms and findings suggestive of a lupus-like syndrome or autoimmune hepatitis following treatment with HUMIRA, discontinue treatment and evaluate the patient.

5.10 Immunizations

In a placebo-controlled clinical trial of subjects with RA, no difference was detected in anti-pneumococcal antibody response between HUMIRA and placebo treatment groups when the pneumococcal polysaccharide vaccine and influenza vaccine were administered concurrently with HUMIRA. Similar proportions of subjects developed protective levels of anti-influenza antibodies between HUMIRA and placebo treatment groups; however, titers in aggregate to influenza antigens were moderately lower in subjects receiving HUMIRA. The clinical significance of this is unknown. Patients on HUMIRA may receive concurrent vaccinations, except for live vaccines. No data are available on the secondary transmission of infection by live vaccines in patients receiving HUMIRA.

It is recommended that pediatric patients, if possible, be brought up to date with all immunizations in agreement with current immunization guidelines prior to initiating HUMIRA therapy. Patients on HUMIRA may receive concurrent vaccinations, except for live vaccines.

The safety of administering live or live-attenuated vaccines in infants exposed to HUMIRA in utero is unknown. Risks and benefits should be considered prior to vaccinating (live or live-attenuated) exposed infants [see Use in Specific Populations (8.1, 8.4)].

5.11 Increased Risk of Infection When Used with Abatacept

In controlled trials, the concurrent administration of TNF-blockers and abatacept was associated with a greater proportion of serious infections than the use of a TNF-blocker alone; the combination therapy, compared to the use of a TNF-blocker alone, has not demonstrated improved clinical benefit in the treatment of RA. Therefore, the combination of abatacept with TNF-blockers including HUMIRA is not recommended [see Drug Interactions (7.2)].

6 ADVERSE REACTIONS

The following clinically significant adverse reactions are described elsewhere in the labeling:

- Serious Infections [see Warnings and Precautions (5.1)]
- Malignancies [see Warnings and Precautions (5.2)]
- Hypersensitivity Reactions [see Warnings and Precautions (5.3)]
- Hepatitis B Virus Reactivation [see Warnings and Precautions (5.4)]
- Neurologic Reactions [see Warnings and Precautions (5.5)]
- Hematological Reactions [see Warnings and Precautions (5.6)]
- Heart Failure [see Warnings and Precautions (5.8)]
- Autoimmunity [see Warnings and Precautions (5.9)]

6.1 Clinical Trials Experience

Because clinical trials are conducted under widely varying conditions, adverse reaction rates observed in the clinical trials of a drug cannot be directly compared to rates in the clinical trials of another drug and may not reflect the rates observed in practice.

The most common adverse reaction with HUMIRA was injection site reactions. In placebo-controlled trials, 20% of subjects treated with HUMIRA developed injection site reactions (erythema and/or itching, hemorrhage, pain or swelling), compared to 14% of subjects receiving placebo. Most injection site reactions were described as mild and generally did not necessitate drug discontinuation.

The proportion of subjects who discontinued treatment due to adverse reactions during the double-blind, placebo-controlled portion of studies in subjects with RA (i.e., Studies RA-I, RA-II, RA-III and RA-IV) was 7% for subjects taking HUMIRA and 4% for placebo-treated subjects. The most common adverse reactions leading to discontinuation of HUMIRA in these RA studies were clinical flare reaction (0.7%), rash (0.3%) and pneumonia (0.3%).

Infections

In the controlled portions of the 39 global HUMIRA clinical trials in adult subjects with RA, PsA, AS, CD, UC, Ps, HS and UV, the rate of serious infections was 4.3 per 100 patient-years in 7973 HUMIRA-treated subjects versus a rate of 2.9 per 100 patient-years in 4848 control-treated subjects. Serious infections observed included pneumonia, septic arthritis, prosthetic and post-surgical infections, erysipelas, cellulitis, diverticulitis, and pyelonephritis [see Warnings and Precautions (5.1)].

Tuberculosis and Opportunistic Infections

In 52 global controlled and uncontrolled clinical trials in RA, PsA, AS, CD, UC, Ps, HS and UV that included 24,605 HUMIRA-treated subjects, the rate of reported active tuberculosis was 0.20 per 100 patient-years and the rate of positive PPD conversion was 0.09 per 100 patient-years. In a subgroup of 10,113 U.S. and Canadian HUMIRA-treated subjects, the rate of reported active TB was 0.05 per 100 patient-years and the rate of positive PPD conversion was 0.07 per 100 patient-years. These trials included reports of miliary, lymphatic, peritoneal, and pulmonary TB. Most of the TB cases occurred within the first eight months after initiation of therapy and may reflect recrudescence of latent disease. In these global clinical trials, cases of serious opportunistic infections have been reported at an overall rate of 0.05 per 100 patient-years. Some cases of serious opportunistic infections and TB have been fatal [see Warnings and Precautions (5.1)].

Autoantibodies

In the rheumatoid arthritis controlled trials, 12% of subjects treated with HUMIRA and 7% of placebo-treated subjects that had negative baseline ANA titers developed positive titers at week 24. Two subjects out of 3046 treated with HUMIRA developed clinical signs suggestive of new-onset lupus-like syndrome. The subjects improved following discontinuation of therapy. No subjects developed lupus nephritis or central nervous system symptoms. The impact of long-term treatment with HUMIRA on the development of autoimmune diseases is unknown.

Liver Enzyme Elevations

There have been reports of severe hepatic reactions including acute liver failure in subjects receiving TNF-blockers. In controlled Phase 3 trials of HUMIRA (40 mg SC every other week) in subjects with RA, PsA, and AS with control period duration ranging from 4 to 104 weeks, ALT elevations ≥ 3 x ULN occurred in 3.5% of HUMIRA-treated subjects and 1.5% of control-treated subjects. Since many of these subjects in these trials were also taking medications that cause liver enzyme elevations (e.g., NSAIDS, MTX), the relationship between HUMIRA and the liver enzyme elevations is not clear. In a controlled Phase 3 trial of HUMIRA in subjects with polyarticular JIA who were 4 to 17 years, ALT elevations ≥ 3 x ULN occurred in 4.4% of HUMIRA-treated subjects and 1.5% of control-treated subjects (ALT more common than AST); liver enzyme test elevations were more frequent among those treated with the combination of HUMIRA and MTX than those treated with HUMIRA alone. In general, these elevations did not lead to discontinuation of HUMIRA treatment. No ALT elevations ≥ 3 x ULN occurred in the open-label study of HUMIRA in subjects with polyarticular JIA who were 2 to <4 years.

In controlled Phase 3 trials of HUMIRA (initial doses of 160 mg and 80 mg, or 80 mg and 40 mg on Days 1 and 15, respectively, followed by 40 mg every other week) in adult subjects with Crohn’s Disease with a control period duration ranging from 4 to 52 weeks, ALT elevations ≥ 3 x ULN occurred in 0.9% of HUMIRA-treated subjects and 0.9% of control-treated subjects. In the Phase 3 trial of HUMIRA in pediatric subjects with Crohn’s disease which evaluated efficacy and safety of two body weight based maintenance dose regimens following body weight based induction therapy up to 52 weeks of treatment, ALT elevations ≥ 3 x ULN occurred in 2.6% (5/192) of subjects, of whom 4 were receiving concomitant immunosuppressants at baseline; none of these subjects discontinued due to abnormalities in ALT tests. In controlled Phase 3 trials of HUMIRA (initial doses of 160 mg and 80 mg on Days 1 and 15 respectively, followed by 40 mg every other week) in adult subjects with UC with control period duration ranging from 1 to 52 weeks, ALT elevations ≥3 x ULN occurred in 1.5% of HUMIRA-treated subjects and 1.0% of control-treated subjects. In the controlled Phase 3 trial of HUMIRA in subjects with pediatric ulcerative colitis (N=93), which evaluated efficacy and safety of a maintenance dose of 0.6 mg/kg (maximum of 40 mg) every other week (N=31) and a maintenance dose of 0.6 mg/kg (maximum of 40 mg) every week (N=32), following body weight based induction doses of 2.4 mg/kg (maximum of 160 mg) at Week 0 and Week 1, and 1.2 mg/kg (maximum of 80 mg) at Week 2 (N=63), or an induction dose of 2.4 mg/kg (maximum of 160 mg) at Week 0, placebo at Week 1, and 1.2 mg/kg (maximum of 80 mg) at Week 2 (N=30), ALT elevations ≥ 3 X ULN occurred in 1.1% (1/93) of subjects. In controlled Phase 3 trials of HUMIRA (initial dose of 80 mg then 40 mg every other week) in subjects with Ps with control period duration ranging from 12 to 24 weeks, ALT elevations ≥ 3 x ULN occurred in 1.8% of HUMIRA-treated subjects and 1.8% of control-treated subjects. In controlled trials of HUMIRA (initial doses of 160 mg at Week 0 and 80 mg at Week 2, followed by 40 mg every week starting at Week 4), in subjects with HS with a control period duration ranging from 12 to 16 weeks, ALT elevations ≥ 3 x ULN occurred in 0.3% of HUMIRA-treated subjects and 0.6% of control-treated subjects. In controlled trials of HUMIRA (initial doses of 80 mg at Week 0 followed by 40 mg every other week starting at Week 1) in adult subjects with uveitis with an exposure of 165.4 PYs and 119.8 PYs in HUMIRA-treated and control-treated subjects, respectively, ALT elevations ≥ 3 x ULN occurred in 2.4% of HUMIRA-treated subjects and 2.4% of control-treated subjects.

Other Adverse Reactions

Rheumatoid Arthritis Clinical Studies

The data described below reflect exposure to HUMIRA in 2468 subjects, including 2073 exposed for 6 months, 1497 exposed for greater than one year and 1380 in adequate and well-controlled studies (Studies RA-I, RA-II, RA-III, and RA-IV). HUMIRA was studied primarily in placebo-controlled trials and in long-term follow up studies for up to 36 months duration. The population had a mean age of 54 years, 77% were female, 91% were Caucasian and had moderately to severely active rheumatoid arthritis. Most subjects received 40 mg HUMIRA every other week [see Clinical Studies (14.1)].

Table 1 summarizes reactions reported at a rate of at least 5% in subjects treated with HUMIRA 40 mg every other week compared to placebo and with an incidence higher than placebo. In Study RA-III, the types and frequencies of adverse reactions in the second year open-label extension were similar to those observed in the one-year double-blind portion.

Table 1. Adverse Reactions Reported by ≥5% of Subjects Treated with HUMIRA During Placebo-Controlled Period of Pooled RA Studies (Studies RA-I, RA-II, RA-III, and RA-IV)
 | HUMIRA 40 mg subcutaneous Every Other Week | Placebo
 | (N=705) | (N=690)
Adverse Reaction (Preferred Term)
Respiratory
Upper respiratory infection | 17% | 13%
Sinusitis | 11% | 9%
Flu syndrome | 7% | 6%
Gastrointestinal
Nausea | 9% | 8%
Abdominal pain | 7% | 4%
Laboratory Tests*
Laboratory test abnormal | 8% | 7%
Hypercholesterolemia | 6% | 4%
Hyperlipidemia | 7% | 5%
Hematuria | 5% | 4%
Alkaline phosphatase increased | 5% | 3%
Other
Headache | 12% | 8%
Rash | 12% | 6%
Accidental injury | 10% | 8%
Injection site reaction ** | 8% | 1%
Back pain | 6% | 4%
Urinary tract infection | 8% | 5%
Hypertension | 5% | 3%
* Laboratory test abnormalities were reported as adverse reactions in European trials
** Does not include injection site erythema, itching, hemorrhage, pain or swelling

Less Common Adverse Reactions in Rheumatoid Arthritis Clinical Studies

Other infrequent serious adverse reactions that do not appear in the Warnings and Precautions or Adverse Reaction sections that occurred at an incidence of less than 5% in HUMIRA-treated subjects in RA studies (RA-I, RA-II, RA-III, and RA-IV) were:

Body As A Whole: Pain in extremity, pelvic pain, surgery, thorax pain

Cardiovascular System: Arrhythmia, atrial fibrillation, chest pain, coronary artery disorder, heart arrest, hypertensive encephalopathy, myocardial infarct, palpitation, pericardial effusion, pericarditis, syncope, tachycardia

Digestive System: Cholecystitis, cholelithiasis, esophagitis, gastroenteritis, gastrointestinal hemorrhage, hepatic necrosis, vomiting

Endocrine System: Parathyroid disorder

Hemic And Lymphatic System: Agranulocytosis, polycythemia

Metabolic And Nutritional Disorders: Dehydration, healing abnormal, ketosis, paraproteinemia, peripheral edema

Musculo-Skeletal System: Arthritis, bone disorder, bone fracture (not spontaneous), bone necrosis, joint disorder, muscle cramps, myasthenia, pyogenic arthritis, synovitis, tendon disorder

Neoplasia: Adenoma

Nervous System: Confusion, paresthesia, subdural hematoma, tremor

Respiratory System: Asthma, bronchospasm, dyspnea, lung function decreased, pleural effusion

Special Senses: Cataract

Thrombosis: Thrombosis leg

Urogenital System: Cystitis, kidney calculus, menstrual disorder

Juvenile Idiopathic Arthritis Clinical Studies

In general, the adverse reactions in the HUMIRA-treated subjects in the polyarticular juvenile idiopathic arthritis (JIA) trials (Studies JIA-I and JIA-II) [see Clinical Studies (14.2)] were similar in frequency and type to those seen in adult subjects [see Warnings and Precautions (5), Adverse Reactions (6)]. Important findings and differences from adults are discussed in the following paragraphs.

In Study JIA-I, HUMIRA was studied in 171 subjects who were 4 to 17 years of age, with polyarticular JIA. Severe adverse reactions reported in the study included neutropenia, streptococcal pharyngitis, increased aminotransferases, herpes zoster, myositis, metrorrhagia, and appendicitis. Serious infections were observed in 4% of subjects within approximately 2 years of initiation of treatment with HUMIRA and included cases of herpes simplex, pneumonia, urinary tract infection, pharyngitis, and herpes zoster.

In Study JIA-I, 45% of subjects experienced an infection while receiving HUMIRA with or without concomitant MTX in the first 16 weeks of treatment. The types of infections reported in HUMIRA-treated subjects were generally similar to those commonly seen in polyarticular JIA subjects who are not treated with TNF blockers. Upon initiation of treatment, the most common adverse reactions occurring in this population treated with HUMIRA were injection site pain and injection site reaction (19% and 16%, respectively). A less commonly reported adverse event in subjects receiving HUMIRA was granuloma annulare which did not lead to discontinuation of HUMIRA treatment.

In the first 48 weeks of treatment in Study JIA-I, non-serious hypersensitivity reactions were seen in approximately 6% of subjects and included primarily localized allergic hypersensitivity reactions and allergic rash.

In Study JIA-I, 10% of subjects treated with HUMIRA who had negative baseline anti-dsDNA antibodies developed positive titers after 48 weeks of treatment. No subject developed clinical signs of autoimmunity during the clinical trial.

Approximately 15% of subjects treated with HUMIRA developed mild-to-moderate elevations of creatine phosphokinase (CPK) in Study JIA-I. Elevations exceeding 5 times the upper limit of normal were observed in several subjects. CPK concentrations decreased or returned to normal in all subjects. Most subjects were able to continue HUMIRA without interruption.

In Study JIA-II, HUMIRA was studied in 32 subjects who were 2 to <4 years of age or 4 years of age and older weighing <15 kg with polyarticular JIA. The safety profile for this population was similar to the safety profile seen in subjects 4 to 17 years of age with polyarticular JIA.

In Study JIA-II, 78% of subjects experienced an infection while receiving HUMIRA. These included nasopharyngitis, bronchitis, upper respiratory tract infection, otitis media, and were mostly mild to moderate in severity. Serious infections were observed in 9% of subjects receiving HUMIRA in the study and included dental caries, rotavirus gastroenteritis, and varicella.

In Study JIA-II, non-serious allergic reactions were observed in 6% of subjects and included intermittent urticaria and rash, which were all mild in severity.

Psoriatic Arthritis and Ankylosing Spondylitis Clinical Studies

HUMIRA has been studied in 395 subjects with psoriatic arthritis (PsA) in two placebo-controlled trials and in an open label study and in 393 subjects with ankylosing spondylitis (AS) in two placebo-controlled studies [see Clinical Studies (14.3, 14.4)]. The safety profile for subjects with PsA and AS treated with HUMIRA 40 mg every other week was similar to the safety profile seen in subjects with RA, HUMIRA Studies RA-I through IV.

Crohn’s Disease Clinical Studies

Adults: The safety profile of HUMIRA in 1478 adult subjects with Crohn’s disease from four placebo-controlled and two open-label extension studies [see Clinical Studies (14.5)] was similar to the safety profile seen in subjects with RA.

Pediatric Patients 6 Years to 17 Years: The safety profile of HUMIRA in 192 pediatric subjects from one double-blind study (Study PCD-I) and one open-label extension study [see Clinical Studies (14.6)] was similar to the safety profile seen in adult subjects with Crohn’s disease.

During the 4-week open label induction phase of Study PCD-I, the most common adverse reactions occurring in the pediatric population treated with HUMIRA were injection site pain and injection site reaction (6% and 5%, respectively).

A total of 67% of children experienced an infection while receiving HUMIRA in Study PCD-I. These included upper respiratory tract infection and nasopharyngitis.

A total of 5% of children experienced a serious infection while receiving HUMIRA in Study PCD-I. These included viral infection, device related sepsis (catheter), gastroenteritis, H1N1 influenza, and disseminated histoplasmosis.

In Study PCD-I, allergic reactions were observed in 5% of children which were all non-serious and were primarily localized reactions.

Ulcerative Colitis Clinical Studies

Adults: The safety profile of HUMIRA in 1010 adult subjects with ulcerative colitis (UC) from two placebo-controlled studies and one open-label extension study [see Clinical Studies (14.7)] was similar to the safety profile seen in subjects with RA.

Pediatric Patients 5 Years to 17 Years: The safety profile of HUMIRA in 93 pediatric subjects with ulcerative colitis from one double-blind study and one open-label extension study [see Clinical Studies (14.8)] was similar to the safety profile seen in adult subjects with ulcerative colitis.

Plaque Psoriasis Clinical Studies

HUMIRA has been studied in 1696 subjects with plaque psoriasis (Ps) in placebo-controlled and open-label extension studies [see Clinical Studies (14.9)]. The safety profile for subjects with Ps treated with HUMIRA was similar to the safety profile seen in subjects with RA with the following exceptions. In the placebo-controlled portions of the clinical trials in Ps subjects, HUMIRA-treated subjects had a higher incidence of arthralgia when compared to controls (3% vs. 1%).

Hidradenitis Suppurativa Clinical Studies

HUMIRA has been studied in 727 subjects with hidradenitis suppurativa (HS) in three placebo-controlled studies and one open-label extension study [see Clinical Studies (14.10)]. The safety profile for subjects with HS treated with HUMIRA weekly was consistent with the known safety profile of HUMIRA.

Flare of HS, defined as ≥25% increase from baseline in abscesses and inflammatory nodule counts and with a minimum of 2 additional lesions, was documented in 22 (22%) of the 100 subjects who were withdrawn from HUMIRA treatment following the primary efficacy timepoint in two studies.

Uveitis Clinical Studies

HUMIRA has been studied in 464 adult subjects with uveitis (UV) in placebo-controlled and open-label extension studies and in 90 pediatric subjects with uveitis (Study PUV-I) [see Clinical Studies (14.11, 14.12)]. The safety profile for subjects with UV treated with HUMIRA was similar to the safety profile seen in subjects with RA.

6.2 Immunogenicity

As with all therapeutic proteins, there is potential for immunogenicity. The detection of antibody formation is highly dependent on the sensitivity and specificity of the assay. Additionally, the observed incidence of antibody (including neutralizing antibody) positivity in an assay may be influenced by several factors including assay methodology, sample handling, timing of sample collection, concomitant medications, and underlying disease. For these reasons, comparison of the incidence of antibodies in the studies described below with the incidence of antibodies in other studies or to other adalimumab products may be misleading.

There are two assays that have been used to measure anti-adalimumab antibodies. With the ELISA, antibodies to adalimumab could be detected only when serum adalimumab concentrations were < 2 mcg/mL. The ECL assay can detect anti-adalimumab antibody titers independent of adalimumab concentrations in the serum samples. The incidence of anti-adalimumab antibody (AAA) development in patients treated with HUMIRA are presented in Table 2.

Table 2: Anti-Adalimumab Antibody Development Determined by ELISA and ECL Assay in Patients Treated with HUMIRA
Indications |  | Study Duration | Anti-Adalimumab Antibody Incidence by ELISA (n/N) |  | Anti-Adalimumab Antibody Incidence by ECL Assay (n/N)
 |  |  | In all patients who received adalimumab | In patients with serum adalimumab concentrations < 2 mcg/mL
Rheumatoid Arthritisa |  | 6 to 12 months | 5% (58/1062) | NR | NA
Juvenile Idiopathic Arthritis (JIA) | 4 to 17 years of ageb | 48 weeks | 16% (27/171) | NR | NA
 | 2 to 4 years of age or ≥ 4 years of age and weighing < 15 kg | 24 weeks | 7% (1/15)c | NR | NA
Psoriatic Arthritisd |  | 48 weekse | 13% (24/178) | NR | NA
Ankylosing Spondylitis |  | 24 weeks | 9% (16/185) | NR | NA
Adult Crohn’s Disease |  | 56 weeks | 3% (7/269) | 8% (7/86) | NA
Pediatric Crohn’s Disease |  | 52 weeks | 3% (6/182) | 10% (6/58) | NA
Adult Ulcerative Colitis |  | 52 weeks | 5% (19/360) | 21% (19/92) | NA
Pediatric Ulcerative Colitis |  | 52 weeks | 3% (3/100) | 13% (3/23) | 33% (33/100)i
Plaque Psoriasisf |  | Up to 52 weeksg | 8% (77/920) | 21% (77/372) | NA
Hidradenitis Suppurativa |  | 36 weeks | 7% (30/461) | 28% (58/207)h | 61% (272/445)j
Non-infectious Uveitis |  | 52 weeks | 5% (12/249) | 21% (12/57) | 40% (99/249)k

n: number of patients with anti-adalimumab antibody; NR: not reported; NA: Not applicable (not performed)

a In patients receiving concomitant methotrexate (MTX), the incidence of anti-adalimumab antibody was 1% compared to 12% with HUMIRA monotherapy

b In patients receiving concomitant MTX, the incidence of anti-adalimumab antibody was 6% compared to 26% with HUMIRA monotherapy

c This patient received concomitant MTX

d In patients receiving concomitant MTX, the incidence of antibody development was 7% compared to 1% in RA

e Subjects enrolled after completing 2 previous studies of 24 weeks or 12 weeks of treatments.

f In plaque psoriasis patients who were on HUMIRA monotherapy and subsequently withdrawn from the treatment, the rate of antibodies to adalimumab after retreatment was similar to the rate observed prior to withdrawal

g One 12-week Phase 2 study and one 52-week Phase 3 study

h Among subjects in the 2 Phase 3 studies who stopped HUMIRA treatment for up to 24 weeks and in whom adalimumab serum levels subsequently declined to <2 mcg/mL (approximately 22% of total subjects studied)

i No apparent association between antibody development and safety was observed. The association of antibody development and efficacy outcome was not assessed due to limited number of subjects in each treatment group stratified by anti-adalimumab antibody titer.

j No apparent association between antibody development and safety was observed

k No correlation of antibody development to safety or efficacy outcomes was observed

Rheumatoid Arthritis and Psoriatic Arthritis: Subjects in Studies RA-I, RA-II, and RA-III were tested at multiple time points for antibodies to adalimumab using the ELISA during the 6- to 12-month period. No apparent correlation of antibody development to adverse reactions was observed. With monotherapy, subjects receiving every other week dosing may develop antibodies more frequently than those receiving weekly dosing. In subjects receiving the recommended dosage of 40 mg every other week as monotherapy, the ACR 20 response was lower among antibody-positive subjects than among antibody-negative subjects. The long-term immunogenicity of HUMIRA is unknown.

6.3 Postmarketing Experience

The following adverse reactions have been identified during post-approval use of HUMIRA. Because these reactions are reported voluntarily from a population of uncertain size, it is not always possible to reliably estimate their frequency or establish a causal relationship to HUMIRA exposure.

Gastrointestinal disorders: Diverticulitis, large bowel perforations including perforations associated with diverticulitis and appendiceal perforations associated with appendicitis, pancreatitis

General disorders and administration site conditions: Pyrexia

Hepato-biliary disorders: Liver failure, hepatitis, autoimmune hepatitis

Immune system disorders: Sarcoidosis

Neoplasms benign, malignant and unspecified (including cysts and polyps): Merkel Cell Carcinoma (neuroendocrine carcinoma of the skin)

Nervous system disorders: Demyelinating disorders (e.g., optic neuritis, Guillain-Barré syndrome), cerebrovascular accident

Respiratory disorders: Interstitial lung disease, including pulmonary fibrosis, pulmonary embolism

Skin reactions: Stevens Johnson Syndrome, cutaneous vasculitis, erythema multiforme, new or worsening psoriasis (all sub-types including pustular and palmoplantar), alopecia, lichenoid skin reaction

Vascular disorders: Systemic vasculitis, deep vein thrombosis

7 DRUG INTERACTIONS

7.1 Methotrexate

HUMIRA has been studied in rheumatoid arthritis (RA) patients taking concomitant methotrexate (MTX). Although MTX reduced the apparent adalimumab clearance, the data do not suggest the need for dose adjustment of either HUMIRA or MTX [see Clinical Pharmacology (12.3)].

7.2 Biological Products

In clinical studies in patients with RA, an increased risk of serious infections has been observed with the combination of TNF blockers with anakinra or abatacept, with no added benefit; therefore, use of HUMIRA with abatacept or anakinra is not recommended in patients with RA [see Warnings and Precautions (5.7, 5.11)]. A higher rate of serious infections has also been observed in patients with RA treated with rituximab who received subsequent treatment with a TNF blocker. There is insufficient information regarding the concomitant use of HUMIRA and other biologic products for the treatment of RA, PsA, AS, CD, UC, Ps, HS and UV. Concomitant administration of HUMIRA with other biologic DMARDS (e.g., anakinra and abatacept) or other TNF blockers is not recommended based upon the possible increased risk for infections and other potential pharmacological interactions.

7.3 Live Vaccines

Avoid the use of live vaccines with HUMIRA [see Warnings and Precautions (5.10)].

7.4 Cytochrome P450 Substrates

The formation of CYP450 enzymes may be suppressed by increased concentrations of cytokines (e.g., TNFα, IL-6) during chronic inflammation. It is possible for a molecule that antagonizes cytokine activity, such as adalimumab, to influence the formation of CYP450 enzymes. Upon initiation or discontinuation of HUMIRA in patients being treated with CYP450 substrates with a narrow therapeutic index, monitoring of the effect (e.g., warfarin) or drug concentration (e.g., cyclosporine or theophylline) is recommended and the individual dose of the drug product may be adjusted as needed.

8 USE IN SPECIFIC POPULATIONS

8.1 Pregnancy

Risk Summary

Available studies with use of adalimumab during pregnancy do not reliably establish an association between adalimumab and major birth defects. Clinical data are available from the Organization of Teratology Information Specialists (OTIS)/MotherToBaby HUMIRA Pregnancy Registry in pregnant women with rheumatoid arthritis (RA) or Crohn’s disease (CD). Registry results showed a rate of 10% for major birth defects with first trimester use of adalimumab in pregnant women with RA or CD and a rate of 7.5% for major birth defects in the disease-matched comparison cohort. The lack of pattern of major birth defects is reassuring and differences between exposure groups may have impacted the occurrence of birth defects (see Data).

Adalimumab is actively transferred across the placenta during the third trimester of pregnancy and may affect immune response in the in-utero exposed infant (see Clinical Considerations). In an embryo-fetal perinatal development study conducted in cynomolgus monkeys, no fetal harm or malformations were observed with intravenous administration of adalimumab during organogenesis and later in gestation, at doses that produced exposures up to approximately 373 times the maximum recommended human dose (MRHD) of 40 mg subcutaneous without methotrexate (see Data).

The estimated background risk of major birth defects and miscarriage for the indicated populations is unknown. All pregnancies have a background risk of birth defect, loss, or other adverse outcomes. In the U.S. general population, the estimated background risk of major birth defects and miscarriage in clinically recognized pregnancies is 2-4% and 15-20%, respectively.

Clinical Considerations

Disease-associated maternal and embryo/fetal risk

Published data suggest that the risk of adverse pregnancy outcomes in women with RA or inflammatory bowel disease (IBD) is associated with increased disease activity. Adverse pregnancy outcomes include preterm delivery (before 37 weeks of gestation), low birth weight (less than 2500 g) infants, and small for gestational age at birth.

Fetal/Neonatal Adverse Reactions

Monoclonal antibodies are increasingly transported across the placenta as pregnancy progresses, with the largest amount transferred during the third trimester (see Data). Risks and benefits should be considered prior to administering live or live-attenuated vaccines to infants exposed to HUMIRA in utero [see Use in Specific Populations (8.4)].

Data

Human Data

A prospective cohort pregnancy exposure registry conducted by OTIS/MotherToBaby in the U.S. and Canada between 2004 and 2016 compared the risk of major birth defects in live-born infants of 221 women (69 RA, 152 CD) treated with adalimumab during the first trimester and 106 women (74 RA, 32 CD) not treated with adalimumab.

The proportion of major birth defects among live-born infants in the adalimumab-treated and untreated cohorts was 10% (8.7% RA, 10.5% CD) and 7.5% (6.8% RA, 9.4% CD), respectively. The lack of pattern of major birth defects is reassuring and differences between exposure groups may have impacted the occurrence of birth defects. This study cannot reliably establish whether there is an association between adalimumab and major birth defects because of methodological limitations of the registry, including small sample size, the voluntary nature of the study, and the non-randomized design.

In an independent clinical study conducted in ten pregnant women with IBD treated with HUMIRA, adalimumab concentrations were measured in maternal serum as well as in cord blood (n=10) and infant serum (n=8) on the day of birth. The last dose of HUMIRA was given between 1 and 56 days prior to delivery. Adalimumab concentrations were 0.16-19.7 µg/mL in cord blood, 4.28-17.7 µg/mL in infant serum, and 0-16.1 µg/mL in maternal serum. In all but one case, the cord blood concentration of adalimumab was higher than the maternal serum concentration, suggesting adalimumab actively crosses the placenta. In addition, one infant had serum concentrations at each of the following: 6 weeks (1.94 µg/mL), 7 weeks (1.31 µg/mL), 8 weeks (0.93 µg/mL), and 11 weeks (0.53 µg/mL), suggesting adalimumab can be detected in the serum of infants exposed in utero for at least 3 months from birth.

Animal Data

In an embryo-fetal perinatal development study, pregnant cynomolgus monkeys received adalimumab from gestation days 20 to 97 at doses that produced exposures up to 373 times that achieved with the MRHD without methotrexate (on an AUC basis with maternal IV doses up to 100 mg/kg/week). Adalimumab did not elicit harm to the fetuses or malformations.

8.2 Lactation

Risk Summary

Limited data from case reports in the published literature describe the presence of adalimumab in human milk at infant doses of 0.1% to 1% of the maternal serum concentration. Published data suggest that the systemic exposure to a breastfed infant is expected to be low because adalimumab is a large molecule and is degraded in the gastrointestinal tract. However, the effects of local exposure in the gastrointestinal tract are unknown. There are no reports of adverse effects of adalimumab on the breastfed infant and no effects on milk production. The developmental and health benefits of breastfeeding should be considered along with the mother’s clinical need for HUMIRA and any potential adverse effects on the breastfed child from HUMIRA or from the underlying maternal condition.

8.4 Pediatric Use

The safety and effectiveness of HUMIRA have not been established in pediatric patients with psoriatic arthritis, ankylosing spondylitis, or plaque psoriasis.

The safety and effectiveness of HUMIRA have been established for:

- reducing signs and symptoms of moderately to severely active polyarticular JIA in pediatric patients 2 years of age and older.
- the treatment of moderately to severely active Crohn’s disease in pediatric patients 6 years of age and older.
- the treatment of moderately to severely active ulcerative colitis in pediatric patients 5 years of age and older.
- the treatment of moderate to severe hidradenitis suppurativa in patients 12 years of age and older.
- the treatment of non-infectious intermediate, posterior, and panuveitis in pediatric patients 2 years of age and older.

Due to its inhibition of TNFα, HUMIRA administered during pregnancy could affect immune response in the in utero-exposed newborn and infant. Data from eight infants exposed to HUMIRA in utero suggest adalimumab crosses the placenta [see Use in Specific Populations (8.1)]. The clinical significance of elevated adalimumab concentrations in infants is unknown. The safety of administering live or live-attenuated vaccines in exposed infants is unknown. Risks and benefits should be considered prior to vaccinating (live or live-attenuated) exposed infants.

Post-marketing cases of lymphoma, including hepatosplenic T-cell lymphoma and other malignancies, some fatal, have been reported among children, adolescents, and young adults who received treatment with TNF-blockers including HUMIRA [see Warnings and Precautions (5.2)].

Juvenile Idiopathic Arthritis

The safety and effectiveness of HUMIRA for the treatment of moderately to severely active polyarticular JIA have been established in pediatric patients 2 years of age and older. Use for this indication is supported by evidence from an adequate and well-controlled study (Study JIA-I) in patients 4 to 17 years of age [see Clinical Studies (14.2)] and a safety study (Study JIA-II) in patients 2 to <4 years of age where the safety profile was similar to patients 4 to 17 years of age [see Adverse Reactions (6.1)]. HUMIRA has not been studied in patients with polyarticular JIA less than 2 years of age or in patients with a weight below 10 kg.

The safety of HUMIRA in pediatric patients in the polyarticular JIA trials was generally similar to that observed in adults with certain exceptions [see Adverse Reactions (6.1)].

The safety and effectiveness of HUMIRA have not been established in pediatric patients with JIA less than 2 years of age.

Pediatric Crohn’s Disease

The safety and effectiveness of HUMIRA for the treatment of moderately to severely active Crohn’s disease have been established in pediatric patients 6 years of age and older. Use of HUMIRA for this indication is supported by evidence from adequate and well-controlled studies in adults with additional data from a randomized, double-blind, 52-week clinical study of two dose concentrations of HUMIRA in 192 pediatric patients (6 years to 17 years of age) [see Adverse Reactions (6.1), Clinical Pharmacology (12.2, 12.3), Clinical Studies (14.6)]. The adverse reaction profile in patients 6 years to 17 years of age was similar to adults.

The safety and effectiveness of HUMIRA have not been established in pediatric patients with Crohn’s disease less than 6 years of age.

Pediatric Ulcerative Colitis

The safety and effectiveness of HUMIRA for the treatment of moderately to severely active ulcerative colitis have been established in pediatric patients 5 years of age and older. Use of HUMIRA for this indication is supported by evidence from adequate and well-controlled studies in adults with additional data from a randomized, double-blind, 52-week clinical study of two dose concentrations of HUMIRA in 93 pediatric patients (5 years to 17 years of age) [see Adverse Reactions (6.1), Clinical Pharmacology (12.3), Clinical Studies (14.8)]. The adverse reaction profile in patients 5 years to 17 years of age was similar to adults.

The effectiveness of HUMIRA has not been established in patients who have lost response or were intolerant to TNF blockers.

The safety and effectiveness of HUMIRA have not been established in pediatric patients with ulcerative colitis less than 5 years of age.

Pediatric Uveitis

The safety and effectiveness of HUMIRA for the treatment of non-infectious, intermediate, posterior, and panuveitis have been established in pediatric patients 2 years of age and older. Use of HUMIRA for this indication is supported by evidence from adequate and well-controlled studies of HUMIRA in adults and a 2:1 randomized, controlled clinical study in 90 pediatric patients [see Clinical Studies (14.12)]. The safety and effectiveness of HUMIRA have not been established in pediatric patients with uveitis less than 2 years of age.

Hidradenitis Suppurativa

Use of HUMIRA in pediatric patients 12 years of age and older for the treatment of moderate to severe HS is supported by evidence from adequate and well-controlled studies of HUMIRA in adult HS patients. Additional population pharmacokinetic modeling and simulation predicted that weight-based dosing of HUMIRA in pediatric patients 12 years of age and older can provide generally similar exposure to adult HS patients. The course of HS is sufficiently similar in adult and adolescent patients to allow extrapolation of data from adult to adolescent patients. The recommended dosage in pediatric patients 12 years of age or older is based on body weight [see Dosage and Administration (2.6), Clinical Pharmacology (12.3), and Clinical Studies (14.10)].

The safety and effectiveness of HUMIRA have not been established in patients less than 12 years of age with HS.

8.5 Geriatric Use

In clinical studies of RA (Studies RA-I, RA-II, RA-III, and RA-IV), a total of 519 subjects 65 years of age and older, including 107 subjects 75 years of age and older, received HUMIRA. No overall difference in effectiveness was observed between these subjects and younger adult subjects.

The frequency of serious infection and malignancy among HUMIRA treated subjects 65 years of age and older was higher than for those less than 65 years of age. Consider the benefits and risks of HUMIRA in patients 65 years of age and older. In patients treated with HUMIRA, closely monitor for the development of infection or malignancy [see Warnings and Precautions (5.1, 5.2)].

10 OVERDOSAGE

Doses up to 10 mg/kg have been administered to patients in clinical trials without evidence of dose-limiting toxicities. In case of overdosage, it is recommended that the patient be monitored for any signs or symptoms of adverse reactions or effects and appropriate symptomatic treatment instituted immediately.

Consider contacting the Poison Help line (1-800-222-1222) or medical toxicologist for additional overdose management recommendations.

11 DESCRIPTION

Adalimumab is a tumor necrosis factor blocker. Adalimumab is a recombinant human IgG1 monoclonal antibody created using phage display technology resulting in an antibody with human derived heavy and light chain variable regions and human IgG1:k constant regions. Adalimumab is produced by recombinant DNA technology in a mammalian cell (Chinese Hamster Ovary (CHO)) expression system and is purified by a process that includes specific viral inactivation and removal steps. It consists of 1330 amino acids and has a molecular weight of approximately 148 kilodaltons.

HUMIRA (adalimumab) injection is supplied as a sterile, preservative-free solution for subcutaneous administration. The drug product is supplied as either a single-dose, prefilled pen (HUMIRA Pen) or as a single-dose, 1 mL prefilled glass syringe. Enclosed within the pen is a single-dose, 1 mL prefilled glass syringe. The solution of HUMIRA is clear and colorless, with a pH of about 5.2.

Each 80 mg/0.8 mL prefilled syringe or prefilled pen delivers 0.8 mL (80 mg) of drug product. Each 0.8 mL of HUMIRA contains adalimumab (80 mg), mannitol (33.6 mg), polysorbate 80 (0.8 mg), and Water for Injection, USP.

Each 40 mg/0.4 mL prefilled syringe or prefilled pen delivers 0.4 mL (40 mg) of drug product. Each 0.4 mL of HUMIRA contains adalimumab (40 mg), mannitol (16.8 mg), polysorbate 80 (0.4 mg), and Water for Injection, USP.

Each 40 mg/0.8 mL prefilled syringe or prefilled pen delivers 0.8 mL (40 mg) of drug product. Each 0.8 mL of HUMIRA contains adalimumab (40 mg), citric acid monohydrate (1.04 mg), dibasic sodium phosphate dihydrate (1.22 mg), mannitol (9.6 mg), monobasic sodium phosphate dihydrate (0.69 mg), polysorbate 80 (0.8 mg), sodium chloride (4.93 mg), sodium citrate (0.24 mg) and Water for Injection, USP. Sodium hydroxide is added as necessary to adjust pH.

Each 20 mg/0.2 mL prefilled syringe delivers 0.2 mL (20 mg) of drug product. Each 0.2 mL of HUMIRA contains adalimumab (20 mg), mannitol (8.4 mg), polysorbate 80 (0.2 mg), and Water for Injection, USP.

Each 10 mg/0.1 mL prefilled syringe delivers 0.1 mL (10 mg) of drug product. Each 0.1 mL of HUMIRA contains adalimumab (10 mg), mannitol (4.2 mg), polysorbate 80 (0.1 mg), and Water for Injection, USP.

12 CLINICAL PHARMACOLOGY

12.1 Mechanism of Action

Adalimumab binds specifically to TNF-alpha and blocks its interaction with the p55 and p75 cell surface TNF receptors. Adalimumab also lyses surface TNF expressing cells in vitro in the presence of complement. Adalimumab does not bind or inactivate lymphotoxin (TNF-beta). TNF is a naturally occurring cytokine that is involved in normal inflammatory and immune responses. Elevated concentrations of TNF are found in the synovial fluid of patients with RA, JIA, PsA, and AS and play an important role in both the pathologic inflammation and the joint destruction that are hallmarks of these diseases. Increased concentrations of TNF are also found in psoriasis plaques. In Ps, treatment with HUMIRA may reduce the epidermal thickness and infiltration of inflammatory cells. The relationship between these pharmacodynamic activities and the mechanism(s) by which HUMIRA exerts its clinical effects is unknown.

Adalimumab also modulates biological responses that are induced or regulated by TNF, including changes in the concentrations of adhesion molecules responsible for leukocyte migration (ELAM-1, VCAM-1, and ICAM-1 with an IC50 of 1-2 X 10^-10M).

12.2 Pharmacodynamics

After treatment with HUMIRA, a decrease in concentrations of acute phase reactants of inflammation (C-reactive protein [CRP] and erythrocyte sedimentation rate [ESR]) and serum cytokines (IL-6) was observed compared to baseline in patients with rheumatoid arthritis. A decrease in CRP concentrations was also observed in patients with Crohn’s disease, ulcerative colitis and hidradenitis suppurativa. Serum concentrations of matrix metalloproteinases (MMP-1 and MMP-3) that produce tissue remodeling responsible for cartilage destruction were also decreased after HUMIRA administration.

For pediatric patients 5 years to 17 years with ulcerative colitis, the recommended dosage of HUMIRA is based on modeled dose/exposure-efficacy relationships and pharmacokinetic data. There are no anticipated clinically relevant differences in efficacy between the studied higher dosage administered in the clinical trial (Weeks 0 to 52 in Study PUC-I) [see Clinical Studies (14.8)] and the recommended dosage [see Dosage and Administration (2.4)].

12.3 Pharmacokinetics

The pharmacokinetics of adalimumab were linear over the dose range of 0.5 to 10 mg/kg following administration of a single intravenous dose (HUMIRA is not approved for intravenous use). Following 20, 40, and 80 mg every other week and every week subcutaneous administration, adalimumab mean serum trough concentrations at steady state increased approximately proportionally with dose in RA patients. The mean terminal half-life was approximately 2 weeks, ranging from 10 to 20 days across studies. Healthy subjects and patients with RA displayed similar adalimumab pharmacokinetics.

Adalimumab exposure in patients treated with 80 mg every other week is estimated to be comparable with that in patients treated with 40 mg every week.

Absorption

The average absolute bioavailability of adalimumab following a single 40 mg subcutaneous dose was 64%. The mean time to reach the maximum concentration was 5.5 days (131 ± 56 hours) and the maximum serum concentration was 4.7 ± 1.6 mcg/mL in healthy subjects following a single 40 mg subcutaneous administration of HUMIRA.

Distribution

The distribution volume (Vss) ranged from 4.7 to 6.0 L following intravenous administration of doses ranging from 0.25 to 10 mg/kg in RA patients.

Elimination

The single dose pharmacokinetics of adalimumab in RA patients were determined in several studies with intravenous doses ranging from 0.25 to 10 mg/kg. The systemic clearance of adalimumab is approximately 12 mL/hr. In long-term studies with dosing more than two years, there was no evidence of changes in clearance over time in RA patients.

Patient Population

Rheumatoid Arthritis and Ankylosing Spondylitis: In patients receiving 40 mg HUMIRA every other week, adalimumab mean steady-state trough concentrations were approximately 5 mcg/mL and 8 to 9 mcg/mL, without and with MTX concomitant treatment, respectively. Adalimumab concentrations in the synovial fluid from five rheumatoid arthritis patients ranged from 31 to 96% of those in serum. The pharmacokinetics of adalimumab in patients with AS were similar to those in patients with RA.

Psoriatic Arthritis: In patients receiving 40 mg every other week, adalimumab mean steady-state trough concentrations were 6 to 10 mcg/mL and 8.5 to 12 mcg/mL, without and with MTX concomitant treatment, respectively.

Plaque Psoriasis: Adalimumab mean steady-state trough concentration was approximately 5 to 6 mcg/mL during HUMIRA 40 mg every other week treatment.

Adult Uveitis: Adalimumab mean steady concentration was approximately 8 to 10 mcg/mL during HUMIRA 40 mg every other week treatment.

Adult Hidradenitis Suppurativa: Adalimumab trough concentrations were approximately 7 to 8 mcg/mL at Week 2 and Week 4, respectively, after receiving 160 mg on Week 0 followed by 80 mg on Week 2. Mean steady-state trough concentrations at Week 12 through Week 36 were approximately 7 to 11 mcg/mL during HUMIRA 40 mg every week treatment.

Adult Crohn’s Disease: Adalimumab mean trough concentrations were approximately 12 mcg/mL at Week 2 and Week 4 after receiving 160 mg on Week 0 followed by 80 mg on Week 2. Mean steady-state trough concentrations were 7 mcg/mL at Week 24 and Week 56 during HUMIRA 40 mg every other week treatment.

Adult Ulcerative Colitis: Adalimumab mean trough concentrations were approximately 12 mcg/mL at Week 2 and Week 4 after receiving 160 mg on Week 0 followed by 80 mg on Week 2. Mean steady-state trough concentrations were approximately 8 mcg/mL and 15 mcg/mL at Week 52 after receiving a dose of HUMIRA 40 mg every other week and 40 mg every week, respectively.

Anti-Drug Antibody Effects on Pharmacokinetics

Rheumatoid Arthritis: A trend toward higher apparent clearance of adalimumab in the presence of anti-adalimumab antibodies was identified.

Pediatric Ulcerative Colitis: Antibodies to adalimumab by ECL assay were associated with reduced serum adalimumab concentrations in pediatric patients with moderately to severely active ulcerative colitis.

Hidradenitis Suppurativa: In subjects with moderate to severe HS, antibodies to adalimumab were associated with reduced serum adalimumab concentrations. In general, the extent of reduction in serum adalimumab concentrations is greater with increasing titers of antibodies to adalimumab.

Specific Populations

Geriatric Patients: A lower clearance with increasing age was observed in patients with RA aged 40 to >75 years.

Pediatric Patients:

Juvenile Idiopathic Arthritis:

- 4 years to 17 years of age: The adalimumab mean steady-state trough concentrations were 6.8 mcg/mL and 10.9 mcg/mL in patients weighing <30 kg receiving 20 mg HUMIRA subcutaneously every other week as monotherapy or with concomitant MTX, respectively. The adalimumab mean steady-state trough concentrations were 6.6 mcg/mL and 8.1 mcg/mL in patients weighing ≥30 kg receiving 40 mg HUMIRA subcutaneously every other week as monotherapy or with MTX concomitant treatment, respectively.
- 2 years to <4 years of age or 4 years of age and older weighing <15 kg: The adalimumab mean steady-state trough adalimumab concentrations were 6.0 mcg/mL and 7.9 mcg/mL in patients receiving HUMIRA subcutaneously every other week as monotherapy or with MTX concomitant treatment, respectively.

Pediatric Hidradenitis Suppurativa: Adalimumab concentrations in adolescent patients with HS receiving the recommended dosage regimens are predicted to be similar to those observed in adult subjects with HS based on population pharmacokinetic modeling and simulation.

Pediatric Crohn's Disease: Adalimumab mean ± SD concentrations were 15.7±6.5 mcg/mL at Week 4 following 160 mg at Week 0 and 80 mg at Week 2, and 10.5±6.0 mcg/mL at Week 52 following 40 mg every other week dosing in patients weighing ≥ 40 kg. Adalimumab mean ± SD concentrations were 10.6±6.1 mcg/mL at Week 4 following dosing 80 mg at Week 0 and 40 mg at Week 2, and 6.9±3.6 mcg/mL at Week 52 following 20 mg every other week dosing in patients weighing < 40 kg.

Pediatric Ulcerative Colitis: The adalimumab mean steady-state trough concentration was 5.0±3.3 mcg/mL at Week 52 following subcutaneous administration of 0.6 mg/kg (maximum of 40 mg) every other week in pediatric UC patients 5 years to 17 years of age. In patients who received 0.6 mg/kg (maximum of 40 mg) every week, the mean steady-state trough concentration was 15.7±5.6 mcg/mL at Week 52 in pediatric UC patients 5 years to 17 years of age.

Male and Female Patients: No gender-related pharmacokinetic differences were observed after correction for a patient’s body weight. Healthy subjects and patients with rheumatoid arthritis displayed similar adalimumab pharmacokinetics.

Patients with Renal or Hepatic Impairment: No pharmacokinetic data are available in patients with hepatic or renal impairment.

Rheumatoid factor or CRP concentrations: Minor increases in apparent clearance were predicted in RA patients receiving doses lower than the recommended dose and in RA patients with high rheumatoid factor or CRP concentrations. These increases are not likely to be clinically important.

Drug Interaction Studies:

Methotrexate: MTX reduced adalimumab apparent clearance after single and multiple dosing by 29% and 44% respectively, in patients with RA [see Drug Interactions (7.1)].

13 NONCLINICAL TOXICOLOGY

13.1 Carcinogenesis, Mutagenesis, Impairment of Fertility

Long-term animal studies of HUMIRA have not been conducted to evaluate the carcinogenic potential or its effect on fertility.

14 CLINICAL STUDIES

14.1 Clinical Studies in Rheumatoid Arthritis

The efficacy and safety of HUMIRA were assessed in five randomized, double-blind studies in subjects ≥18 years of age with active rheumatoid arthritis (RA) diagnosed according to American College of Rheumatology (ACR) criteria. Subjects had at least 6 swollen and 9 tender joints. HUMIRA was administered subcutaneously in combination with methotrexate (MTX) (12.5 to 25 mg, Studies RA-I, RA-III and RA-V) or as monotherapy (Studies RA-II and RA-V) or with other disease-modifying anti-rheumatic drugs (DMARDs) (Study RA-IV).

Study RA-I evaluated 271 subjects who had failed therapy with at least one but no more than four DMARDs and had inadequate response to MTX. Doses of 20, 40 or 80 mg of HUMIRA or placebo were given every other week for 24 weeks.

Study RA-II evaluated 544 subjects who had failed therapy with at least one DMARD. Doses of placebo, 20 or 40 mg of HUMIRA were given as monotherapy every other week or weekly for 26 weeks.

Study RA-III evaluated 619 subjects who had an inadequate response to MTX. Subjects received placebo, 40 mg of HUMIRA every other week with placebo injections on alternate weeks, or 20 mg of HUMIRA weekly for up to 52 weeks. Study RA-III had an additional primary endpoint at 52 weeks of inhibition of disease progression (as detected by X-ray results). Upon completion of the first 52 weeks, 457 subjects enrolled in an open-label extension phase in which 40 mg of HUMIRA was administered every other week for up to 5 years.

Study RA-IV assessed safety in 636 subjects who were either DMARD-naive or were permitted to remain on their pre-existing rheumatologic therapy provided that therapy was stable for a minimum of 28 days. Subjects were randomized to 40 mg of HUMIRA or placebo every other week for 24 weeks.

Study RA-V evaluated 799 subjects with moderately to severely active RA of less than 3 years duration who were ≥18 years old and MTX naïve. Subjects were randomized to receive either MTX (optimized to 20 mg/week by week 8), HUMIRA 40 mg every other week or HUMIRA/MTX combination therapy for 104 weeks. Subjects were evaluated for signs and symptoms, and for radiographic progression of joint damage. The median disease duration among subjects enrolled in the study was 5 months. The median MTX dose achieved was 20 mg.

Clinical Response

The percent of HUMIRA treated subjects achieving ACR 20, 50 and 70 responses in Studies RA-II and III are shown in Table 3.

Table 3. ACR Responses in Studies RA-II and RA-III (Percent of Subjects)
 | Study RA-II Monotherapy (26 weeks) |  |  | Study RA-III Methotrexate Combination (24 and 52 weeks)
Response | Placebo | HUMIRA | HUMIRA | Placebo/MTX | HUMIRA/MTX
 |  | 40 mg every | 40 mg weekly |  | 40 mg every
 |  | other week |  |  | other week
 | N=110 | N=113 | N=103 | N=200 | N=207
ACR20
Month 6 | 19% | 46%* | 53%* | 30% | 63%*
Month 12 | NA | NA | NA | 24% | 59%*
ACR50
Month 6 | 8% | 22%* | 35%* | 10% | 39%*
Month 12 | NA | NA | NA | 10% | 42%*
ACR70
Month 6 | 2% | 12%* | 18%* | 3% | 21%*
Month 12 | NA | NA | NA | 5% | 23%*
* p<0.01, HUMIRA vs. placebo

The results of Study RA-I were similar to Study RA-III; subjects receiving HUMIRA 40 mg every other week in Study RA-I also achieved ACR 20, 50 and 70 response rates of 65%, 52% and 24%, respectively, compared to placebo responses of 13%, 7% and 3% respectively, at 6 months (p<0.01).

The results of the components of the ACR response criteria for Studies RA-II and RA-III are shown in Table 4. ACR response rates and improvement in all components of ACR response were maintained to week 104. Over the 2 years in Study RA-III, 20% of HUMIRA subjects receiving 40 mg every other week achieved a major clinical response, defined as maintenance of an ACR 70 response over a 6-month period. ACR responses were maintained in similar proportions of subjects for up to 5 years with continuous HUMIRA treatment in the open-label portion of Study RA-III.

Table 4. Components of ACR Response in Studies RA-II and RA-III
 | Study RA-II |  |  |  | Study RA-III
Parameter (median) | Placebo N=110 |  | HUMIRAa N=113 |  | Placebo/MTX N=200 |  | HUMIRAa/MTX N=207
 | Baseline | Wk 26 | Baseline | Wk 26 | Baseline | Wk 24 | Baseline | Wk 24
Number of tender joints (0-68) | 35 | 26 | 31 | 16* | 26 | 15 | 24 | 8*
Number of swollen joints (0-66) | 19 | 16 | 18 | 10* | 17 | 11 | 18 | 5*
Physician global assessmentb | 7.0 | 6.1 | 6.6 | 3.7* | 6.3 | 3.5 | 6.5 | 2.0*
Patient global assessmentb | 7.5 | 6.3 | 7.5 | 4.5* | 5.4 | 3.9 | 5.2 | 2.0*
Painb | 7.3 | 6.1 | 7.3 | 4.1* | 6.0 | 3.8 | 5.8 | 2.1*
Disability index (HAQ)c | 2.0 | 1.9 | 1.9 | 1.5* | 1.5 | 1.3 | 1.5 | 0.8*
CRP (mg/dL) | 3.9 | 4.3 | 4.6 | 1.8* | 1.0 | 0.9 | 1.0 | 0.4*
a 40 mg HUMIRA administered every other week
b Visual analogue scale; 0 = best, 10 = worst
c Disability Index of the Health Assessment Questionnaire; 0 = best, 3 = worst, measures the patient’s ability to perform the following: dress/groom, arise, eat, walk, reach, grip, maintain hygiene, and maintain daily activity
* p<0.001, HUMIRA vs. placebo, based on mean change from baseline

The time course of ACR 20 response for Study RA-III is shown in Figure 1.

In Study RA-III, 85% of subjects with ACR 20 responses at week 24 maintained the response at 52 weeks. The time course of ACR 20 response for Study RA-I and Study RA-II were similar.

Figure 1. Study RA-III ACR 20 Responses over 52 Weeks

In Study RA-IV, 53% of subjects treated with HUMIRA 40 mg every other week plus standard of care had an ACR 20 response at week 24 compared to 35% on placebo plus standard of care (p<0.001). No unique adverse reactions related to the combination of HUMIRA (adalimumab) and other DMARDs were observed.

In Study RA-V with MTX naïve subjects with recent onset RA, the combination treatment with HUMIRA plus MTX led to greater percentages of subjects achieving ACR responses than either MTX monotherapy or HUMIRA monotherapy at Week 52 and responses were sustained at Week 104 (see Table 5).

Table 5. ACR Response in Study RA-V (Percent of Subjects)
Response | MTXb N=257 | HUMIRAc N=274 | HUMIRA/MTX N=268
ACR20 Week 52 Week 104 | 63% 56% | 54% 49% | 73% 69%
ACR50 Week 52 Week 104 | 46% 43% | 41% 37% | 62% 59%
ACR70 Week 52 Week 104 | 27% 28% | 26% 28% | 46% 47%
Major Clinical Response a | 28% | 25% | 49%
a Major clinical response is defined as achieving an ACR70 response for a continuous six month period
b p<0.05, HUMIRA/MTX vs. MTX for ACR 20
p<0.001, HUMIRA/MTX vs. MTX for ACR 50 and 70, and Major Clinical Response
c p<0.001, HUMIRA/MTX vs. HUMIRA

At Week 52, all individual components of the ACR response criteria for Study RA-V improved in the HUMIRA/MTX group and improvements were maintained to Week 104.

Radiographic Response

In Study RA-III, structural joint damage was assessed radiographically and expressed as change in Total Sharp Score (TSS) and its components, the erosion score and Joint Space Narrowing (JSN) score, at month 12 compared to baseline. At baseline, the median TSS was approximately 55 in the placebo and 40 mg every other week groups. The results are shown in Table 6. HUMIRA/MTX treated subjects demonstrated less radiographic progression than subjects receiving MTX alone at 52 weeks.

Table 6. Radiographic Mean Changes Over 12 Months in Study RA-III
 | Placebo/MTX | HUMIRA/MTX 40 mg every other week | Placebo/MTX- HUMIRA/MTX (95% Confidence Interval*) | P-value**
Total Sharp score | 2.7 | 0.1 | 2.6 (1.4, 3.8) | <0.001
Erosion score | 1.6 | 0.0 | 1.6 (0.9, 2.2) | <0.001
JSN score | 1.0 | 0.1 | 0.9 (0.3, 1.4) | 0.002
*95% confidence intervals for the differences in change scores between MTX and HUMIRA.
**Based on rank analysis

In the open-label extension of Study RA-III, 77% of the original subjects treated with any dose of HUMIRA were evaluated radiographically at 2 years. Subjects maintained inhibition of structural damage, as measured by the TSS. Fifty-four percent had no progression of structural damage as defined by a change in the TSS of zero or less. Fifty-five percent (55%) of subjects originally treated with 40 mg HUMIRA every other week have been evaluated radiographically at 5 years. Subjects had continued inhibition of structural damage with 50% showing no progression of structural damage defined by a change in the TSS of zero or less.

In Study RA-V, structural joint damage was assessed as in Study RA-III. Greater inhibition of radiographic progression, as assessed by changes in TSS, erosion score and JSN was observed in the HUMIRA/MTX combination group as compared to either the MTX or HUMIRA monotherapy group at Week 52 as well as at Week 104 (see Table 7).

Table 7. Radiographic Mean Change* in Study RA-V
 |  | MTXa N=257 | HUMIRAa,b N=274 | HUMIRA/MTX N=268
52 Weeks | Total Sharp score | 5.7 (4.2, 7.3) | 3.0 (1.7, 4.3) | 1.3 (0.5, 2.1)
 | Erosion score | 3.7 (2.7, 4.8) | 1.7 (1.0, 2.4) | 0.8 (0.4, 1.2)
 | JSN score | 2.0 (1.2, 2.8) | 1.3 (0.5, 2.1) | 0.5 (0.0, 1.0)
104 Weeks | Total Sharp score | 10.4 (7.7, 13.2) | 5.5 (3.6, 7.4) | 1.9 (0.9, 2.9)
 | Erosion score | 6.4 (4.6, 8.2) | 3.0 (2.0, 4.0) | 1.0 (0.4, 1.6)
 | JSN score | 4.1 (2.7, 5.4) | 2.6 (1.5, 3.7) | 0.9 (0.3, 1.5)
* mean (95% confidence interval)
a p<0.001, HUMIRA/MTX vs. MTX at 52 and 104 weeks and for HUMIRA/MTX vs. HUMIRA at 104 weeks
b p<0.01, for HUMIRA/MTX vs. HUMIRA at 52 weeks

Physical Function Response

In studies RA-I through IV, HUMIRA showed significantly greater improvement than placebo in the disability index of Health Assessment Questionnaire (HAQ-DI) from baseline to the end of study, and significantly greater improvement than placebo in the health-outcomes as assessed by The Short Form Health Survey (SF 36). Improvement was seen in both the Physical Component Summary (PCS) and the Mental Component Summary (MCS).

In Study RA-III, the mean (95% CI) improvement in HAQ-DI from baseline at week 52 was 0.60 (0.55, 0.65) for the HUMIRA subjects and 0.25 (0.17, 0.33) for placebo/MTX (p<0.001) subjects. Sixty-three percent of HUMIRA-treated subjects achieved a 0.5 or greater improvement in HAQ-DI at week 52 in the double-blind portion of the study. Eighty-two percent of these subjects maintained that improvement through week 104 and a similar proportion of subjects maintained this response through week 260 (5 years) of open-label treatment. Mean improvement in the SF-36 was maintained through the end of measurement at week 156 (3 years).

In Study RA-V, the HAQ-DI and the physical component of the SF-36 showed greater improvement (p<0.001) for the HUMIRA/MTX combination therapy group versus either the MTX monotherapy or the HUMIRA monotherapy group at Week 52, which was maintained through Week 104.

14.2 Clinical Studies in Juvenile Idiopathic Arthritis

The safety and efficacy of HUMIRA was assessed in two studies (Studies JIA-I and JIA-II) in subjects with active polyarticular juvenile idiopathic arthritis (JIA).

Study JIA-I

The safety and efficacy of HUMIRA were assessed in a multicenter, randomized, withdrawal, double-blind, parallel-group study in 171 subjects who were 4 to 17 years of age with polyarticular JIA. In the study, the subjects were stratified into two groups: MTX-treated or non-MTX-treated. All subjects had to show signs of active moderate or severe disease despite previous treatment with NSAIDs, analgesics, corticosteroids, or DMARDS. Subjects who received prior treatment with any biologic DMARDS were excluded from the study.

The study included four phases: an open-label lead in phase (OL-LI; 16 weeks), a double-blind randomized withdrawal phase (DB; 32 weeks), an open-label extension phase (OLE-BSA; up to 136 weeks), and an open-label fixed dose phase (OLE-FD; 16 weeks). In the first three phases of the study, HUMIRA was administered based on body surface area at a dose of 24 mg/m^2 up to a maximum total body dose of 40 mg subcutaneously (SC) every other week. In the OLE-FD phase, the subjects were treated with 20 mg of HUMIRA SC every other week if their weight was less than 30 kg and with 40 mg of HUMIRA SC every other week if their weight was 30 kg or greater. Subjects remained on stable doses of NSAIDs and or prednisone (≤0.2 mg/kg/day or 10 mg/day maximum).

Subjects demonstrating a Pediatric ACR 30 response at the end of OL-LI phase were randomized into the double blind (DB) phase of the study and received either HUMIRA or placebo every other week for 32 weeks or until disease flare. Disease flare was defined as a worsening of ≥30% from baseline in ≥3 of 6 Pediatric ACR core criteria, ≥2 active joints, and improvement of >30% in no more than 1 of the 6 criteria. After 32 weeks or at the time of disease flare during the DB phase, subjects were treated in the open-label extension phase based on the BSA regimen (OLE-BSA), before converting to a fixed dose regimen based on body weight (OLE-FD phase).

Study JIA-I Clinical Response

At the end of the 16-week OL-LI phase, 94% of the subjects in the MTX stratum and 74% of the subjects in the non-MTX stratum were Pediatric ACR 30 responders. In the DB phase significantly fewer subjects who received HUMIRA experienced disease flare compared to placebo, both without MTX (43% vs. 71%) and with MTX (37% vs. 65%). More subjects treated with HUMIRA continued to show pediatric ACR 30/50/70 responses at Week 48 compared to subjects treated with placebo. Pediatric ACR responses were maintained for up to two years in the OLE phase in subjects who received HUMIRA throughout the study.

Study JIA-II

HUMIRA was assessed in an open-label, multicenter study in 32 subjects who were 2 to <4 years of age or 4 years of age and older weighing <15 kg with moderately to severely active polyarticular JIA. Most subjects (97%) received at least 24 weeks of HUMIRA treatment dosed 24 mg/m^2 up to a maximum of 20 mg every other week as a single SC injection up to a maximum of 120 weeks duration. During the study, most subjects used concomitant MTX, with fewer reporting use of corticosteroids or NSAIDs. The primary objective of the study was evaluation of safety [see Adverse Reactions (6.1)].

14.3 Clinical Studies in Psoriatic Arthritis

The safety and efficacy of HUMIRA was assessed in two randomized, double-blind, placebo-controlled studies in 413 subjects with psoriatic arthritis (PsA). Upon completion of both studies, 383 subjects enrolled in an open-label extension study, in which 40 mg HUMIRA was administered every other week.

Study PsA-I enrolled 313 adult subjects with moderately to severely active PsA (>3 swollen and >3 tender joints) who had an inadequate response to NSAID therapy in one of the following forms: (1) distal interphalangeal (DIP) involvement (N=23); (2) polyarticular arthritis (absence of rheumatoid nodules and presence of plaque psoriasis) (N=210); (3) arthritis mutilans (N=1); (4) asymmetric PsA (N=77); or (5) AS-like (N=2). Subjects on MTX therapy (158 of 313 subjects) at enrollment (stable dose of ≤30 mg/week for >1 month) could continue MTX at the same dose. Doses of HUMIRA 40 mg or placebo every other week were administered during the 24-week double-blind period of the study.

Compared to placebo, treatment with HUMIRA resulted in improvements in the measures of disease activity (see Tables 8 and 9). Among subjects with PsA who received HUMIRA, the clinical responses were apparent in some subjects at the time of the first visit (two weeks) and were maintained up to 88 weeks in the ongoing open-label study. Similar responses were seen in subjects with each of the subtypes of psoriatic arthritis, although few subjects were enrolled with the arthritis mutilans and ankylosing spondylitis-like subtypes. Responses were similar in subjects who were or were not receiving concomitant MTX therapy at baseline.

Subjects with psoriatic involvement of at least three percent body surface area (BSA) were evaluated for Psoriatic Area and Severity Index (PASI) responses. At 24 weeks, the proportions of subjects achieving a 75% or 90% improvement in the PASI were 59% and 42% respectively, in the HUMIRA group (N=69), compared to 1% and 0% respectively, in the placebo group (N=69) (p<0.001). PASI responses were apparent in some subjects at the time of the first visit (two weeks). Responses were similar in subjects who were or were not receiving concomitant MTX therapy at baseline.

Table 8. ACR Response in Study PsA-I (Percent of Subjects)
 | Placebo N=162 | HUMIRA* N=151
ACR20 Week 12 Week 24 | 14% 15% | 58% 57%
ACR50 Week 12 Week 24 | 4% 6% | 36% 39%
ACR70 Week 12 Week 24 | 1% 1% | 20% 23%
* p<0.001 for all comparisons between HUMIRA and placebo

Table 9. Components of Disease Activity in Study PsA-I
 | Placebo N=162 |  | HUMIRA* N=151
Parameter: median | Baseline | 24 weeks | Baseline | 24 weeks
Number of tender jointsa | 23.0 | 17.0 | 20.0 | 5.0
Number of swollen jointsb | 11.0 | 9.0 | 11.0 | 3.0
Physician global assessmentc | 53.0 | 49.0 | 55.0 | 16.0
Patient global assessmentc | 49.5 | 49.0 | 48.0 | 20.0
Painc | 49.0 | 49.0 | 54.0 | 20.0
Disability index (HAQ) d | 1.0 | 0.9 | 1.0 | 0.4
CRP (mg/dL)e | 0.8 | 0.7 | 0.8 | 0.2
* p<0.001 for HUMIRA vs. placebo comparisons based on median changes
a Scale 0-78
b Scale 0-76
c Visual analog scale; 0=best, 100=worst
d Disability Index of the Health Assessment Questionnaire; 0=best, 3=worst; measures the patient’s ability to perform the following: dress/groom, arise, eat, walk, reach, grip, maintain hygiene, and maintain daily activity.
e Normal range: 0-0.287 mg/dL

Similar results were seen in an additional, 12-week study in 100 subjects with moderate to severe psoriatic arthritis who had suboptimal response to DMARD therapy as manifested by ≥3 tender joints and ≥3 swollen joints at enrollment.

Radiographic Response

Radiographic changes were assessed in the PsA studies. Radiographs of hands, wrists, and feet were obtained at baseline and Week 24 during the double-blind period when subjects were on HUMIRA or placebo and at Week 48 when all subjects were on open-label HUMIRA. A modified Total Sharp Score (mTSS), which included distal interphalangeal joints (i.e., not identical to the TSS used for rheumatoid arthritis), was used by readers blinded to treatment group to assess the radiographs.

HUMIRA-treated subjects demonstrated greater inhibition of radiographic progression compared to placebo-treated subjects and this effect was maintained at 48 weeks (see Table 10).

Table 10. Change in Modified Total Sharp Score in Psoriatic Arthritis
 | Placebo N=141 | HUMIRA N=133
 | Week 24 | Week 24 | Week 48
Baseline mean | 22.1 | 23.4 | 23.4
Mean Change ± SD | 0.9 ± 3.1 | -0.1 ± 1.7 | -0.2 ± 4.9*
* <0.001 for the difference between HUMIRA, Week 48 and Placebo, Week 24 (primary analysis)

Physical Function Response

In Study PsA-I, physical function and disability were assessed using the HAQ Disability Index (HAQ-DI) and the SF-36 Health Survey. Subjects treated with 40 mg of HUMIRA every other week showed greater improvement from baseline in the HAQ-DI score (mean decreases of 47% and 49% at Weeks 12 and 24 respectively) in comparison to placebo (mean decreases of 1% and 3% at Weeks 12 and 24 respectively). At Weeks 12 and 24, subjects treated with HUMIRA showed greater improvement from baseline in the SF-36 Physical Component Summary score compared to subjects treated with placebo, and no worsening in the SF-36 Mental Component Summary score. Improvement in physical function based on the HAQ-DI was maintained for up to 84 weeks through the open-label portion of the study.

14.4 Clinical Studies in Ankylosing Spondylitis

The safety and efficacy of HUMIRA 40 mg every other week was assessed in 315 adult subjects in a randomized, 24 week double-blind, placebo-controlled study in subjects with active ankylosing spondylitis (AS) who had an inadequate response to glucocorticoids, NSAIDs, analgesics, methotrexate or sulfasalazine. Active AS was defined as subjects who fulfilled at least two of the following three criteria: (1) a Bath AS disease activity index (BASDAI) score ≥4 cm, (2) a visual analog score (VAS) for total back pain ≥ 40 mm, and (3) morning stiffness ≥ 1 hour. The blinded period was followed by an open-label period during which subjects received HUMIRA 40 mg every other week subcutaneously for up to an additional 28 weeks.

Improvement in measures of disease activity was first observed at Week 2 and maintained through 24 weeks as shown in Figure 2 and Table 11.

Responses of subjects with total spinal ankylosis (n=11) were similar to those without total ankylosis.

Figure 2. ASAS 20 Response By Visit, Study AS-I

At 12 weeks, the ASAS 20/50/70 responses were achieved by 58%, 38%, and 23%, respectively, of subjects receiving HUMIRA, compared to 21%, 10%, and 5% respectively, of subjects receiving placebo (p <0.001). Similar responses were seen at Week 24 and were sustained in subjects receiving open-label HUMIRA for up to 52 weeks.

A greater proportion of subjects treated with HUMIRA (22%) achieved a low level of disease activity at 24 weeks (defined as a value <20 [on a scale of 0 to 100 mm] in each of the four ASAS response parameters) compared to subjects treated with placebo (6%).

Table 11. Components of Ankylosing Spondylitis Disease Activity
 | Placebo N=107 |  | HUMIRA N=208
 | Baseline mean | Week 24 mean | Baseline mean | Week 24 mean
ASAS 20 Response Criteria*
Patient’s Global Assessment of Disease Activitya* | 65 | 60 | 63 | 38
Total back pain* | 67 | 58 | 65 | 37
Inflammationb* | 6.7 | 5.6 | 6.7 | 3.6
BASFIc* | 56 | 51 | 52 | 34
BASDAId score* | 6.3 | 5.5 | 6.3 | 3.7
BASMIe score* | 4.2 | 4.1 | 3.8 | 3.3
Tragus to wall (cm) | 15.9 | 15.8 | 15.8 | 15.4
Lumbar flexion (cm) | 4.1 | 4.0 | 4.2 | 4.4
Cervical rotation (degrees) | 42.2 | 42.1 | 48.4 | 51.6
Lumbar side flexion (cm) | 8.9 | 9.0 | 9.7 | 11.7
Intermalleolar distance (cm) | 92.9 | 94.0 | 93.5 | 100.8
CRPf* | 2.2 | 2.0 | 1.8 | 0.6
a Percent of subjects with at least a 20% and 10-unit improvement measured on a Visual Analog Scale (VAS) with 0 = “none” and 100 = “severe”
b mean of questions 5 and 6 of BASDAI (defined in ‘d’)
c Bath Ankylosing Spondylitis Functional Index
d Bath Ankylosing Spondylitis Disease Activity Index
e Bath Ankylosing Spondylitis Metrology Index
f C-Reactive Protein (mg/dL)
* statistically significant for comparisons between HUMIRA and placebo at Week 24

A second randomized, multicenter, double-blind, placebo-controlled study of 82 subjects with ankylosing spondylitis showed similar results.

Subjects treated with HUMIRA achieved improvement from baseline in the Ankylosing Spondylitis Quality of Life Questionnaire (ASQoL) score (-3.6 vs. -1.1) and in the Short Form Health Survey (SF-36) Physical Component Summary (PCS) score (7.4 vs. 1.9) compared to placebo-treated subjects at Week 24.

14.5 Clinical Studies in Adults with Crohn’s Disease

The safety and efficacy of multiple doses of HUMIRA were assessed in adult subjects with moderately to severely active Crohn’s disease, CD, (Crohn’s Disease Activity Index (CDAI) ≥ 220 and ≤ 450) in randomized, double-blind, placebo-controlled studies. Concomitant stable doses of aminosalicylates, corticosteroids, and/or immunomodulatory agents were permitted, and 79% of subjects continued to receive at least one of these medications.

Induction of clinical remission (defined as CDAI < 150) was evaluated in two studies. In Study CD-I, 299 TNF-blocker naïve subjects were randomized to one of four treatment groups: the placebo group received placebo at Weeks 0 and 2, the 160/80 group received 160 mg HUMIRA at Week 0 and 80 mg at Week 2, the 80/40 group received 80 mg at Week 0 and 40 mg at Week 2, and the 40/20 group received 40 mg at Week 0 and 20 mg at Week 2. Clinical results were assessed at Week 4.

In the second induction study, Study CD-II, 325 subjects who had lost response to, or were intolerant to, previous infliximab therapy were randomized to receive either 160 mg HUMIRA at Week 0 and 80 mg at Week 2, or placebo at Weeks 0 and 2. Clinical results were assessed at Week 4.

Maintenance of clinical remission was evaluated in Study CD-III. In this study, 854 subjects with active disease received open-label HUMIRA, 80 mg at week 0 and 40 mg at Week 2. Subjects were then randomized at Week 4 to 40 mg HUMIRA every other week, 40 mg HUMIRA every week, or placebo. The total study duration was 56 weeks. Subjects in clinical response (decrease in CDAI ≥70) at Week 4 were stratified and analyzed separately from those not in clinical response at Week 4.

Induction of Clinical Remission

A greater percentage of the subjects treated with 160/80 mg HUMIRA achieved induction of clinical remission versus placebo at Week 4 regardless of whether the subjects were TNF blocker naïve (CD-I), or had lost response to or were intolerant to infliximab (CD-II) (see Table 12).

Table 12. Induction of Clinical Remission in Studies CD-I and CD-II (Percent of Subjects)
 | CD-I |  | CD-II
 | Placebo N=74 | HUMIRA 160/80 mg N=76 | Placebo N=166 | HUMIRA 160/80 mg N=159
Week 4
Clinical remission | 12% | 36%* | 7% | 21%*
Clinical response | 34% | 58%** | 34% | 52%**
Clinical remission is CDAI score < 150; clinical response is decrease in CDAI of at least 70 points.
* p<0.001 for HUMIRA vs. placebo pairwise comparison of proportions
** p<0.01 for HUMIRA vs. placebo pairwise comparison of proportions

Maintenance of Clinical Remission

In Study CD-III at Week 4, 58% (499/854) of subjects were in clinical response and were assessed in the primary analysis. At Weeks 26 and 56, greater proportions of subjects who were in clinical response at Week 4 achieved clinical remission in the HUMIRA 40 mg every other week maintenance group compared to subjects in the placebo maintenance group (see Table 13). The group that received HUMIRA therapy every week did not demonstrate significantly higher remission rates compared to the group that received HUMIRA every other week.

Table 13. Maintenance of Clinical Remission in CD-III (Percent of Subjects)
 | Placebo | 40 mg HUMIRA every other week
 | N=170 | N=172
Week 26
Clinical remission | 17% | 40%*
Clinical response | 28% | 54%*
Week 56
Clinical remission | 12% | 36%*
Clinical response | 18% | 43%*
Clinical remission is CDAI score < 150; clinical response is decrease in CDAI of at least 70 points.
*p<0.001 for HUMIRA vs. placebo pairwise comparisons of proportions

Of those in response at Week 4 who attained remission during the study, subjects in the HUMIRA every other week group maintained remission for a longer time than subjects in the placebo maintenance group. Among subjects who were not in response by Week 12, therapy continued beyond 12 weeks did not result in significantly more responses.

14.6 Clinical Studies in Pediatric Subjects with Crohn’s Disease

A randomized, double-blind, 52-week clinical study of 2 dose concentrations of HUMIRA (Study PCD-I) was conducted in 192 pediatric subjects (6 to 17 years of age) with moderately to severely active Crohn’s disease (defined as Pediatric Crohn’s Disease Activity Index (PCDAI) score > 30). Enrolled subjects had over the previous two-year period an inadequate response to corticosteroids or an immunomodulator (i.e., azathioprine, 6-mercaptopurine, or methotrexate). Subjects who had previously received a TNF blocker were allowed to enroll if they had previously had loss of response or intolerance to that TNF blocker.

Subjects received open-label induction therapy at a dose based on their body weight (≥40 kg and <40 kg). Subjects weighing ≥40 kg received 160 mg (at Week 0) and 80 mg (at Week 2). Subjects weighing <40 kg received 80 mg (at Week 0) and 40 mg (at Week 2). At Week 4, subjects within each body weight category (≥40 kg and <40 kg) were randomized 1:1 to one of two maintenance dose regimens (high dose and low dose). The high dose was 40 mg every other week for subjects weighing ≥40 kg and 20 mg every other week for subjects weighing <40 kg. The low dose was 20 mg every other week for subjects weighing ≥40 kg and 10 mg every other week for subjects weighing <40 kg.

Concomitant stable dosages of corticosteroids (prednisone dosage ≤40 mg/day or equivalent) and immunomodulators (azathioprine, 6-mercaptopurine, or methotrexate) were permitted throughout the study.

At Week 12, subjects who experienced a disease flare (increase in PCDAI of ≥ 15 from Week 4 and absolute PCDAI > 30) or who were non-responders (did not achieve a decrease in the PCDAI of ≥ 15 from baseline for 2 consecutive visits at least 2 weeks apart) were allowed to dose-escalate (i.e., switch from blinded every other week dosing to blinded every week dosing); subjects who dose-escalated were considered treatment failures.

At baseline, 38% of subjects were receiving corticosteroids, and 62% of subjects were receiving an immunomodulator. Forty-four percent (44%) of subjects had previously lost response or were intolerant to a TNF blocker. The median baseline PCDAI score was 40.

Of the 192 subjects total, 188 subjects completed the 4 week induction period, 152 subjects completed 26 weeks of treatment, and 124 subjects completed 52 weeks of treatment. Fifty-one percent (51%) (48/95) of subjects in the low maintenance dose group dose-escalated, and 38% (35/93) of subjects in the high maintenance dose group dose-escalated.

At Week 4, 28% (52/188) of subjects were in clinical remission (defined as PCDAI ≤ 10).

The proportions of subjects in clinical remission (defined as PCDAI ≤ 10) and clinical response (defined as reduction in PCDAI of at least 15 points from baseline) were assessed at Weeks 26 and 52.

At both Weeks 26 and 52, the proportion of subjects in clinical remission and clinical response was numerically higher in the high dose group compared to the low dose group (Table 14). The recommended maintenance regimen is 20 mg every other week for subjects weighing < 40 kg and 40 mg every other week for subjects weighing ≥ 40 kg. Every week dosing is not the recommended maintenance dosing regimen [see Dosage and Administration (2.3)].

Table 14. Clinical Remission and Clinical Response in Study PCD-I
 | Low Maintenance Dose† (20 or 10 mg every other week) N = 95 | High Maintenance Dose# (40 or 20 mg every other week) N = 93
Week 26
Clinical Remission‡ | 28% | 39%
Clinical Response§ | 48% | 59%
Week 52
Clinical Remission‡ | 23% | 33%
Clinical Response§ | 28% | 42%
†The low maintenance dose was 20 mg every other week for subjects weighing ≥ 40 kg and 10 mg every other week for subjects weighing < 40 kg.
#The high maintenance dose was 40 mg every other week for subjects weighing ≥ 40 kg and 20 mg every other week for subjects weighing < 40 kg.
‡Clinical remission defined as PCDAI ≤ 10.
§Clinical response defined as reduction in PCDAI of at least 15 points from baseline.

14.7 Clinical Studies in Adults with Ulcerative Colitis

The safety and efficacy of HUMIRA were assessed in adult subjects with moderately to severely active ulcerative colitis (Mayo score 6 to 12 on a 12 point scale, with an endoscopy subscore of 2 to 3 on a scale of 0 to 3) despite concurrent or prior treatment with immunosuppressants such as corticosteroids, azathioprine, or 6-MP in two randomized, double-blind, placebo-controlled clinical studies (Studies UC-I and UC-II). Both studies enrolled TNF-blocker naïve subjects, but Study UC-II also allowed entry of subjects who lost response to or were intolerant to TNF-blockers. Forty percent (40%) of subjects enrolled in Study UC-II had previously used another TNF-blocker.

Concomitant stable doses of aminosalicylates and immunosuppressants were permitted. In Studies UC-I and II, subjects were receiving aminosalicylates (69%), corticosteroids (59%) and/or azathioprine or 6-MP (37%) at baseline. In both studies, 92% of subjects received at least one of these medications.

Induction of clinical remission (defined as Mayo score ≤ 2 with no individual subscores > 1) at Week 8 was evaluated in both studies. Clinical remission at Week 52 and sustained clinical remission (defined as clinical remission at both Weeks 8 and 52) were evaluated in Study UC-II.

In Study UC-I, 390 TNF-blocker naïve subjects were randomized to one of three treatment groups for the primary efficacy analysis. The placebo group received placebo at Weeks 0, 2, 4 and 6. The 160/80 group received 160 mg HUMIRA at Week 0 and 80 mg at Week 2, and the 80/40 group received 80 mg HUMIRA at Week 0 and 40 mg at Week 2. After Week 2, subjects in both HUMIRA treatment groups received 40 mg every other week.

In Study UC-II, 518 subjects were randomized to receive either HUMIRA 160 mg at Week 0, 80 mg at Week 2, and 40 mg every other week starting at Week 4 through Week 50, or placebo starting at Week 0 and every other week through Week 50. Corticosteroid taper was permitted starting at Week 8.

In both Studies UC-I and UC-II, a greater percentage of the subjects treated with 160/80 mg of HUMIRA compared to subjects treated with placebo achieved induction of clinical remission. In Study UC-II, a greater percentage of the subjects treated with 160/80 mg of HUMIRA compared to subjects treated with placebo achieved sustained clinical remission (clinical remission at both Weeks 8 and 52) (Table 15).

Table 15. Induction of Clinical Remission in Studies UC-I and UC-II and Sustained Clinical Remission in Study UC-II (Percent of Subjects)
 | Study UC-I |  |  | Study UC-II
 | Placebo N=130 | HUMIRA 160/80 mg N=130 | Treatment Difference (95% CI) | Placebo N=246 | HUMIRA 160/80 mg N=248 | Treatment Difference (95% CI)
Induction of Clinical Remission (Clinical Remission at Week 8) | 9.2% | 18.5% | 9.3%* (0.9%, 17.6%) | 9.3% | 16.5% | 7.2%* (1.2%, 12.9%)
Sustained Clinical Remission (Clinical Remission at both Weeks 8 and 52) | N/A | N/A | N/A | 4.1% | 8.5% | 4.4%* (0.1%, 8.6%)
Clinical remission is defined as Mayo score ≤ 2 with no individual subscores > 1.
CI=Confidence interval
* p<0.05 for HUMIRA vs. placebo pairwise comparison of proportions

In Study UC-I, there was no statistically significant difference in clinical remission observed between the HUMIRA 80/40 mg group and the placebo group at Week 8.

In Study UC-II, 17.3% (43/248) in the HUMIRA group were in clinical remission at Week 52 compared to 8.5% (21/246) in the placebo group (treatment difference: 8.8%; 95% confidence interval (CI): [2.8%, 14.5%]; p<0.05).

In the subgroup of subjects in Study UC-II with prior TNF-blocker use, the treatment difference for induction of clinical remission appeared to be lower than that seen in the whole study population, and the treatment differences for sustained clinical remission and clinical remission at Week 52 appeared to be similar to those seen in the whole study population. The subgroup of subjects with prior TNF-blocker use achieved induction of clinical remission at 9% (9/98) in the HUMIRA group versus 7% (7/101) in the placebo group, and sustained clinical remission at 5% (5/98) in the HUMIRA group versus 1% (1/101) in the placebo group. In the subgroup of subjects with prior TNF-blocker use, 10% (10/98) were in clinical remission at Week 52 in the HUMIRA group versus 3% (3/101) in the placebo group.

14.8 Clinical Studies in Pediatric Subjects with Ulcerative Colitis

The safety and efficacy of HUMIRA were assessed in a multicenter, randomized, double-blind trial (Study PUC-I, NCT02065557) in 93 pediatric subjects 5 years to 17 years of age with moderately to severely active ulcerative colitis (Mayo score 6 to 12 with endoscopy subscore of 2 to 3 points, confirmed by centrally read endoscopy) who had an inadequate response or intolerance to therapy with corticosteroids and/or an immunomodulator (i.e., azathioprine, 6-mercaptopurine, or methotrexate). Fifteen out of 93 subjects (16%) in the study had prior experience with a TNF blocker. Subjects who received corticosteroids at enrollment were allowed to taper their corticosteroid therapy after Week 4.

Seventy-seven subjects were initially randomized 3:2 to receive double-blind treatment with one of two dosages of HUMIRA. Subjects in both dosage groups received 2.4 mg/kg (maximum of 160 mg) at Week 0, 1.2 mg/kg (maximum of 80 mg) at Week 2, and 0.6 mg/kg (maximum of 40 mg) at Weeks 4 and 6. The higher dosage group also received an additional dosage of 2.4 mg/kg (maximum of 160 mg) at Week 1. Following an amendment to the study design, 16 additional subjects were enrolled and received open-label treatment with HUMIRA at the higher dosage.

At Week 8, 62 subjects who demonstrated clinical response per Partial Mayo Score (PMS; a subset of the Mayo score with no endoscopic component and defined as a decrease in PMS ≥ 2 points and ≥ 30% from baseline) were randomized equally to receive double-blind treatment with HUMIRA 0.6 mg/kg (maximum of 40 mg) every other week (lower dosage group), or 0.6 mg/kg (maximum of 40 mg) every week (higher dosage group). Prior to an amendment to the study design, 12 additional subjects who demonstrated clinical response per PMS were randomized to receive placebo.

There are no anticipated clinically relevant differences in efficacy between the studied higher dosage administered during the 52-week PUC-I trial and the recommended dosage of HUMIRA [see Dosage and Administration (2.4), Clinical Pharmacology (12.2)].

Subjects who met criteria for disease flare at or after Week 12 were randomized to receive a re-induction dose of 2.4 mg/kg (maximum of 160 mg) or a dose of 0.6 mg/kg (maximum of 40 mg) and then continued the dose to which they were randomized at Week 8.

The co-primary endpoints of the study were clinical remission per PMS (defined as PMS ≤ 2 and no individual subscore > 1) at Week 8, and clinical remission per the Mayo Score (defined as Mayo Score ≤ 2 and no individual subscore > 1) at Week 52 in subjects who achieved clinical response per PMS at Week 8. Secondary endpoints included Mayo Score response (defined as a decrease in Mayo Score of ≥ 3 points and ≥ 30% from baseline) at Week 52 in Week 8 PMS responders, endoscopic improvement (defined as a Mayo endoscopy subscore ≤ 1) at Week 52 in Week 8 PMS responders, and Mayo Score remission at Week 52 in Week 8 PMS remitters.

Week 8 Results

At Week 8, PMS remission was achieved by 60% [28/47; 95% confidence interval (CI): (44%, 74%)] of subjects in the higher dosage group (not including the 16 subjects receiving open-label higher dosage) and 43% [13/30; 95% CI: (25%, 63%)] of subjects in the lower dosage group. Results from the higher dosage group are representative of the results expected with the recommended dosage [see Dosage and Administration (2.4), Clinical Pharmacology (12.2)].

Week 52 Results

At Week 52, endpoints were assessed in the population of subjects who received double-blind placebo, HUMIRA 0.6 mg/kg (maximum of 40 mg) every other week, or HUMIRA 0.6 mg/kg (maximum of 40 mg) every week between Week 8 and Week 52 (Table 16).

Table 16. Clinical Remission, Clinical Response and Endoscopic Improvement at Week 52 in Pediatric Subjects with Ulcerative Colitis (Study PUC-1)
 | Placeboa n/N (%), 95% CI | HUMIRA Maximum of 40 mg (0.6 mg/kg) every other weekb n/N (%), 95% CI | HUMIRA Maximum of 40 mg (0.6 mg/kg) every weekc n/N (%), 95% CI
Clinical remission in Week 8 PMS responders | 4/12 (33%) (10%, 65%) | 9/31 (29%) (14%, 48%) | 14/31 (45%) (27%, 64%)
Clinical response in Week 8 PMS responders | 4/12 (33%) (10%, 65%) | 19/31 (61%) (42%, 78%) | 21/31 (68%) (49%, 83%)
Endoscopic improvement in Week 8 PMS responders | 4/12 (33%) (10%, 65%) | 12/31 (39%) (22%, 58%) | 16/31 (52%) (33%, 70%)
Clinical remission in Week 8 PMS remitters | 3/8 (38%) (9%, 76%) | 9/21 (43%) (22%, 66%) | 10/22 (45%) (24%, 68%)
CI=Confidence interval
a Twelve subjects who demonstrated clinical response per PMS at Week 8 were randomized to receive placebo. There are limitations to the interpretability of the placebo data due to the small sample size.
b The every other week dosage studied during the 52-week PUC-I trial is a lower dosage than the recommended dosage of HUMIRA [see Dosage and Administration (2.4)].
c There are no anticipated clinically relevant differences in efficacy between the studied higher dosage administered during the 52-week PUC-I trial and the recommended dosage of HUMIRA.
Note: Subjects with missing values at Week 52 or who were randomized to receive re-induction or maintenance treatment due to disease flare were considered non-responders for Week 52 endpoints.

14.9 Clinical Studies in Plaque Psoriasis

The safety and efficacy of HUMIRA were assessed in randomized, double-blind, placebo-controlled studies in 1696 adult subjects with moderate to severe chronic plaque psoriasis (Ps) who were candidates for systemic therapy or phototherapy.

Study Ps-I evaluated 1212 subjects with chronic Ps with ≥10% body surface area (BSA) involvement, Physician’s Global Assessment (PGA) of at least moderate disease severity, and Psoriasis Area and Severity Index (PASI) ≥12 within three treatment periods. In period A, subjects received placebo or HUMIRA at an initial dose of 80 mg at Week 0 followed by a dose of 40 mg every other week starting at Week 1. After 16 weeks of therapy, subjects who achieved at least a PASI 75 response at Week 16, defined as a PASI score improvement of at least 75% relative to baseline, entered period B and received open-label 40 mg HUMIRA every other week. After 17 weeks of open label therapy, subjects who maintained at least a PASI 75 response at Week 33 and were originally randomized to active therapy in period A were re-randomized in period C to receive 40 mg HUMIRA every other week or placebo for an additional 19 weeks. Across all treatment groups the mean baseline PASI score was 19 and the baseline Physician’s Global Assessment score ranged from “moderate” (53%) to “severe” (41%) to “very severe” (6%).

Study Ps-II evaluated 99 subjects randomized to HUMIRA and 48 subjects randomized to placebo with chronic plaque psoriasis with ≥10% BSA involvement and PASI ≥12. Subjects received placebo, or an initial dose of 80 mg HUMIRA at Week 0 followed by 40 mg every other week starting at Week 1 for 16 weeks. Across all treatment groups the mean baseline PASI score was 21 and the baseline PGA score ranged from “moderate” (41%) to “severe” (51%) to “very severe” (8%).

Studies Ps-I and II evaluated the proportion of subjects who achieved “clear” or “minimal” disease on the 6-point PGA scale and the proportion of subjects who achieved a reduction in PASI score of at least 75% (PASI 75) from baseline at Week 16 (see Table 17 and 18).

Additionally, Study Ps-I evaluated the proportion of subjects who maintained a PGA of “clear” or “minimal” disease or a PASI 75 response after Week 33 and on or before Week 52.

Table 17. Efficacy Results at 16 Weeks in Study Ps-I Number of Subjects (%)
 | HUMIRA 40 mg every other week | Placebo
 | N = 814 | N = 398
PGA: Clear or minimal* | 506 (62%) | 17 (4%)
PASI 75 | 578 (71%) | 26 (7%)
* Clear = no plaque elevation, no scale, plus or minus hyperpigmentation or diffuse pink or red coloration
Minimal = possible but difficult to ascertain whether there is slight elevation of plaque above normal skin, plus or minus surface dryness with some white coloration, plus or minus up to red coloration

Table 18. Efficacy Results at 16 Weeks in Study Ps-II Number of Subjects (%)
 | HUMIRA 40 mg every other week | Placebo
 | N = 99 | N = 48
PGA: Clear or minimal* | 70 (71%) | 5 (10%)
PASI 75 | 77 (78%) | 9 (19%)
* Clear = no plaque elevation, no scale, plus or minus hyperpigmentation or diffuse pink or red coloration
Minimal = possible but difficult to ascertain whether there is slight elevation of plaque above normal skin, plus or minus surface dryness with some white coloration, plus or minus up to red coloration

Additionally, in Study Ps-I, subjects on HUMIRA who maintained a PASI 75 were re-randomized to HUMIRA (N = 250) or placebo (N = 240) at Week 33. After 52 weeks of treatment with HUMIRA, more subjects on HUMIRA maintained efficacy when compared to subjects who were re-randomized to placebo based on maintenance of PGA of “clear” or “minimal” disease (68% vs. 28%) or a PASI 75 (79% vs. 43%).

A total of 347 stable responders participated in a withdrawal and retreatment evaluation in an open-label extension study. Median time to relapse (decline to PGA “moderate” or worse) was approximately 5 months. During the withdrawal period, no subject experienced transformation to either pustular or erythrodermic psoriasis. A total of 178 subjects who relapsed re-initiated treatment with 80 mg of HUMIRA, then 40 mg every other week beginning at week 1. At week 16, 69% (123/178) of subjects had a response of PGA “clear” or “minimal”.

A randomized, double-blind study (Study Ps-III) compared the efficacy and safety of HUMIRA versus placebo in 217 adult subjects. Subjects in the study had to have chronic plaque psoriasis of at least moderate severity on the PGA scale, fingernail involvement of at least moderate severity on a 5-point Physician’s Global Assessment of Fingernail Psoriasis (PGA-F) scale, a Modified Nail Psoriasis Severity Index (mNAPSI) score for the target-fingernail of ≥ 8, and either a BSA involvement of at least 10% or a BSA involvement of at least 5% with a total mNAPSI score for all fingernails of ≥ 20. Subjects received an initial dose of 80 mg HUMIRA followed by 40 mg every other week (starting one week after the initial dose) or placebo for 26 weeks followed by open-label HUMIRA treatment for an additional 26 weeks. This study evaluated the proportion of subjects who achieved “clear” or “minimal” assessment with at least a 2-grade improvement on the PGA-F scale and the proportion of subjects who achieved at least a 75% improvement from baseline in the mNAPSI score (mNAPSI 75) at Week 26.

At Week 26, a higher proportion of subjects in the HUMIRA group than in the placebo group achieved the PGA-F endpoint. Furthermore, a higher proportion of subjects in the HUMIRA group than in the placebo group achieved mNAPSI 75 at Week 26 (see Table 19).

Table 19. Efficacy Results at 26 Weeks
Endpoint | HUMIRA 40 mg every other week* N=109 | Placebo N=108
PGA-F: ≥2-grade improvement and clear or minimal | 49% | 7%
mNAPSI 75 | 47% | 3%
*Subjects received 80 mg of HUMIRA at Week 0, followed by 40 mg every other week starting at Week 1.

Nail pain was also evaluated and improvement in nail pain was observed in Study Ps-III.

14.10 Clinical Studies in Hidradenitis Suppurativa

Two randomized, double-blind, placebo-controlled studies (Studies HS-I and II) evaluated the safety and efficacy of HUMIRA in a total of 633 adult subjects with moderate to severe hidradenitis suppurativa (HS) with Hurley Stage II or III disease and with at least 3 abscesses or inflammatory nodules. In both studies, subjects received placebo or HUMIRA at an initial dose of 160 mg at Week 0, 80 mg at Week 2, and 40 mg every week starting at Week 4 and continued through Week 11. Subjects used topical antiseptic wash daily. Concomitant oral antibiotic use was allowed in Study HS-II.

Both studies evaluated Hidradenitis Suppurativa Clinical Response (HiSCR) at Week 12. HiSCR was defined as at least a 50% reduction in total abscess and inflammatory nodule count with no increase in abscess count and no increase in draining fistula count relative to baseline (see Table 18). Reduction in HS-related skin pain was assessed using a Numeric Rating Scale in subjects who entered the study with an initial baseline score of 3 or greater on a 11-point scale.

In both studies, a higher proportion of HUMIRA- than placebo-treated subjects achieved HiSCR (see Table 20).

Table 20. Efficacy Results at 12 Weeks in Subjects with Moderate to Severe Hidradenitis Suppurativa
 | HS Study I |  | HS Study II*
 | Placebo | Humira 40 mg Weekly | Placebo | Humira 40 mg Weekly
Hidradenitis Suppurativa Clinical Response (HiSCR) | N = 154 40 (26%) | N = 153 64 (42%) | N=163 45 (28%) | N=163 96 (59%)
*19.3% of subjects in Study HS-II continued baseline oral antibiotic therapy during the study.

In both studies, from Week 12 to Week 35 (Period B), subjects who had received HUMIRA were re-randomized to 1 of 3 treatment groups (HUMIRA 40 mg every week, HUMIRA 40 mg every other week, or placebo). Subjects who had been randomized to placebo were assigned to receive HUMIRA 40 mg every week (Study HS-I) or placebo (Study HS-II).

During Period B, flare of HS, defined as ≥25% increase from baseline in abscesses and inflammatory nodule counts and with a minimum of 2 additional lesions, was documented in 22 (22%) of the 100 subjects who were withdrawn from HUMIRA treatment following the primary efficacy timepoint in two studies.

14.11 Clinical Studies in Adults with Uveitis

The safety and efficacy of HUMIRA were assessed in adult subjects with non-infectious intermediate, posterior and panuveitis excluding subjects with isolated anterior uveitis, in two randomized, double-masked, placebo-controlled studies (UV I and II). Subjects received placebo or HUMIRA at an initial dose of 80 mg followed by 40 mg every other week starting one week after the initial dose. The primary efficacy endpoint in both studies was ´time to treatment failure´.

Treatment failure was a multi-component outcome defined as the development of new inflammatory chorioretinal and/or inflammatory retinal vascular lesions, an increase in anterior chamber (AC) cell grade or vitreous haze (VH) grade or a decrease in best corrected visual acuity (BCVA).

Study UV I evaluated 217 subjects with active uveitis while being treated with corticosteroids (oral prednisone at a dose of 10 to 60 mg/day). All subjects received a standardized dose of prednisone 60 mg/day at study entry followed by a mandatory taper schedule, with complete corticosteroid discontinuation by Week 15.

Study UV II evaluated 226 subjects with inactive uveitis while being treated with corticosteroids (oral prednisone 10 to 35 mg/day) at baseline to control their disease. Subjects subsequently underwent a mandatory taper schedule, with complete corticosteroid discontinuation by Week 19.

Clinical Response

Results from both studies demonstrated statistically significant reduction of the risk of treatment failure in subjects treated with HUMIRA versus subjects receiving placebo. In both studies, all components of the primary endpoint contributed cumulatively to the overall difference between HUMIRA and placebo groups (Table 21).

Table 21. Time to Treatment Failure in Studies UV I and UV II
 | UV I |  |  | UV II
 | Placebo (N = 107) | HUMIRA (N = 110) | HR [95% CI]a | Placebo (N = 111) | HUMIRA (N = 115) | HR [95% CI]a
Failureb n (%) | 84 (78.5) | 60 (54.5) | 0.50 [0.36, 0.70] | 61 (55.0) | 45 (39.1) | 0.57 [0.39, 0.84]
Median Time to Failure (Months) [95% CI] | 3.0 [2.7, 3.7] | 5.6 [3.9, 9.2] | N/A | 8.3 [4.8, 12.0] | NEc | N/A
ª HR of HUMIRA versus placebo from proportional hazards regression with treatment as factor.
b Treatment failure at or after Week 6 in Study UV I, or at or after Week 2 in Study UV II, was counted as event. Subjects who discontinued the study were censored at the time of dropping out.
c NE = not estimable. Fewer than half of at-risk subjects had an event.

Figure 3: Kaplan-Meier Curves Summarizing Time to Treatment Failure on or after Week 6 (Study UV I) or Week 2 (Study UV II)

Study UV I

Study UV II

Note: P# = Placebo (Number of Events/Number at Risk); A# = HUMIRA (Number of Events/Number at Risk).

14.12 Clinical Studies in Pediatric Subjects with Uveitis

The safety and efficacy of HUMIRA were assessed in a randomized, double-masked, placebo-controlled study of 90 pediatric subjects from 2 to < 18 years of age with active JIA-associated non-infectious uveitis (PUV-I). Subjects received either placebo or 20 mg adalimumab (if < 30 kg) or 40 mg adalimumab (if ≥ 30 kg) every other week in combination with a dose of methotrexate. Concomitant dosages of corticosteroids were permitted at study entry followed by a mandatory reduction in topical corticosteroids within 3 months.

The primary endpoint was ‘time to treatment failure’. The criteria determining treatment failure were worsening or sustained non-improvement in ocular inflammation, or worsening of ocular co-morbidities.

Clinical Response

HUMIRA significantly decreased the risk of treatment failure by 75% relative to placebo (HR = 0.25 [95% CI: 0.12, 0.49]) (Table 22).

Table 22. Analysis Results of Time to Treatment Failure (Study PUV-I)
 | Placebo (N=30) | HUMIRA (N=60) | HR (95% CI)ª
Failure (n[%]) | 18 (60%) | 16 (26.7%) | 0.25 (0.12, 0.49)
Median Time to Failure (Weeks) (95% CI)ᵇ | 24.1 (12.4, 81.0) | NEᶜ
a HR of adalimumab versus placebo from proportional hazards regression with treatment as factor.
b Estimated based on Kaplan-Meier curve.
c NE = not estimable. Fewer than half of at-risk subjects had an event.

Figure 4: Kaplan-Meier Curves Summarizing Time to Treatment Failure (Study PUV-I)

Study PUV-I
Note: P = Placebo (Number at Risk); H = HUMIRA (Number at Risk).

15 REFERENCES

1. National Cancer Institute. Surveillance, Epidemiology, and End Results Database (SEER) Program. SEER Incidence Crude Rates, 17 Registries, 2000-2007.

16 HOW SUPPLIED/STORAGE AND HANDLING

HUMIRA® (adalimumab) is supplied as a preservative-free, sterile, clear and colorless solution for subcutaneous administration. The following packaging configurations are available.

- HUMIRA Pen Carton - 40 mg/0.8 mL
  HUMIRA is supplied in a carton containing two alcohol preps and two dose trays. Each dose tray consists of a single-dose pen, containing a 1 mL prefilled glass syringe with a fixed ½ inch needle, providing 40 mg/0.8 mL of HUMIRA. The needle cover may contain natural rubber latex. The NDC number is 0074-4339-02.

- HUMIRA Pen Carton - 40 mg/0.4 mL
  HUMIRA is supplied in a carton containing two alcohol preps and two dose trays. Each dose tray consists of a single-dose pen, containing a 1 mL prefilled glass syringe with a fixed thin wall, ½ inch needle, providing 40 mg/0.4 mL of HUMIRA. The black needle cover is not made with natural rubber latex. The NDC number is 0074-0554-02.

- HUMIRA Pen Carton – 80 mg/0.8 mL
  HUMIRA is supplied in a carton containing two alcohol preps and two dose trays. Each dose tray consists of a single-dose pen, containing a 1 mL prefilled glass syringe with a fixed thin wall, ½ inch needle, providing 80 mg/0.8 mL of HUMIRA. The black needle cover is not made with natural rubber latex. The NDC number is 0074-0124-02.

- HUMIRA Pen 80 mg/0.8 mL - Starter Package for Crohn's Disease, Ulcerative Colitis or Hidradenitis Suppurativa
  HUMIRA is supplied in a carton containing 4 alcohol preps and 3 dose trays (Starter Package for Crohn’s Disease, Ulcerative Colitis or Hidradenitis Suppurativa). Each dose tray consists of a single-dose pen, containing a 1 mL prefilled glass syringe with a fixed thin wall, ½ inch needle, providing 80 mg/0.8 mL of HUMIRA. The black needle cover is not made with natural rubber latex. The NDC number is 0074-0124-03.

- HUMIRA Pen 80 mg/0.8 mL and 40 mg/0.4 mL - Psoriasis, Uveitis or Adolescent Hidradenitis Suppurativa Starter Package
  HUMIRA is supplied in a carton containing 4 alcohol preps and 3 dose trays (Psoriasis, Uveitis or Adolescent Hidradenitis Suppurativa Starter Package). One dose tray consists of a single-dose pen, containing a 1 mL prefilled glass syringe with a fixed thin wall, ½ inch needle, providing 80 mg/0.8 mL of HUMIRA. The other two dose trays each consist of a single-dose pen, containing a 1 mL prefilled glass syringe with a fixed thin wall, ½ inch needle, providing 40 mg/0.4 mL of HUMIRA. The black needle cover is not made with natural rubber latex. The NDC number is 0074-1539-03.

- HUMIRA Pen 80 mg/0.8 mL – Starter Package for Pediatric Ulcerative Colitis (4 count)
  HUMIRA is supplied in a carton containing 4 alcohol preps and 4 dose trays (Starter Package for Pediatric Ulcerative Colitis). Each dose tray consists of a single-dose pen, containing a 1 mL prefilled glass syringe with a fixed thin wall, ½ inch needle, providing 80 mg/0.8 mL of HUMIRA. The black needle cover is not made with natural rubber latex. The NDC number is 0074-0124-04.

- Prefilled Syringe Carton - 40 mg/0.8 mL
  HUMIRA is supplied in a carton containing two alcohol preps and two dose trays. Each dose tray consists of a single-dose, 1 mL prefilled glass syringe with a fixed ½ inch needle, providing 40 mg/0.8 mL of HUMIRA. The needle cover may contain natural rubber latex. The NDC number is 0074-3799-02.

- Prefilled Syringe Carton - 40 mg/0.4 mL
  HUMIRA is supplied in a carton containing two alcohol preps and two dose trays. Each dose tray consists of a single-dose, 1 mL prefilled glass syringe with a fixed thin wall, ½ inch needle, providing 40 mg/0.4 mL of HUMIRA. The black needle cover is not made with natural rubber latex. The NDC number is 0074-0243-02.

- Prefilled Syringe Carton - 20 mg/0.2 mL
  HUMIRA is supplied in a carton containing two alcohol preps and two dose trays. Each dose tray consists of a single-dose, 1 mL prefilled glass syringe with a fixed thin wall, ½ inch needle, providing 20 mg/0.2 mL of HUMIRA. The black needle cover is not made with natural rubber latex. The NDC number is 0074-0616-02.

- Prefilled Syringe Carton - 10 mg/0.1 mL
  HUMIRA is supplied in a carton containing two alcohol preps and two dose trays. Each dose tray consists of a single-dose, 1 mL prefilled glass syringe with a fixed thin wall, ½ inch needle, providing 10 mg/0.1 mL of HUMIRA. The black needle cover is not made with natural rubber latex. The NDC number is 0074-0817-02.

- HUMIRA Prefilled Syringe 80 mg/0.8 mL - Pediatric Crohn’s Disease Starter Package (3 count)
  HUMIRA is supplied in a carton containing 4 alcohol preps and 3 dose trays (Pediatric Starter Package). Each dose tray consists of a single-dose, 1 mL prefilled glass syringe with a fixed thin wall, ½ inch needle, providing 80 mg/0.8 mL of HUMIRA. The black needle cover is not made with natural rubber latex. The NDC number is 0074-2540-03.

- HUMIRA Prefilled Syringe 80 mg/0.8 mL and 40 mg/0.4 mL - Pediatric Crohn’s Disease Starter Package (2 count)
  HUMIRA is supplied in a carton containing 2 alcohol preps and 2 dose trays (Pediatric Starter Package). One dose tray consists of a single-dose, 1 mL prefilled glass syringe with a fixed thin wall, ½ inch needle, providing 80 mg/0.8 mL of HUMIRA. The other dose tray consists of a single-dose, 1 mL prefilled glass syringe with a fixed thin wall, ½ inch needle, providing 40 mg/0.4 mL of HUMIRA. The black needle cover is not made with natural rubber latex. The NDC number is 0074-0067-02.

Storage and Stability

Do not use beyond the expiration date on the container. HUMIRA must be refrigerated at 36°F to 46°F (2°C to 8°C). DO NOT FREEZE. Do not use if frozen even if it has been thawed.

Store in original carton until time of administration to protect from light.

If needed, for example when traveling, HUMIRA may be stored at room temperature up to a maximum of 77°F (25°C) for a period of up to 14 days, with protection from light. HUMIRA should be discarded if not used within the 14-day period. Record the date when HUMIRA is first removed from the refrigerator in the spaces provided on the carton and dose tray.

Do not store HUMIRA in extreme heat or cold.

17 PATIENT COUNSELING INFORMATION

Advise the patient or caregiver to read the FDA-approved patient labeling (Medication Guide and Instructions for Use).

Infections
Inform patients that HUMIRA may lower the ability of their immune system to fight infections. Instruct patients of the importance of contacting their doctor if they develop any symptoms of infection, including tuberculosis, invasive fungal infections, and reactivation of hepatitis B virus infections [see Warnings and Precautions (5.1, 5.2, 5.4)].

Malignancies
Counsel patients about the risk of malignancies while receiving HUMIRA [see Warnings and Precautions (5.2)]

Hypersensitivity Reactions
Advise patients to seek immediate medical attention if they experience any symptoms of severe hypersensitivity reactions. Advise latex-sensitive patients that the needle cap of the HUMIRA 40 mg/0.8 mL Pen and 40 mg/0.8 mL prefilled syringe may contain natural rubber latex [see Warnings and Precautions (5.3), How Supplied/Storage and Handling (16)].

Other Medical Conditions
Advise patients to report any signs of new or worsening medical conditions such as congestive heart failure, neurological disease, autoimmune disorders, or cytopenias. Advise patients to report any symptoms suggestive of a cytopenia such as bruising, bleeding, or persistent fever [see Warnings and Precautions (5.5, 5.6, 5.8, 5.9)].

Instructions on Injection Technique

Inform patients that the first injection is to be performed under the supervision of a qualified health care professional. If a patient or caregiver is to administer HUMIRA, instruct them in injection techniques and assess their ability to inject subcutaneously to ensure the proper administration of HUMIRA [see Instructions for Use].

For patients who will use the HUMIRA Pen, tell them that they:

- Will hear a loud ‘click’ when the plum-colored activator button is pressed. The loud click means the start of the injection.
- Must keep holding the HUMIRA Pen against their squeezed, raised skin until all of the medicine is injected. This can take up to 15 seconds.
- Will know that the injection has finished when the yellow marker fully appears in the window view and stops moving.

Instruct patients to dispose of their used needles and syringes or used Pen in a FDA-cleared sharps disposal container immediately after use. Instruct patients not to dispose of loose needles and syringes or Pen in their household trash. Instruct patients that if they do not have a FDA-cleared sharps disposal container, they may use a household container that is made of a heavy-duty plastic, can be closed with a tight-fitting and puncture-resistant lid without sharps being able to come out, upright and stable during use, leak-resistant, and properly labeled to warn of hazardous waste inside the container.

Instruct patients that when their sharps disposal container is almost full, they will need to follow their community guidelines for the correct way to dispose of their sharps disposal container. Instruct patients that there may be state or local laws regarding disposal of used needles and syringes. Refer patients to the FDA’s website at http://www.fda.gov/safesharpsdisposal for more information about safe sharps disposal, and for specific information about sharps disposal in the state that they live in.

Instruct patients not to dispose of their used sharps disposal container in their household trash unless their community guidelines permit this. Instruct patients not to recycle their used sharps disposal container.

AbbVie Inc.

North Chicago, IL 60064, U.S.A.

US License Number 1889

20098887 12/2025

MEDICATION GUIDE
HUMIRA® (Hu-MARE-ah)
(adalimumab)
injection, for subcutaneous use

Read the Medication Guide that comes with HUMIRA before you start taking it and each time you get a refill. There may be new information. This Medication Guide does not take the place of talking with your doctor about your medical condition or treatment.

What is the most important information I should know about HUMIRA?
HUMIRA is a medicine that affects your immune system. HUMIRA can lower the ability of your immune system to fight infections. Serious infections have happened in people taking HUMIRA. These serious infections include tuberculosis (TB) and infections caused by viruses, fungi or bacteria that have spread throughout the body. Some people have died from these infections.

- Your doctor should test you for TB before starting HUMIRA.
- Your doctor should check you closely for signs and symptoms of TB during treatment with HUMIRA.

You should not start taking HUMIRA if you have any kind of infection unless your doctor says it is okay.
Before starting HUMIRA, tell your doctor if you:

- think you have an infection or have symptoms of an infection such as:

- fever, sweats, or chills
- muscle aches
- cough
- shortness of breath
- blood in phlegm

- warm, red, or painful skin or sores on your body
- diarrhea or stomach pain
- burning when you urinate or urinate more often than normal
- feel very tired
- weight loss

- are being treated for an infection.
- get a lot of infections or have infections that keep coming back.
- have diabetes.
- have TB, or have been in close contact with someone with TB.
- were born in, lived in, or traveled to countries where there is more risk for getting TB. Ask your doctor if you are not sure.
- live or have lived in certain parts of the country (such as the Ohio and Mississippi River valleys) where there is an increased risk for getting certain kinds of fungal infections (histoplasmosis, coccidioidomycosis, or blastomycosis). These infections may happen or become more severe if you use HUMIRA. Ask your doctor if you do not know if you have lived in an area where these infections are common.
- have or have had hepatitis B.
- use the medicine ORENCIA (abatacept), KINERET (anakinra), RITUXAN (rituximab), IMURAN (azathioprine), or PURINETHOL (6–mercaptopurine, 6-MP).
- are scheduled to have major surgery.

After starting HUMIRA, call your doctor right away if you have an infection, or any sign of an infection.
HUMIRA can make you more likely to get infections or make any infection that you may have worse.

Cancer

- For children and adults taking Tumor Necrosis Factor (TNF)-blockers, including HUMIRA, the chances of getting cancer may increase.
- There have been cases of unusual cancers in children, teenagers, and young adults using TNF-blockers.
- People with rheumatoid arthritis (RA), especially more serious RA, may have a higher chance for getting a kind of cancer called lymphoma.
- If you use TNF blockers including HUMIRA your chance of getting two types of skin cancer may increase (basal cell cancer and squamous cell cancer of the skin). These types of cancer are generally not life-threatening if treated. Tell your doctor if you have a bump or open sore that does not heal.
- Some people receiving TNF blockers including HUMIRA developed a rare type of cancer called hepatosplenic T-cell lymphoma. This type of cancer often results in death. Most of these people were male teenagers or young men. Also, most people were being treated for Crohn’s disease or ulcerative colitis with another medicine called IMURAN (azathioprine) or PURINETHOL (6-mercaptopurine, 6–MP).

What is HUMIRA?
HUMIRA is a medicine called a Tumor Necrosis Factor (TNF) blocker. HUMIRA is used:

- To reduce the signs and symptoms of:
  ○ moderate to severe RA in adults. HUMIRA can be used alone, with methotrexate, or with certain other medicines.
  ○ moderate to severe polyarticular juvenile idiopathic arthritis (JIA) in children 2 years and older. HUMIRA can be used alone or with methotrexate.
  ○ psoriatic arthritis (PsA) in adults. HUMIRA can be used alone or with certain other medicines.
  ○ ankylosing spondylitis (AS) in adults.
  ○ moderate to severe hidradenitis suppurativa (HS) in people 12 years and older.
- To treat moderate to severe Crohn’s disease (CD) in adults and children 6 years of age and older.
- To treat moderate to severe ulcerative colitis (UC) in adults and children 5 years of age and older. It is not known if HUMIRA is effective in people who stopped responding to or could not tolerate TNF-blocker medicines.
- To treat moderate to severe chronic (lasting a long time) plaque psoriasis (Ps) in adults who have the condition in many areas of their body and who may benefit from taking injections or pills (systemic therapy) or phototherapy (treatment using ultraviolet light alone or with pills).
- To treat non-infectious intermediate, posterior, and panuveitis in adults and children 2 years of age and older.

What should I tell my doctor before taking HUMIRA?
HUMIRA may not be right for you. Before starting HUMIRA, tell your doctor about all of your medical conditions, including if you:

- have an infection. See “What is the most important information I should know about HUMIRA?”
- have or have had cancer.
- have any numbness or tingling or have a disease that affects your nervous system such as multiple sclerosis or Guillain-Barré syndrome.
- have or had heart failure.
- have recently received or are scheduled to receive a vaccine. You may receive vaccines, except for live vaccines while using HUMIRA. Children should be brought up to date with all vaccines before starting HUMIRA.
- are allergic to rubber or latex. Tell your doctor if you have any allergies to rubber or latex.
  ○ The needle cover for the HUMIRA Pen 40 mg/0.8 mL and HUMIRA 40 mg/0.8 mL prefilled syringe may contain natural rubber or latex.
  ○ The black needle cover for the HUMIRA Pen 80 mg/0.8 mL, HUMIRA 80 mg/0.8 mL prefilled syringe, HUMIRA Pen 40 mg/0.4 mL, HUMIRA 40 mg/0.4 mL prefilled syringe, HUMIRA 20 mg/0.2 mL prefilled syringe, and HUMIRA 10 mg/0.1 mL prefilled syringe are not made with natural rubber or latex.
- are allergic to HUMIRA or to any of its ingredients. See the end of this Medication Guide for a list of ingredients in HUMIRA.
- are pregnant or plan to become pregnant, breastfeeding or plan to breastfeed. You and your doctor should decide if you should take HUMIRA while you are pregnant or breastfeeding.
- have a baby and you were using HUMIRA during your pregnancy. Tell your baby’s doctor before your baby receives any vaccines.

Tell your doctor about all the medicines you take, including prescription and over-the-counter medicines, vitamins, and herbal supplements.
Especially tell your doctor if you use:

- ORENCIA (abatacept), KINERET (anakinra), REMICADE (infliximab), ENBREL (etanercept), CIMZIA (certolizumab pegol) or SIMPONI (golimumab), because you should not use HUMIRA while you are also using one of these medicines.
- RITUXAN (rituximab). Your doctor may not want to give you HUMIRA if you have received RITUXAN (rituximab) recently.
- IMURAN (azathioprine) or PURINETHOL (6–mercaptopurine, 6-MP).

Keep a list of your medicines with you to show your doctor and pharmacist each time you get a new medicine.

How should I take HUMIRA?

- HUMIRA is given by an injection under the skin. Your doctor will tell you how often to take an injection of HUMIRA. This is based on your condition to be treated. Do not inject HUMIRA more often than you were prescribed.
- See the Instructions for Use inside the carton for complete instructions for the right way to prepare and inject HUMIRA.
- Make sure you have been shown how to inject HUMIRA before you do it yourself. You can call your doctor or 1-800-4HUMIRA (1-800-448-6472) if you have any questions about giving yourself an injection. Someone you know can also help you with your injection after they have been shown how to prepare and inject HUMIRA.
- Do not try to inject HUMIRA yourself until you have been shown the right way to give the injections. If your doctor decides that you or a caregiver may be able to give your injections of HUMIRA at home, you should receive training on the right way to prepare and inject HUMIRA.
- Do not miss any doses of HUMIRA unless your doctor says it is okay. If you forget to take HUMIRA, inject a dose as soon as you remember. Then, take your next dose at your regular scheduled time. This will put you back on schedule. In case you are not sure when to inject HUMIRA, call your doctor or pharmacist.
- If you take more HUMIRA than you were told to take, call your doctor.

What are the possible side effects of HUMIRA?
HUMIRA can cause serious side effects, including:
See “What is the most important information I should know about HUMIRA?”

- Serious Infections.
  Your doctor will examine you for TB and perform a test to see if you have TB. If your doctor feels that you are at risk for TB, you may be treated with medicine for TB before you begin treatment with HUMIRA and during treatment with HUMIRA. Even if your TB test is negative your doctor should carefully monitor you for TB infections while you are taking HUMIRA. People who had a negative TB skin test before receiving HUMIRA have developed active TB. Tell your doctor if you have any of the following symptoms while taking or after taking HUMIRA:

- cough that does not go away
- low grade fever

- weight loss
- loss of body fat and muscle (wasting)

- Hepatitis B infection in people who carry the virus in their blood.
  If you are a carrier of the hepatitis B virus (a virus that affects the liver), the virus can become active while you use HUMIRA. Your doctor should do blood tests before you start treatment, while you are using HUMIRA, and for several months after you stop treatment with HUMIRA. Tell your doctor if you have any of the following symptoms of a possible hepatitis B infection:

- muscle aches
- feel very tired
- dark urine
- skin or eyes look yellow
- little or no appetite
- vomiting

- clay-colored bowel movements
- fever
- chills
- stomach discomfort
- skin rash

- Allergic reactions. Allergic reactions can happen in people who use HUMIRA. Call your doctor or get medical help right away if you have any of these symptoms of a serious allergic reaction:

- hives
- trouble breathing

- swelling of your face, eyes, lips or mouth

- Nervous system problems. Signs and symptoms of a nervous system problem include: numbness or tingling, problems with your vision, weakness in your arms or legs, and dizziness.
- Blood problems. Your body may not make enough of the blood cells that help fight infections or help to stop bleeding. Symptoms include a fever that does not go away, bruising or bleeding very easily, or looking very pale.
- New heart failure or worsening of heart failure you already have. Call your doctor right away if you get new worsening symptoms of heart failure while taking HUMIRA, including:

- shortness of breath
- sudden weight gain

- swelling of your ankles or feet

- Immune reactions including a lupus-like syndrome. Symptoms include chest discomfort or pain that does not go away, shortness of breath, joint pain, or a rash on your cheeks or arms that gets worse in the sun. Symptoms may improve when you stop HUMIRA.
- Liver problems. Liver problems can happen in people who use TNF-blocker medicines. These problems can lead to liver failure and death. Call your doctor right away if you have any of these symptoms:

- feel very tired
- poor appetite or vomiting

- skin or eyes look yellow
- pain on the right side of your stomach (abdomen)

- Psoriasis. Some people using HUMIRA had new psoriasis or worsening of psoriasis they already had. Tell your doctor if you develop red scaly patches or raised bumps that are filled with pus. Your doctor may decide to stop your treatment with HUMIRA.

Call your doctor or get medical care right away if you develop any of the above symptoms. Your treatment with HUMIRA may be stopped.
The most common side effects of HUMIRA include:

- injection site reactions: redness, rash, swelling, itching, or bruising. These symptoms usually will go away within a few days. Call your doctor right away if you have pain, redness or swelling around the injection site that does not go away within a few days or gets worse.
- upper respiratory infections (including sinus infections).
- headaches.
- rash.

These are not all the possible side effects with HUMIRA. Tell your doctor if you have any side effect that bothers you or that does not go away. Ask your doctor or pharmacist for more information.
Call your doctor for medical advice about side effects. You may report side effects to FDA at 1-800-FDA-1088.

How should I store HUMIRA?

- Store HUMIRA in the refrigerator at 36ºF to 46ºF (2ºC to 8ºC). Store HUMIRA in the original carton until use to protect it from light.
- Do not freeze HUMIRA. Do not use HUMIRA if frozen, even if it has been thawed.
- Refrigerated HUMIRA may be used until the expiration date printed on the HUMIRA carton, dose tray, Pen or prefilled syringe. Do not use HUMIRA after the expiration date.
- If needed, for example when you are traveling, you may also store HUMIRA at room temperature up to 77°F (25°C) for up to 14 days. Store HUMIRA in the original carton until use to protect it from light.
- Throw away HUMIRA if it has been kept at room temperature and not been used within 14 days.
- Record the date you first remove HUMIRA from the refrigerator in the spaces provided on the carton and dose tray.
- Do not store HUMIRA in extreme heat or cold.
- Do not use a Pen or prefilled syringe if the liquid is cloudy, discolored, or has flakes or particles in it.
- Do not drop or crush HUMIRA. The prefilled syringe is glass.

Keep HUMIRA, injection supplies, and all other medicines out of the reach of children.

General information about the safe and effective use of HUMIRA.
Medicines are sometimes prescribed for purposes other than those listed in a Medication Guide. Do not use HUMIRA for a condition for which it was not prescribed. Do not give HUMIRA to other people, even if they have the same condition. It may harm them.
This Medication Guide summarizes the most important information about HUMIRA. If you would like more information, talk with your doctor. You can ask your pharmacist or doctor for information about HUMIRA that is written for health professionals.

What are the ingredients in HUMIRA?
Active ingredient: adalimumab
HUMIRA Pen 40 mg/0.8 mL, HUMIRA 40 mg/0.8 mL prefilled syringe:
Inactive ingredients: citric acid monohydrate, dibasic sodium phosphate dihydrate, mannitol, monobasic sodium phosphate dihydrate, polysorbate 80, sodium chloride, sodium citrate and Water for Injection. Sodium hydroxide is added as necessary to adjust pH.
HUMIRA Pen 80 mg/0.8 mL, HUMIRA 80 mg/0.8 mL prefilled syringe, HUMIRA Pen 40 mg/0.4 mL, HUMIRA 40 mg/0.4 mL prefilled syringe, HUMIRA 20 mg/0.2 mL prefilled syringe and HUMIRA 10 mg/0.1 mL prefilled syringe:
Inactive ingredients: mannitol, polysorbate 80, and Water for Injection.
Manufactured by: AbbVie Inc., North Chicago, IL 60064, U.S.A.
For more information go to www.HUMIRA.com or you can enroll in a patient support program by calling 1-800-4HUMIRA (1-800-448-6472).
US License Number 1889

This Medication Guide has been approved by the U.S. Food and Drug Administration.
20098888

Revised: 12/2025

INSTRUCTIONS FOR USE
HUMIRA® [Hu-MARE-ah]
(adalimumab)
Injection, for subcutaneous use
40 mg/0.8 mL
Single-Dose Pen
This Instructions for Use contains information on how to inject HUMIRA.

Before Injecting: Your healthcare provider should show you how to use HUMIRA before you use it for the first time. Call your healthcare provider or 1-800-4HUMIRA (1-800-448-6472) if you need help.

Important Information You Need to Know Before Injecting HUMIRA

Do not use the Pen and call your healthcare provider or pharmacist if:

- Liquid is cloudy, discolored, or has flakes or particles in it
- Expiration date has passed

- Liquid has been frozen (even if thawed) or left in direct sunlight
- The seals of the carton are broken or missing or if the Pen has been dropped or crushed

Keep the caps on until right before your injection.
How should I store HUMIRA?

- Store HUMIRA in the refrigerator between 36°F to 46°F (2°C to 8°C).
- Store HUMIRA in the original carton until use to protect it from light.
- Do not freeze
- Refrigerated HUMIRA may be used until the expiration date printed on the HUMIRA carton, dose tray or Pen
- If needed, for example when you are traveling, you may also store HUMIRA at room temperature up to 77°F (25°C) for up to 14 days.

- Throw away HUMIRA if it has been kept at room temperature and not used within 14 days.
- Record the date you first remove HUMIRA from the refrigerator in the spaces provided on the carton and dose tray.
- Do not store HUMIRA in extreme heat or cold.

Keep HUMIRA, injection supplies, and all other medicines out of the reach of children.
Read Instructions on All Pages Before Using the HUMIRA Pen

Take HUMIRA out of the refrigerator.
Leave HUMIRA at room temperature for 15 to 30 minutes before injecting.

- Do not remove the Gray Cap #1 or Plum-colored Cap #2 while allowing HUMIRA to reach room temperature
- Do not warm HUMIRA in any other way. For example, do not warm it in a microwave or in hot water.
- Do not use the Pen if liquid has been frozen (even if thawed)

Check expiration date on the Pen label. Do not use the Pen if expiration date has passed.
Place the following on a clean, flat surface:

- 1 single-dose Pen and alcohol swab
- 1 cotton ball or gauze pad (not included)
- Puncture-resistant sharps disposal container (not included). See Step 9 at the end of this Instructions for Use for instructions on how to throw away (dispose of) your HUMIRA Pen.

Wash and dry your hands.

Choose an injection site:

- On the front of your thighs or
- Your lower abdomen (belly) at least 2 inches from your navel (belly button)
- Different from your last injection site

Wipe the injection site in a circular motion with the alcohol swab and let it dry.

- Do not touch or blow on the injection site after it is cleaned. Allow the skin to dry before injecting.
- Do not inject through clothes
- Do not inject into skin that is sore, bruised, red, hard, scarred, has stretch marks, or areas with psoriasis plaques

Hold the Pen with the Gray Cap #1 facing up. Check the inspection window.

- It is normal to see 1 or more bubbles in the inspection window.
- Make sure the liquid is clear and colorless
- Do not use the Pen if the liquid is cloudy, discolored, or has flakes or particles in it
- Do not use the Pen if it has been dropped or crushed.

Pull the Gray Cap #1 straight off.
Do not twist the cap.
Throw the cap away.
Do not put the Gray Cap #1 back on the Pen. Putting the Gray Cap #1 back on may damage the needle.

- Make sure the small needle cover of the Pen has come off with the Gray Cap #1.
- It is normal to see a few drops of liquid come out of the needle.

Pull the Plum-colored Cap #2 straight off.
Throw the cap away.
Turn the Pen so that the gray arrow points toward the injection site.
Do not press the plum activator button until you are ready to inject.

Squeeze the skin at your injection site to make a raised area and hold it firmly until the injection is complete.
Point the gray arrow toward the injection site.
Place the white needle sleeve straight (90- degree angle) against the injection site.
Hold the Pen so that you can see the inspection window.
Do not press the plum activator button until you are ready to inject.

It is important that you firmly push the Pen down all the way against the injection site before starting the injection.
Keep pushing down to prevent the Pen from moving away from the skin during the injection.
Press the plum activator button and count slowly for 15 seconds.

- A loud click will signal the start of the injection.
- Do not be startled by this click.
- Keep pushing the Pen down firmly against the injection site until the injection is complete
- Injection is complete when the yellow indicator has stopped moving.

When the injection is completed, slowly pull the Pen from the skin. The white needle sleeve will cover the needle tip.

- A small amount of liquid on the injection site is normal.

If there are more than a few drops of liquid on the injection site, call 1-800-4HUMIRA (1-800-448-6472) for help.
After completing the injection, place a cotton ball or gauze pad on the skin of the injection site.

- Do not rub.
- Slight bleeding at the injection site is normal

How should I throw away (dispose of) the used HUMIRA Pen?

- Put your used needles and, Pens in a FDA- cleared sharps disposal container right away after use. Do not throw away (dispose of) loose needles, syringes, and the Pen in the household trash.
- If you do not have a FDA-cleared sharps disposal container, you may use a household container that is:
  - made of a heavy-duty plastic,
  - can be closed with a tight-fitting, puncture-resistant lid, without sharps being able to come out,
  - upright and stable during use,
  - leak-resistant, and
  - properly labeled to warn of hazardous waste inside the container.
- When your sharps disposal container is almost full, you will need to follow your community guidelines for the right way to dispose of your sharps disposal container. There may be state or local laws about how you should throw away used needles and syringes. For more information about safe sharps disposal, and for specific information about sharps disposal in the state that you live in, go to the FDA’s website at: http://www.fda.gov/safesharpsdisposal.
- Do not dispose of your used sharps disposal container in your household trash unless your community guidelines permit this. Do not recycle your used sharps disposal container.

The Pen caps, alcohol swab, cotton ball or gauze pad, dose tray, and packaging may be placed in your household trash.

Questions About Using the HUMIRA Pen
What if I have not received in person training from a healthcare provider?

- Call your healthcare provider or 1-800-4HUMIRA (1-800-448-6472) or visit www.HUMIRA.com if you need help

How do I know when the injection is complete?

- The yellow indicator has stopped moving. This takes up to 15 seconds.

What should I do if there are more than a few drops of liquid on the injection site?

- Call 1-800-4HUMIRA (1-800-448-6472) for help

Always keep the Pen and the sharps disposal container out of reach of children.

Keep a record of the dates and locations of your injections. To help remember when to take HUMIRA, mark your calendar ahead of time.

This Instructions for Use has been approved by the U.S. Food and Drug Administration.

Revised 12/2025

Manufactured by AbbVie Inc. North Chicago, IL 60064 U.S.A.
US License Number 1889 20098761

INSTRUCTIONS FOR USE
HUMIRA® [Hu-MARE-ah]
(adalimumab)
injection, for subcutaneous use
40 mg/0.4 mL
Single-Dose Pen

This Instructions for Use contains information on how to inject HUMIRA.
Before Injecting: Your healthcare provider should show you how to use HUMIRA before you use it for the first time. Call your healthcare provider or 1-800-4HUMIRA (1-800-448-6472) if you need help.

Important Information You Need to Know Before Injecting HUMIRA

Do not use the Pen and call your healthcare provider or pharmacist if:

- Liquid is cloudy, discolored, or has flakes or particles in it
- Expiration date has passed

- Liquid has been frozen (even if thawed) or left in direct sunlight
- The seals of the carton are broken or missing or if the Pen has been dropped or crushed

Keep the caps on until right before your injection.
How should I store HUMIRA?

- Store HUMIRA in the refrigerator between 36°F to 46°F (2°C to 8°C).
- Store HUMIRA in the original carton until use to protect it from light.
- Do not freeze
- Refrigerated HUMIRA may be used until the expiration date printed on the HUMIRA carton, dose tray or Pen.
- If needed, for example when you are traveling, you may also store HUMIRA at room temperature up to 77°F (25°C) for up to 14 days.

- Throw away HUMIRA if it has been kept at room temperature and not used within 14 days.
- Record the date you first remove HUMIRA from the refrigerator in the spaces provided on the carton and dose tray.
- Do not store HUMIRA in extreme heat or cold.

Keep HUMIRA, injection supplies, and all other medicines out of the reach of children.
Read Instructions on All Pages Before Using the HUMIRA Pen

Take HUMIRA out of the refrigerator.
Leave HUMIRA at room temperature for 15 to 30 minutes before injecting.

- Do not remove the Gray Cap #1 or Plum-colored Cap #2 while allowing HUMIRA to reach room temperature.
- Do not warm HUMIRA in any other way. For example, do not warm it in a microwave or in hot water.
- Do not use the Pen if liquid has been frozen (even if thawed).

Check expiration date on the Pen label. Do not use the Pen if expiration date has passed.
Place the following on a clean, flat surface:

- 1 single-dose Pen and alcohol swab
- 1 cotton ball or gauze pad (not included)
- Puncture-resistant sharps disposal container (not included). See Step 9 at the end of this Instructions for Use for instructions on how to throw away (dispose of) your HUMIRA Pen.

Wash and dry your hands.

Choose an injection site:

- On the front of your thighs or
- Your lower abdomen (belly) at least 2 inches from your navel (belly button)
- Different from your last injection site

Wipe the injection site in a circular motion with the alcohol swab and let it dry.

- Do not touch or blow on the injection site after it is cleaned. Allow the skin to dry before injecting.
- Do not inject through clothes
- Do not inject into skin that is sore, bruised, red, hard, scarred, has stretch marks, or areas with psoriasis plaques

Hold the Pen with the Gray Cap #1 facing up. Check the inspection window.

- It is normal to see 1 or more bubbles in the inspection window.
- Make sure the liquid is clear and colorless.
- Do not use the Pen if the liquid is cloudy, discolored, or has flakes or particles in it.
- Do not use the Pen if it has been dropped or crushed.

Pull the Gray Cap #1 straight off.
Throw the cap away.

- It is normal to see a few drops of liquid come out of the needle.

Pull the Plum-colored Cap #2 straight off.
Throw the cap away.
Turn the Pen so that the white arrow points toward the injection site.
Do not press the plum activator button until you are ready to inject.

Squeeze the skin at your injection site to make a raised area and hold it firmly until the injection is complete.
Point the white arrow toward the injection site.
Place the white needle sleeve straight (90-degree angle) against the injection site.
Hold the Pen so that you can see the inspection window.
Do not press the plum activator button until you are ready to inject.

It is important that you firmly push the Pen down all the way against the injection site before starting the injection.
Keep pushing down to prevent the Pen from moving away from the skin during the injection.
Press the plum activator button and count slowly for 15 seconds.

- A loud click will signal the start of the injection.
- Do not be startled by this click.
- Keep pushing the Pen down firmly against the injection site until the injection is complete.
- Injection is complete when the yellow indicator has stopped moving.

When the injection is completed, slowly pull the Pen from the skin. The white needle sleeve will cover the needle tip.

- A small amount of liquid on the injection site is normal.

If there are more than a few drops of liquid on the injection site, call 1-800-4HUMIRA (1-800-448-6472) for help.
After completing the injection, place a cotton ball or gauze pad on the skin of the injection site.

- Do not rub.
- Slight bleeding at the injection site is normal.

How should I throw away (dispose of) the used HUMIRA Pen?

- Put your used needles, and Pens in a FDA-cleared sharps disposal container right away after use. Do not throw away (dispose of) loose needles, syringes, and the Pen in the household trash.
- If you do not have a FDA-cleared sharps disposal container, you may use a household container that is:
  ○ made of a heavy-duty plastic,
  ○ can be closed with a tight-fitting, puncture-resistant lid, without sharps being able to come out,
  ○ upright and stable during use,
  ○ leak-resistant, and
  ○ properly labeled to warn of hazardous waste inside the container.
- When your sharps disposal container is almost full, you will need to follow your community guidelines for the right way to dispose of your sharps disposal container. There may be state or local laws about how you should throw away used needles and syringes. For more information about safe sharps disposal, and for specific information about sharps disposal in the state that you live in, go to the FDA’s website at: http://www.fda.gov/safesharpsdisposal.
- Do not dispose of your used sharps disposal container in your household trash unless your community guidelines permit this. Do not recycle your used sharps disposal container.

The Pen caps, alcohol swab, cotton ball or gauze pad, dose tray, and packaging may be placed in your household trash.

Questions About Using the HUMIRA Pen
What if I have not received in person training from a healthcare provider?

- Call your healthcare provider or 1-800-4HUMIRA (1-800-448-6472) or visit www.HUMIRA.com if you need help.

How do I know when the injection is complete?

- The yellow indicator has stopped moving. This takes up to 15 seconds.

What should I do if there are more than a few drops of liquid on the injection site?

- Call 1-800-4HUMIRA (1-800-448-6472) for help.

Always keep the Pen and the sharps disposal container out of reach of children.

Keep a record of the dates and locations of your injections. To help remember when to take HUMIRA, mark your calendar ahead of time.

This Instructions for Use has been approved by the U.S. Food and Drug Administration.

Revised 12/2025

Manufactured by AbbVie Inc. North Chicago, IL 60064 U.S.A.
US License Number 1889 20098762

INSTRUCTIONS FOR USE

HUMIRA® [Hu-MARE-ah]
(adalimumab)
injection, for subcutaneous use
80 mg/0.8 mL
Single-Dose Pen

This Instructions for Use contains information on how to inject HUMIRA.
Before Injecting: Your healthcare provider should show you how to use HUMIRA before you use it for the first time. Call your healthcare provider or 1-800-4HUMIRA (1-800-448-6472) if you need help.

Important Information You Need to Know Before Injecting HUMIRA

Do not use the Pen and call your healthcare provider or pharmacist if:

- Liquid is cloudy, discolored, or has flakes or particles in it
- Expiration date has passed

- Liquid has been frozen (even if thawed) or left in direct sunlight
- The seals of the carton are broken or missing or if the Pen has been dropped or crushed

Keep the caps on until right before your injection.
How should I store HUMIRA?

- Store HUMIRA in the refrigerator between 36°F to 46°F (2°C to 8°C).
- Store HUMIRA in the original carton until use to protect it from light.
- Do not freeze.
- Refrigerated HUMIRA may be used until the expiration date printed on the HUMIRA carton, dose tray or Pen.
- If needed, for example when you are traveling, you may also store HUMIRA at room temperature up to 77°F (25°C) for up to 14 days.

- Throw away HUMIRA if it has been kept at room temperature and not used within 14 days.
- Record the date you first remove HUMIRA from the refrigerator in the spaces provided on the carton and dose tray.
- Do not store HUMIRA in extreme heat or cold.

Keep HUMIRA, injection supplies, and all other medicines out of the reach of children.
Read Instructions on All Pages Before Using the HUMIRA Pen

Take HUMIRA out of the refrigerator.
Leave HUMIRA at room temperature for 15 to 30 minutes before injecting.

- Do not remove the Gray Cap #1 or Plum-colored Cap #2 while allowing HUMIRA to reach room temperature.
- Do not warm HUMIRA in any other way. For example, do not warm it in a microwave or in hot water.
- Do not use the Pen if liquid has been frozen (even if thawed).

Check expiration date on the Pen label. Do not use the Pen if expiration date has passed.
Place the following on a clean, flat surface:

- 1 single-dose Pen and alcohol swab
- 1 cotton ball or gauze pad (not included)
- Puncture-resistant sharps disposal container (not included). See Step 9 at the end of this Instructions for Use for instructions on how to throw away (dispose of) your HUMIRA Pen

Wash and dry your hands.

Choose an injection site:

- On the front of your thighs or
- Your lower abdomen (belly) at least 2 inches from your navel (belly button)
- Different from your last injection site

Wipe the injection site in a circular motion with the alcohol swab and let it dry.

- Do not touch or blow on the injection site after it is cleaned. Allow the skin to dry before injecting.
- Do not inject through clothes
- Do not inject into skin that is sore, bruised, red, hard, scarred, has stretch marks, or areas with psoriasis plaques

Hold the Pen with the Gray Cap #1 facing up. Check the inspection window.

- It is normal to see 1 or more bubbles in the inspection window.
- Make sure the liquid is clear and colorless.
- Do not use the Pen if the liquid is cloudy, discolored, or has flakes or particles in it.
- Do not use the Pen if it has been dropped or crushed.

Pull the Gray Cap #1 straight off.
Throw the cap away.

- It is normal to see a few drops of liquid come out of the needle

Pull the Plum-colored Cap #2 straight off.
Throw the cap away.
Turn the Pen so that the white arrow points toward the injection site.
Do not press the plum activator button until you are ready to inject.

Squeeze the skin at your injection site to make a raised area and hold it firmly until the injection is complete.
Point the white arrow toward the injection site.
Place the white needle sleeve straight (90-degree angle) against the injection site.
Hold the Pen so that you can see the inspection window.
Do not press the plum activator button until you are ready to inject.

It is important that you firmly push the Pen down all the way against the injection site before starting the injection.
Press the plum activator button and count slowly for 15 seconds.

- A loud click will signal the start of the injection.
- Do not be startled by this click.
- Keep pushing the Pen down firmly against the injection site until the injection is complete.
- Injection is complete when the yellow indicator has stopped moving.

When the injection is completed, slowly pull the Pen from the skin. The white needle sleeve will cover the needle tip.

- A small amount of liquid on the injection site is normal.

If there are more than a few drops of liquid on the injection site, call 1-800-4HUMIRA (1-800-448-6472) for help.
After completing the injection, place a cotton ball or gauze pad on the skin of the injection site.

- Do not rub.
- Slight bleeding at the injection site is normal.

How should I throw away (dispose of) the used HUMIRA Pen?

- Put your used needles and Pens in a FDA-cleared sharps disposal container right away after use. Do not throw away (dispose of) loose needles, syringes, and the Pen in the household trash.
- If you do not have a FDA-cleared sharps disposal container, you may use a household container that is:
  ○ made of a heavy-duty plastic,
  ○ can be closed with a tight-fitting, puncture-resistant lid, without sharps being able to come out,
  ○ upright and stable during use,
  ○ leak-resistant, and
  ○ properly labeled to warn of hazardous waste inside the container.
- When your sharps disposal container is almost full, you will need to follow your community guidelines for the right way to dispose of your sharps disposal container. There may be state or local laws about how you should throw away used needles and syringes. For more information about safe sharps disposal, and for specific information about sharps disposal in the state that you live in, go to the FDA’s website at: http://www.fda.gov/safesharpsdisposal.
- Do not dispose of your used sharps disposal container in your household trash unless your community guidelines permit this. Do not recycle your used sharps disposal container.

The Pen caps, alcohol swab, cotton ball or gauze pad, dose tray, and packaging may be placed in your household trash.

Questions About Using the HUMIRA Pen
What if I have not received in-person training from a healthcare provider?

- Call your healthcare provider or 1-800-4HUMIRA (1-800-448-6472) or visit www.HUMIRA.com if you need help.

How do I know when the injection is complete?

- The yellow indicator has stopped moving. This takes up to 15 seconds.

What should I do if there are more than a few drops of liquid on the injection site?

- Call 1-800-4HUMIRA (1-800-448-6472) for help.

Always keep the Pen and the sharps disposal container out of reach of children.

Keep a record of the dates and locations of your injections. To help remember when to take HUMIRA, mark your calendar ahead of time.

This Instructions for Use has been approved by the U.S. Food and Drug Administration.

Revised 12/2025

Manufactured by AbbVie Inc. North Chicago, IL 60064 U.S.A.
US License Number 1889 20098763

INSTRUCTIONS FOR USE

HUMIRA® [Hu-MARE-ah]
(adalimumab)
injection, for subcutaneous use
40 mg/0.8 mL
Single-Dose Prefilled Syringe
This Instructions for Use contains information on how to inject HUMIRA.

Before Injecting: Your healthcare provider should show you how to use HUMIRA before you use it for the first time. Call your healthcare provider or 1-800-4HUMIRA (1-800-448-6472) if you need help.

Important Information You Need to Know Before Injecting HUMIRA

Do not use the prefilled syringe and call your healthcare provider or pharmacist if:

- Liquid is cloudy, discolored, or has flakes or particles in it
- Expiration date has passed

- Liquid has been frozen (even if thawed) or left in direct sunlight
- The seals of the carton are broken or missing or if the prefilled syringe has been dropped or crushed

Keep the needle cover on until right before your injection.
How should I store HUMIRA?

- Store HUMIRA in the refrigerator between 36°F to 46°F (2°C to 8°C).
- Store HUMIRA in the original carton until use to protect it from light.
- Do not freeze.
- Refrigerated HUMIRA may be used until the expiration date printed on the HUMIRA carton, dose tray or prefilled syringe.
- If needed, for example when you are traveling, you may also store HUMIRA at room temperature up to 77°F (25°C) for up to 14 days.

- Throw away HUMIRA if it has been kept at room temperature and not used within 14 days.
- Record the date you first remove HUMIRA from the refrigerator in the spaces provided on the carton and dose tray.
- Do not store HUMIRA in extreme heat or cold.

Keep HUMIRA, injection supplies, and all other medicines out of the reach of children.
Read Instructions on All Pages Before Using the HUMIRA Single-Dose Prefilled Syringe

Take HUMIRA out of the refrigerator.
Leave HUMIRA at room temperature for 15 to 30 minutes before injecting.

- Do not remove the needle cover while allowing HUMIRA to reach room temperature.
- Do not warm HUMIRA in any other way. For example, do not warm it in a microwave or in hot water.
- Do not use the prefilled syringe if liquid has been frozen (even if thawed).

Check expiration date on the prefilled syringe label. Do not use the prefilled syringe if expiration date has passed.
Place the following on a clean, flat surface:

- 1 single-dose prefilled syringe and alcohol swab
- 1 cotton ball or gauze pad (not included)
- Puncture-resistant sharps disposal container (not included). See Step 9 at the end of this Instructions for Use for instructions on how to throw away (dispose of) your prefilled syringe.

Wash and dry your hands.

Choose an injection site:

- On the front of your thighs or
- Your lower abdomen (belly) at least 2 inches from your navel (belly button)
- Different from your last injection site

Wipe the injection site in a circular motion with the alcohol swab and let it dry.

- Do not touch or blow on the injection site after it is cleaned. Allow the skin to dry before injecting.
- Do not inject through clothes.
- Do not inject into skin that is sore, bruised, red, hard, scarred, has stretch marks, or areas with psoriasis plaques.

Hold the prefilled syringe in one hand.
Gently pull the needle cover straight off with the other hand.

- Throw the needle cover away.
- Do not touch the needle with your fingers or let the needle touch anything.

Hold the prefilled syringe with the needle facing up.

- Hold the prefilled syringe at eye level with one hand so you can see the air in the prefilled syringe.
- Using your other hand, slowly push the plunger in to push the air out through the needle.
- You may see a drop of liquid at the end of the needle. This is normal.

Hold the body of the prefilled syringe in one hand between the thumb and pointer (index) fingers. Hold the prefilled syringe in your hand like a pencil.
Do not pull back on the plunger at any time.

Gently squeeze the area of cleaned skin at your injection site with your other hand. Hold the skin firmly.
Insert the needle into the skin at about a 45-degree angle using a quick, dart-like motion.

- After the needle is in, let go of the skin.

Slowly push the plunger all the way in until all of the liquid is injected and the prefilled syringe is empty.

When the injection is completed, slowly pull the needle out of the skin while keeping the prefilled syringe at the same angle.
After completing the injection, place a cotton ball or gauze pad on the skin of the injection site.

- Do not rub
- Slight bleeding at the injection site is normal

How should I throw way (dispose of) the used HUMIRA prefilled syringe?

- Put your used needles and syringes in a FDA-cleared sharps disposal container right away after use. Do not throw away (dispose of) loose needles and syringes in the household trash.
- If you do not have a FDA-cleared sharps disposal container, you may use a household container that is:
  - made of a heavy-duty plastic,
  - can be closed with a tight-fitting, puncture-resistant lid, without sharps being able to come out,
  - upright and stable during use,
  - leak-resistant, and
  - properly labeled to warn of hazardous waste inside the container.
- When your sharps disposal container is almost full, you will need to follow your community guidelines for the right way to dispose of your sharps disposal container. There may be state or local laws about how you should throw away used needles and syringes. For more information about safe sharps disposal, and for specific information about sharps disposal in the state that you live in, go to the FDA’s website at: http://www.fda.gov/safesharpsdisposal.
- Do not dispose of your used sharps disposal container in your household trash unless your community guidelines permit this. Do not recycle your used sharps disposal container.
- For the safety and health of you and others, needles and used syringes must never be re-used.

The needle cover, alcohol swab, cotton ball or gauze pad, dose tray, and packaging may be placed in your household trash.

Questions About Using the HUMIRA Single-Dose Prefilled Syringe
What if I have not received in-person training from a healthcare provider?

- Call your healthcare provider or 1-800-4HUMIRA (1-800-448-6472) or visit www.HUMIRA.com if you need help

Always keep the prefilled syringe and the sharps disposal container out of the reach of children.

Keep a record of the dates and locations of your injections. To help remember when to take HUMIRA, mark your calendar ahead of time.

This Instructions for Use has been approved by the U.S. Food and Drug Administration.

Revised 12/2025

Manufactured by AbbVie Inc. North Chicago, IL 60064 U.S.A.
US License Number 1889 20098765

INSTRUCTIONS FOR USE

HUMIRA® [Hu-MARE-ah]
(adalimumab)
injection, for subcutaneous use
80 mg/0.8 mL, 40 mg/0.4 mL, 20 mg/0.2 mL and 10 mg/0.1 mL
Single-Dose Prefilled Syringe

This Instructions for Use contains information on how to inject HUMIRA.
Before Injecting: Your healthcare provider should show you how to use HUMIRA before you use it for the first time. Call your healthcare provider or 1-800-4HUMIRA (1-800-448-6472) if you need help.

Important Information You Need to Know Before Injecting HUMIRA

Do not use the prefilled syringe and call your healthcare provider or pharmacist if:

- Liquid is cloudy, discolored, or has flakes or particles in it
- Expiration date has passed

- Liquid has been frozen (even if thawed) or left in direct sunlight
- The seals of the carton are broken or missing or if the prefilled syringe has been dropped or crushed

Keep the needle cover on until right before your injection.
How should I store HUMIRA?

- Store HUMIRA in the refrigerator between 36°F to 46°F (2°C to 8°C).
- Store HUMIRA in the original carton until use to protect it from light.
- Do not freeze.
- Refrigerated HUMIRA may be used until the expiration date printed on the HUMIRA carton, dose tray or prefilled syringe.
- If needed, for example when you are traveling, you may also store HUMIRA at room temperature up to 77°F (25°C) for up to 14 days.

- Throw away HUMIRA if it has been kept at room temperature and not used within 14 days.
- Record the date you first remove HUMIRA from the refrigerator in the spaces provided on the carton and dose tray.
- Do not store HUMIRA in extreme heat or cold.

Keep HUMIRA, injection supplies, and all other medicines out of the reach of children.
Read Instructions on All Pages Before Using the HUMIRA Single-Dose Prefilled Syringe

Take HUMIRA out of the refrigerator.
Leave HUMIRA at room temperature for 15 to 30 minutes before injecting.

- Do not remove the needle cover while allowing HUMIRA to reach room temperature.
- Do not warm HUMIRA in any other way. For example, do not warm it in a microwave or in hot water.
- Do not use the prefilled syringe if liquid has been frozen (even if thawed).

Check expiration date on the prefilled syringe label. Do not use the prefilled syringe if expiration date has passed.
Place the following on a clean, flat surface:

- 1 single-dose prefilled syringe and alcohol swab
- 1 cotton ball or gauze pad (not included)
- Puncture-resistant sharps disposal container (not included). See Step 9 at the end of this Instructions for Use for instructions on how to throw away (dispose of) your prefilled syringe

Wash and dry your hands.

Choose an injection site:

- On the front of your thighs or
- Your lower abdomen (belly) at least 2 inches from your navel (belly button)
- Different from your last injection site

Wipe the injection site in a circular motion with the alcohol swab and let it dry.

- Do not touch or blow on the injection site after it is cleaned. Allow the skin to dry before injecting.
- Do not inject through clothes.
- Do not inject into skin that is sore, bruised, red, hard, scarred, has stretch marks, or areas with psoriasis plaques.

Hold the prefilled syringe in one hand.
Gently pull the needle cover straight off with the other hand.

- Throw the needle cover away.
- Do not touch the needle with your fingers or let the needle touch anything.

Hold the prefilled syringe with the needle facing up.

- Hold the prefilled syringe at eye level with one hand so you can see the air in the prefilled syringe.
- Using your other hand, slowly push the plunger in to push the air out through the needle.
- You may see a drop of liquid at the end of the needle. This is normal.

Hold the body of the prefilled syringe in one hand between the thumb and pointer (index) fingers. Hold the prefilled syringe in your hand like a pencil.
Do not pull back on the plunger at any time.

Gently squeeze the area of cleaned skin at your injection site with your other hand. Hold the skin firmly.
Insert the needle into the skin at about a 45-degree angle using a quick, dart-like motion.

- After the needle is in, let go of the skin.

Slowly push the plunger all the way in until all of the liquid is injected and the prefilled syringe is empty.

When the injection is completed, slowly pull the needle out of the skin while keeping the prefilled syringe at the same angle.
After completing the injection, place a cotton ball or gauze pad on the skin of the injection site.

- Do not rub.
- Slight bleeding at the injection site is normal.

How should I throw away (dispose of) the used HUMIRA prefilled syringe?

- Put your used needles and syringes in a FDA-cleared sharps disposal container right away after use. Do not throw away (dispose of) loose needles and syringes in the household trash.
- If you do not have a FDA-cleared sharps disposal container, you may use a household container that is:
  ○ made of a heavy-duty plastic,
  ○ can be closed with a tight-fitting, puncture-resistant lid, without sharps being able to come out,
  ○ upright and stable during use,
  ○ leak-resistant, and
  ○ properly labeled to warn of hazardous waste inside the container.
- When your sharps disposal container is almost full, you will need to follow your community guidelines for the right way to dispose of your sharps disposal container. There may be state or local laws about how you should throw away used needles and syringes. For more information about safe sharps disposal, and for specific information about sharps disposal in the state that you live in, go to the FDA’s website at: http://www.fda.gov/safesharpsdisposal.
- Do not dispose of your used sharps disposal container in your household trash unless your community guidelines permit this. Do not recycle your used sharps disposal container.
- For the safety and health of you and others, needles and used syringes must never be re-used.

The needle cover, alcohol swab, cotton ball or gauze pad, dose tray, and packaging may be placed in your household trash.

Questions About Using the HUMIRA Single-Dose Prefilled Syringe
What if I have not received in-person training from a healthcare provider?

- Call your healthcare provider or 1-800-4HUMIRA (1-800-448-6472) or visit www.HUMIRA.com if you need help

Always keep the prefilled syringe and the sharps disposal container out of the reach of children.

Keep a record of the dates and locations of your injections. To help remember when to take HUMIRA, mark your calendar ahead of time.

This Instructions for Use has been approved by the U.S. Food and Drug Administration.

Revised 12/2025

Manufactured by AbbVie Inc. North Chicago, IL 60064 U.S.A.
US License Number 1889 20098764

PACKAGE LABEL

NDC 0074-0124-03

STARTER PACK FOR
CROHN’S DISEASE,
ULCERATIVE COLITIS, OR
HIDRADENITIS SUPPURATIVA
3 SINGLE-DOSE PREFILLED PENS
HUMIRA® PEN
adalimumab
80 mg/0.8 mL
FOR SUBCUTANEOUS USE ONLY
80mg/0.8 ml
29 GAUGE NEEDLE
EACH STERILE SINGLE-DOSE PREFILLED PEN CONTAINS:
Adalimumab..............80 mg
Mannitol.................33.6 mg
Polysorbate 80.........0.8 mg
Water for injection, USP
Sodium hydroxide added as necessary to adjust pH.
Contains no preservatives.
No U.S. standard of potency.
ATTENTION PHARMACIST: Each patient is required to receive the enclosed
Medication Guide.
Needle Cover for syringe is not made with natural rubber latex.
Carton contains:

- 3 dose trays (each containing 1 single-dose prefilled pen with 29 gauge 1/2 inch length fixed needle)
- 4 alcohol preps
- 1 package Insert
- 1 Medication Guide
- 1 Instructions for Use

The entire carton is to be dispensed as a unit.
Do not accept if seal is broken or missing.
Return to pharmacy if dose tray seal is broken or missing.
HUMIRA.COM
Rx only
abbvie

PACKAGE LABEL

NDC 0074-0124-04
STARTER PACK FOR
PEDIATRIC ULCERATIVE COLITIS
PATIENTS ≥ 40 kg
80 mg/0.8 mL
29 GAUGE NEEDLE
4 SINGLE-DOSE PREFILLED PENS
HUMIRA® PEN
adalimumab
80 mg/0.8 mL
FOR SUBCUTANEOUS USE ONLY
EACH STERILE SINGLE-DOSE PREFILLED PEN CONTAINS:
Adalimumab..............80 mg
Mannitol.................33.6 mg
Polysorbate 80.........0.8 mg
Water for injection, USP
Sodium hydroxide added as necessary to adjust pH.
Contains no preservatives.
No U.S. standard of potency.
ATTENTION PHARMACIST: Each patient is required to receive the enclosed
Medication Guide.
Needle Cover for syringe is not made with natural rubber latex.
Carton contains:

- 4 dose trays (each containing 1 single-dose prefilled pen with 29 gauge 1/2 inch length fixed needle)
- 4 alcohol preps
- 1 package Insert
- 1 Medication Guide
- 1 Instructions for Use

The entire carton is to be dispensed as a unit.
Do not accept if seal is broken or missing.
Return to pharmacy if dose tray seal is broken or missing.
HUMIRA.COM
Rx only
abbvie

PACKAGE LABEL

NDC 0074-0124-73
NOT FOR SALE
STARTER PACK FOR
CROHN’S DISEASE,
ULCERATIVE COLITIS, OR
HIDRADENITIS SUPPURATIVA
3 SINGLE-DOSE PREFILLED PENS
HUMIRA® PEN
adalimumab
80 mg/0.8 mL
FOR SUBCUTANEOUS USE ONLY
80 mg/0.8 ml
29 GAUGE NEEDLE
EACH STERILE SINGLE-DOSE PREFILLED PEN CONTAINS:
Adalimumab..............80 mg
Mannitol.................33.6 mg
Polysorbate 80.........0.8 mg
Water for injection, USP
Sodium hydroxide added as necessary to adjust pH.
Contains no preservatives.
No U.S. standard of potency.
ATTENTION PHYSICIAN: Each patient is required to receive the enclosed Medication Guide.
Needle Cover for syringe is not made with natural rubber latex.
Carton contains:

- 3 dose trays (each containing 1 single-dose prefilled pen with 29 gauge 1/2 inch length fixed needle)
- 4 alcohol preps
- 1 package Insert
- 1 Medication Guide
- 1 Instructions for Use

The entire carton is to be dispensed as a unit.
Do not accept if seal is broken or missing.
Return to physician if dose tray seal is broken or missing.
HUMIRA.COM
Rx only
abbvie

PACKAGE LABEL

NDC 0074-1539-03
PSORIASIS/UVEITIS
STARTER PACK
3 SINGLE-DOSE PREFILLED PENS
HUMIRA® PEN
adalimumab
ONE 80 mg/0.8 mL
TWO 40 mg/0.4 mL
FOR SUBCUTANEOUS USE ONLY
80 mg/0.8 ml
40 mg/0.4 ml
29 GAUGE NEEDLE
EACH 80 mg/0.8 mL STERILE SINGLE-DOSE PREFILLED PEN CONTAINS:
Adalimumab..............80 mg
Mannitol.................33.6 mg
Polysorbate 80..........0.8 mg
Water for injection, USP
EACH 40 mg/0.4 mL STERILE SINGLE-DOSE PREFILLED PEN CONTAINS:
Adalimumab..............40 mg
Mannitol.................16.8 mg
Polysorbate 80..........0.4 mg
Water for injection, USP
Contains no preservatives.
No U.S. standard of potency.
ATTENTION PHARMACIST: Each patient is required to receive the enclosed
Medication Guide.
Needle cover for syringe is not made with natural rubber latex.
Carton Contains:

- 3 dose trays (each containing 1 single-dose prefilled pen with 29 gauge 1/2 inch length fixed needle)
- 4 alcohol preps
- 1 package insert
- 1 Medication Guide
- 1 Instructions for Use

The entire carton is to be dispensed as a unit.
Do not accept if seal is broken or missing.
Store in carton until time of administration.
Return to pharmacy if dose tray seal is broken or missing.
HUMIRA.COM
Rx only
abbvie

PACKAGE LABEL

NDC 0074-0817-02
2 SINGLE-DOSE PREFILLED SYRINGES
HUMIRA®
adalimumab
10 mg/0.1 mL
FOR SUBCUTANEOUS USE ONLY
10 mg/0.1 mL
29 GAUGE NEEDLE
ATTENTION PHARMACIST: Each patient is required to receive the enclosed
Medication Guide.
Needle cover for syringe is not made with natural rubber latex. The entire carton is to be dispensed as a unit.
Return to pharmacy if dose tray seal is broken or missing.
THIS CARTON CONTAINS:

- 2 dose trays each containing 1 single-dose prefilled syringe with 29 gauge 1/2 inch length fixed needle.
- 2 alcohol preps
- 1 Medication Guide
- 1 package insert
- Instructions for Use

HUMIRA.com
Rx only
abbvie

PACKAGE LABEL

NDC 0074-0616-02
2 SINGLE-DOSE PREFILLED SYRINGES
HUMIRA®
adalimumab
20 mg/0.2 mL
FOR SUBCUTANEOUS USE ONLY
20 mg/0.2 mL
29 GAUGE NEEDLE
ATTENTION PHARMACIST: Each patient is required to receive the enclosed Medication Guide.
Needle cover for syringe is not made with natural rubber latex. The entire carton is to be dispensed as a unit.
Return to pharmacy if dose tray seal is broken or missing.
THIS CARTON CONTAINS:

- 2 dose trays (each containing 1 single-dose prefilled syringe with 29 gauge 1/2 inch length fixed needle)
- 2 alcohol preps
- 1 Medication Guide
- 1 package insert
- 1 Instructions for Use

Rx only
HUMIRA.com
abbvie

PACKAGE LABEL

NDC 0074-3799-02
2 Single-Dose Prefilled Syringes
HUMIRA®
adalimumab
40 mg/0.8 mL Syringe
FOR SUBCUTANEOUS USE ONLY
ATTENTION PHARMACIST: Each patient is required to receive the enclosed
Medication Guide.
Needle Cover for Syringe May Contain Dry Natural Rubber.
The entire carton is to be dispensed as a unit.
Return to pharmacy if dose tray seal is broken or missing.
This carton contains:

- 2 dose trays (each containing 1 single-dose prefilled syringe with 1/2 inch length fixed needle)
- 2 alcohol preps
- 1 Medication Guide
- 1 package insert
- 1 Instructions for Use

www.HUMIRA.com
Rx only
abbvie

PACKAGE LABEL

NDC 0074-3799-71
NOT FOR SALE
2 Single-Dose Prefilled Syringes
HUMIRA®
adalimumab
40 mg/0.8 mL Syringe
FOR SUBCUTANEOUS USE ONLY
ATTENTION PHYSICIAN: Each patient is required to receive the enclosed Medication Guide.
Needle Cover for Syringe May Contain Dry Natural Rubber.
The entire carton is to be dispensed as a unit.
Return to physician if dose tray seal is broken or missing.
This carton contains:

- 2 dose trays (each containing 1 single-dose prefilled syringe with 1/2 inch length fixed needle)
- 2 alcohol preps
- 1 Medication Guide
- 1 package insert
- 1 Instructions for Use

www.HUMIRA.com
Rx only
abbvie

PACKAGE LABEL

NDC 0074-9374-71
NOT FOR SALE
2 Single-Dose Prefilled Syringes
HUMIRA®
adalimumab
20 mg/0.4 mL Syringe
FOR SUBCUTANEOUS USE ONLY
ATTENTION PHYSICIAN: Each patient is required to receive the enclosed Medication Guide.
Needle Cover for Syringe May Contain Dry Natural Rubber.
The entire carton is to be dispensed as a unit. Return to physician if dose tray seal is broken or missing.
This carton contains:

- 2 dose trays (each containing 1 single-dose prefilled syringe with 1/2 inch length fixed needle)
- 2 alcohol preps
- 1 Medication Guide
- 1 package insert
- 1 Instructions for Use

www.HUMIRA.com
Rx only
abbvie

PACKAGE LABEL

NDC 0074-4339-02
2 SINGLE-DOSE PREFILLED PENS
HUMIRA® PEN
adalimumab
40 mg/0.8 mL
FOR SUBCUTANEOUS USE ONLY
ATTENTION PHARMACIST: Each patient is required to receive the enclosed Medication Guide.
Needle Cover for Syringe May Contain Dry Natural Rubber.
The entire carton is to be dispensed as a unit.
Return to pharmacy if dose tray seal is broken or missing.
This carton contains:

- 2 dose trays (each containing 1 single-dose prefilled pen with 1/2 inch length fixed needle)
- 2 alcohol preps
- 1 Medication Guide
- 1 package insert
- 1 Instructions for Use

www.Humira.com
Rx only
abbvie

PACKAGE LABEL

NDC 0074-4339-06
Starter Package for
- Crohn’s Disease, -
Ulcerative Colitis, or
- Hidradenitis Suppurativa
HUMIRA® PEN
(adalimumab)
40 mg/0.8 mL
FOR SUBCUTANEOUS USE ONLY
6 Single-Dose Prefilled Pens
Each Sterile Single-Dose
Prefilled Pen contains:
Adalimumab................................................. 40 mg
Sodium chloride...........................................4.93 mg
Monobasic sodium phosphate dihydrate........0.69 mg
Dibasic sodium phosphate dihydrate.............1.22 mg
Sodium citrate.............................................0.24 mg
Citric acid monohydrate...............................1.04 mg
Mannitol.......................................................9.6 mg
Polysorbate 80..............................................0.8 mg
Water for injection
Sodium hydroxide added as necessary to adjust pH.
Contains no preservatives.
No U.S. standard of potency.
Medication Guide for patient enclosed.
Needle Cover for Syringe May Contain Dry Natural Rubber.
Carton contains 6 dose trays (each containing 1 single-dose prefilled pen with 1/2 inch length fixed needle), 6 alcohol preps, 1 Package Insert, 1 Medication Guide and Instructions for Use.
The entire carton is to be dispensed as a unit.
Do not accept if seal is broken or missing.
Return to pharmacy if dose tray seal is broken or missing.
www.HUMIRA.com
Rx only
abbvie

PACKAGE LABEL

NDC 0074-4339-71
NOT FOR SALE
2 SINGLE-DOSE PREFILLED PENS
HUMIRA® PEN
adalimumab
40 mg/0.8 mL
FOR SUBCUTANEOUS USE ONLY
ATTENTION PHYSICIAN: Each patient is required to receive the enclosed Medication Guide.
Needle Cover for Syringe May Contain Dry Natural Rubber.
The entire carton is to be dispensed as a unit.
Return to physician if dose tray seal is broken or missing.
This carton contains:

- 2 dose trays (each containing 1 single-dose prefilled pen with 1/2 inch length fixed needle)
- 2 alcohol preps
- 1 Medication Guide
- 1 package insert
- 1 Instructions for Use

www.HUMIRA.com
Rx only
abbvie

PACKAGE LABEL

NDC 0074-4339-73
NOT FOR SALE
Starter Package for
- Crohn’s Disease,
- Ulcerative Colitis, or
- Hidradenitis Suppurativa
HUMIRA® PEN
(adalimumab)
40 mg/0.8 mL
FOR SUBCUTANEOUS USE ONLY
6 Single-Dose Prefilled Pens
Each Sterile Single-Dose
Prefilled Pen Contains:
Adalimumab.................................................40 mg
Sodium chloride.........................................4.93 mg
Monobasic sodium phosphate dihydrate.......0.69 mg
Dibasic sodium phosphate dihydrate............1.22 mg
Sodium citrate............................................0.24 mg
Citric acid monohydrate..............................1.04 mg
Mannitol......................................................9.6 mg
Polysorbate 80.............................................0.8 mg
Water for injection.
Sodium hydroxide added as necessary to adjust pH.
Contains no preservatives.
No U.S. standard of potency.
Medication Guide for patient enclosed.
Needle Cover for Syringe May Contain Dry Natural Rubber.
Carton contains 6 dose trays (each containing
1 single-dose prefilled pen with 1/2 inch length
fixed needle), 6 alcohol preps, 1 Package Insert,
1 Medication Guide and Instructions for Use.
The entire carton is to be dispensed as a unit.
Do not accept if seal is broken or missing.
Return to physician if dose tray seal is broken or missing.
www.HUMIRA.com
Rx only
abbvie

PACKAGE LABEL

NDC 0074-0243-02
2 SINGLE-DOSE PREFILLED SYRINGES
40 mg/0.4 mL
29 GAUGE NEEDLE
HUMIRA®
adalimumab
40 mg/0.4 mL
FOR SUBCUTANEOUS USE ONLY
ATTENTION PHARMACIST: Each patient is required to receive the enclosed Medication Guide.
Needle cover for syringe is not made with natural rubber latex. The entire carton is to be dispensed as a unit.
Return to pharmacy if dose tray seal is broken or missing.
THIS CARTON CONTAINS:

- 2 dose trays (each containing 1 single-dose prefilled syringe with 29 gauge 1/2 inch length fixed needle)
- 2 alcohol preps
- 1 Medication Guide
- 1 package insert
- 1 Instructions for Use

HUMIRA.com
Rx only
abbvie

PACKAGE LABEL

NDC 0074-0554-01
1 SINGLE-DOSE PREFILLED PEN
29 GAUGE NEEDLE
HUMIRA® PEN
adalimumab
40 mg/0.4 mL
FOR SUBCUTANEOUS USE ONLY
ATTENTION PHARMACIST: Each patient is required
to receive the enclosed Medication Guide.
The entire carton is to be dispensed as a unit.
Return to pharmacy if dose tray seal is broken or missing.
THIS CARTON CONTAINS:

- 1 dose tray (containing 1 single-dose prefilled pen with 29 gauge 1/2 inch length fixed needle)
- 2 alcohol preps
- 1 Medication Guide
- 1 package insert
- 1 Instructions for Use

HUMIRA.COM
Rx only
abbvie

PACKAGE LABEL

NDC 0074-0554-02
2 SINGLE-DOSE PREFILLED PENS
HUMIRA® PEN
adalimumab
40 mg/0.4 mL
FOR SUBCUTANEOUS USE ONLY
40 mg/0.4 mL
29 GAUGE NEEDLE
ATTENTION PHARMACIST: Each patient is required
to receive the enclosed Medication Guide.
The entire carton is to be dispensed as a unit.
Return to pharmacy if dose tray seal is broken or missing.
THIS CARTON CONTAINS:

- 2 dose trays (each containing 1 single-dose prefilled pen
  with 29 gauge 1/2 inch length fixed needle)
- 2 alcohol preps • 1 Medication Guide • 1 package insert • 1 Instructions for Use

HUMIRA.COM
Rx only
abbvie

PACKAGE LABEL

NDC 0074-0554-74
NOT FOR SALE
1 SINGLE-DOSE PREFILLED PEN
29 GAUGE NEEDLE
HUMIRA® PEN
adalimumab
40 mg/0.4 mL
FOR SUBCUTANEOUS USE ONLY
ATTENTION PHYSICIAN: Each patient is required
to receive the enclosed Medication Guide.
The entire carton is to be dispenses as a unit.
Return to physician if dose tray seal is broken or missing.
THIS CARTON CONTAINS:

- 1 dose tray (containing 1 single-dose prefilled pen
  with 29 gauge 1/2 inch length fixed needle)
- 2 alcohol preps
- 1 Medication Guide
- 1 package insert
- 1 Instructions for Use

HUMIRA.COM
Rx only
abbvie

PACKAGE LABEL

NDC 0074-2540-01
1 SINGLE-DOSE PREFILLED SYRINGE
HUMIRA®
Adalimumab
80 mg/0.8 mL
FOR SUBCUTANEOUS USE ONLY
80 mg/0.8 mL
29 GAUGE NEEDLE
ATTENTION PHARMACIST: Each patient is required to receive the enclosed Medication Guide.
Needle cover for syringe is not made with natural rubber latex. The entire carton is to be dispensed as a unit.
Return to pharmacy if dose tray seal is broken or missing.
THIS CARTON CONTAINS:

- 1 dose tray (containing 1 single-dose prefilled syringe with 29 gauge 1/2 inch length fixed needle)
- 2 alcohol preps
- 1 Medication Guide
- 1 package insert
- 1 Instructions for Use

HUMIRA.com
Rx only
abbvie

PACKAGE LABEL

NDC 0074-2540-03
PEDIATRIC CROHN’S DISEASE
STARTER PACK
FOR PEDIATRIC PATIENTS ≥40 kg
3 SINGLE-DOSE PREFILLED SYRINGES
HUMIRA®
Adalimumab
80 mg/0.8 mL
FOR SUBCUTANEOUS USE ONLY
80 mg/0.8 mL
29 GAUGE NEEDLE
Each 80 mg/0.8 mL STERILE SINGLE-DOSE PREFILLED SYRINGE CONTAINS:
Adalimumab..................................................80 mg
Mannitol.......................................................33.6 mg
Polysorbate 80..............................................0.8 mg
Water for injection, USP
Contains no preservatives
No U.S. standard of potency
ATTENTION PHARMACIST: Each patient is required to receive the enclosed
Medication Guide.
Needle cover for syringe is not made with natural rubber latex.
Carton Contains:

- 3 dose trays (each containing 1 single-dose prefilled syringe with 29 gauge 1/2 inch length fixed needle)
- 4 alcohol preps
- 1 package insert
- 1 Medication Guide
- 1 Instructions for Use

The entire carton is to be dispensed as a unit.
Do not accept if seal is broken or missing.
Return to pharmacy if dose tray seal is broken or missing.
HUMIRA.com
Rx only
abbvie

PACKAGE LABEL

NDC 0074-0067-02
PEDIATRIC CROHN’S DISEASE
STARTER PACK
FOR PEDIATRIC PATIENTS < 40 kg
80 mg/0.8 mL
40 mg/0.4 mL
29 GAUGE NEEDLE
2 SINGLE-DOSE PREFILLED SYRINGES
HUMIRA®
Adalimumab
One 80 mg/0.8 mL
One 40 mg/0.4 mL
FOR SUBCUTANEOUS USE ONLY
EACH 80 mg/0.8 mL STERILE SINGLE-DOSE PREFILLED SYRINGE CONTAINS
Adalimumab..................................................80 mg
Mannitol.......................................................33.6 mg
Polysorbate 80..............................................0.8 mg
Water for injection, USP
EACH 40 mg/0.4 mL STERILE SINGLE-DOSE PREFILLED SYRINGE CONTAINS:
Adalimumab..................................................40 mg
Mannitol.......................................................16.8 mg
Polysorbate 80..............................................0.4 mg
Water for injection, USP
Contains no preservatives.
No U.S. standard of potency.
ATTENTION PHARMACIST: Each patient is required to receive the enclosed
Medication Guide.
Needle cover for syringe is not made with natural rubber latex.
Carton Contains:

- 2 dose trays (each containing 1 single-dose prefilled syringe with 29 gauge 1/2 inch length fixed needle)
- 2 alcohol preps
- 1 package insert
- 1 Medication Guide
- 1 Instructions for Use

The entire carton is to be dispensed as a unit.
Do not accept if seal is broken or missing.
Return to pharmacy if dose tray seal is broken or missing.
HUMIRA.com
Rx only
abbvie

PACKAGE LABEL

NDC 0074–0124–02
2 SINGLE-DOSE PREFILLED PENS
HUMIRA® PEN
adalimumab
80 mg/0.8 mL
FOR SUBCUTANEOUS USE ONLY
80 mg/0.8 mL
29 GAUGE NEEDLE
ATTENTION PHARMACIST: Each patient is required to receive the enclosed
Medication Guide.
Needle cover for syringe is not made with natural rubber latex.
The entire carton is to be dispensed as a unit.
Return to pharmacy if dose tray seal is broken or missing.
THIS CARTON CONTAINS:

- 2 dose trays (each containing 1 single-dose prefilled pen with 29 gauge 1/2 inch length fixed needle)
- 2 alcohol preps
- 1 Medication Guide
- 1 package insert
- 1 Instructions for Use

HUMIRA.COM
Rx only
abbvie